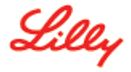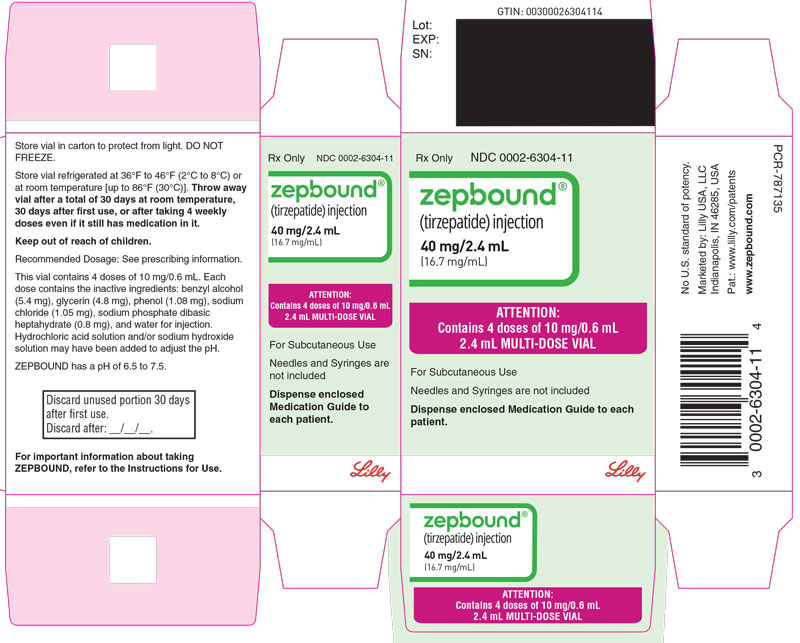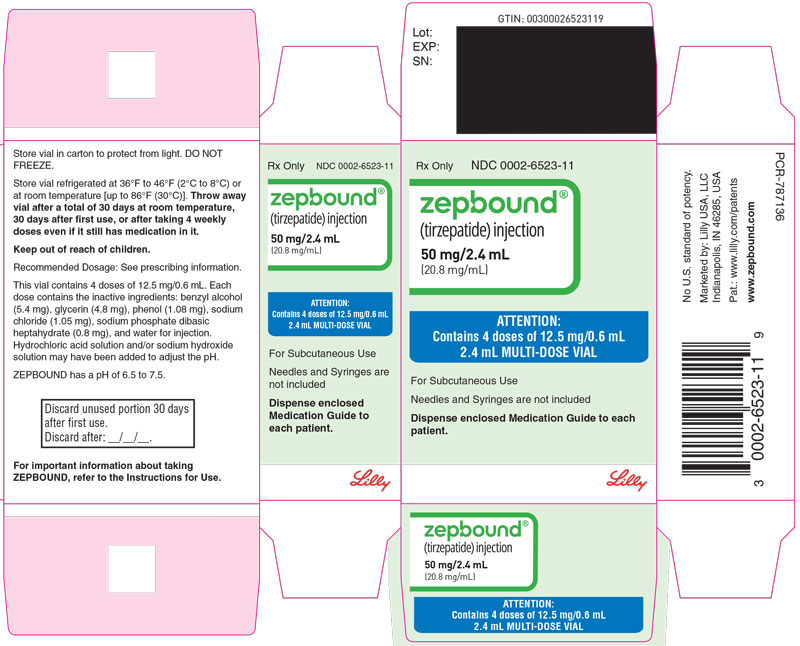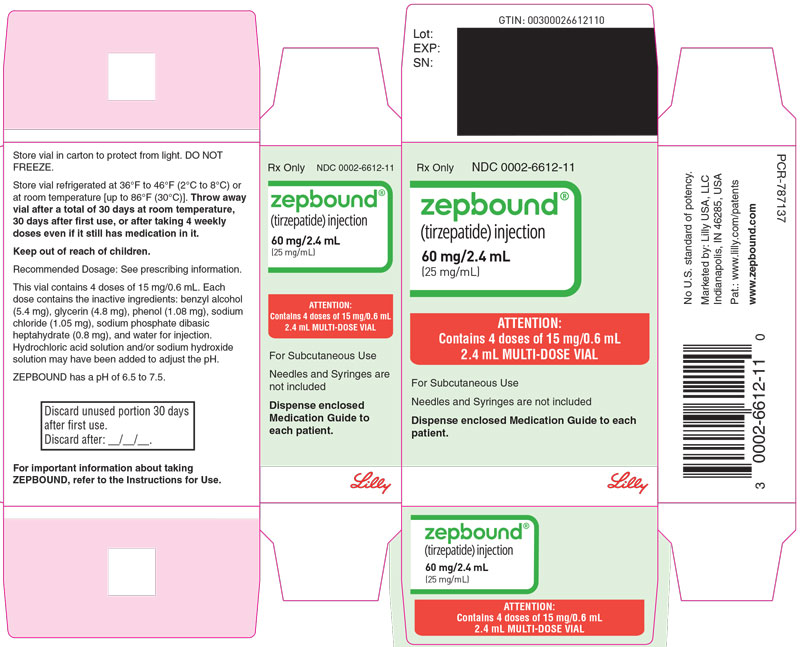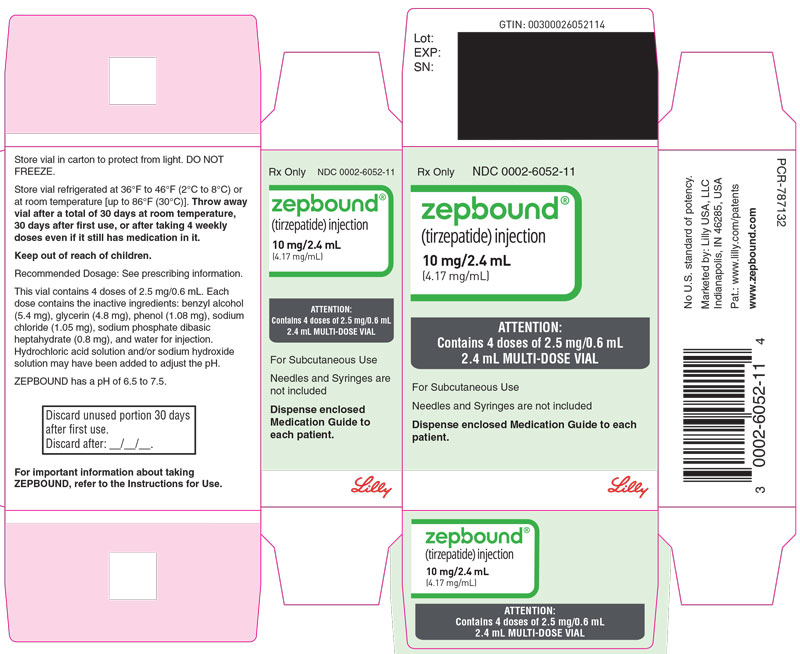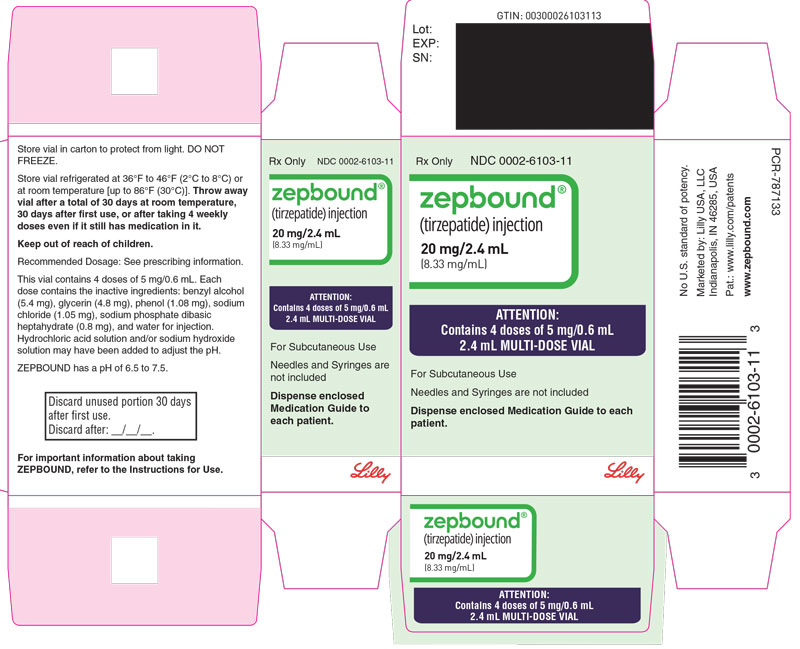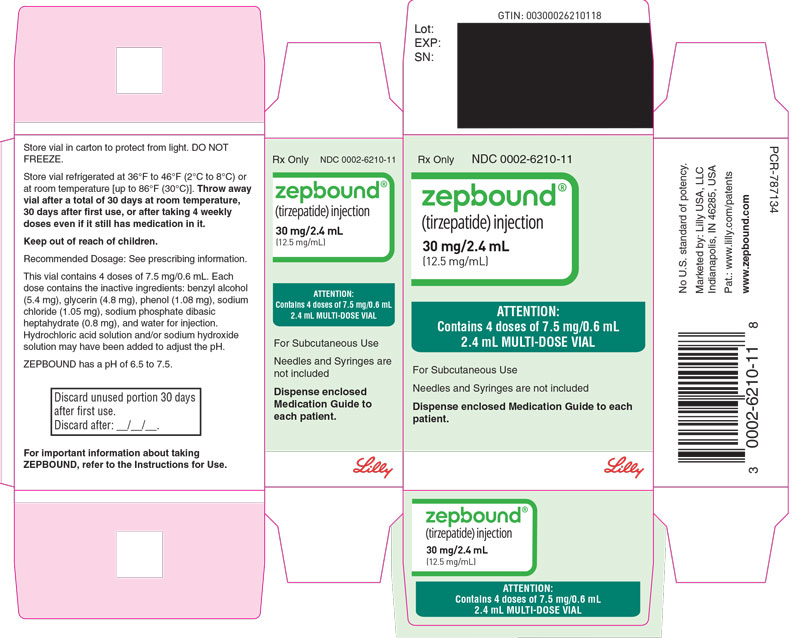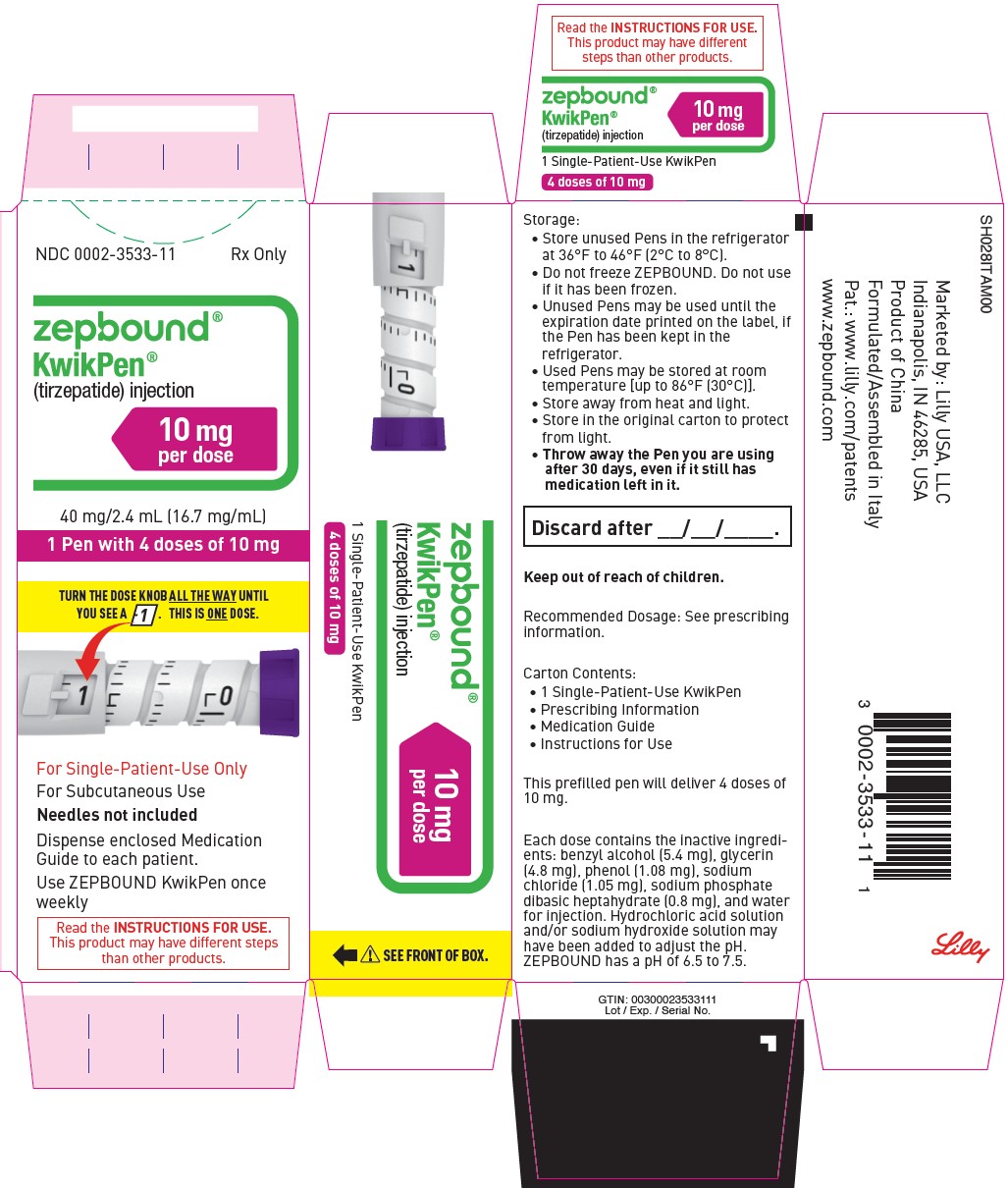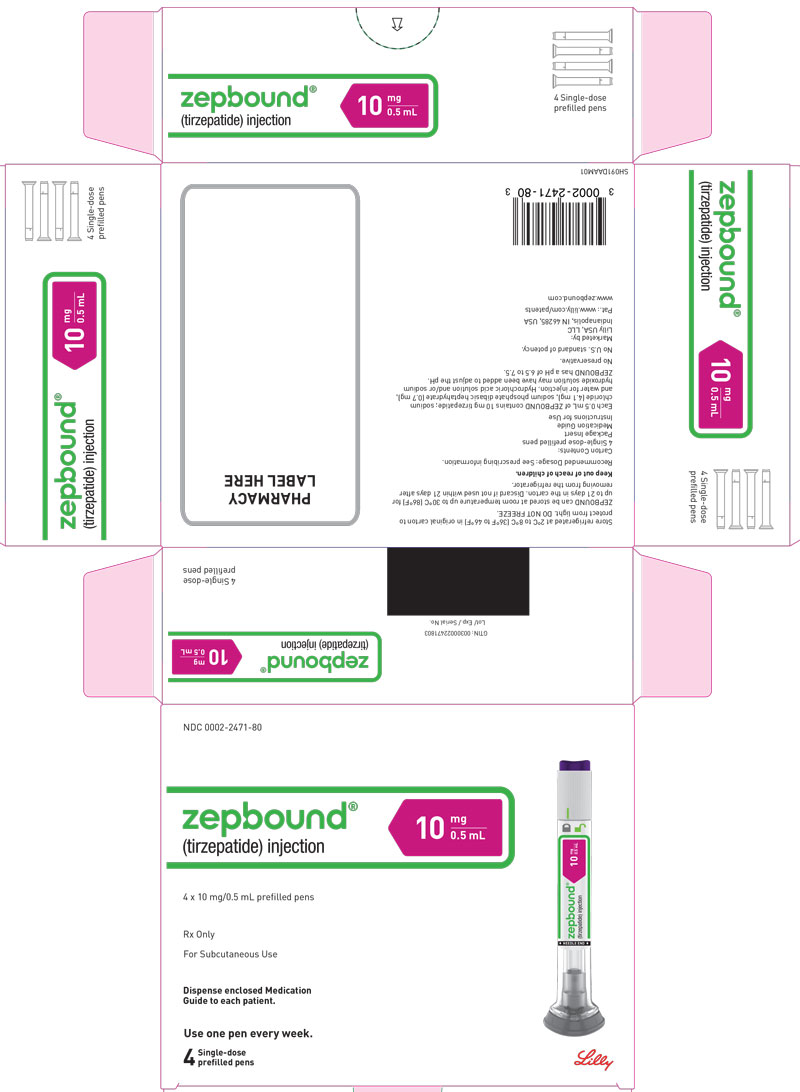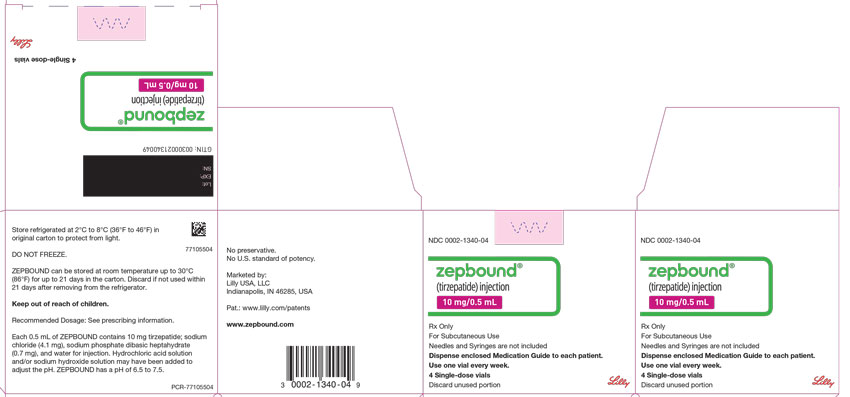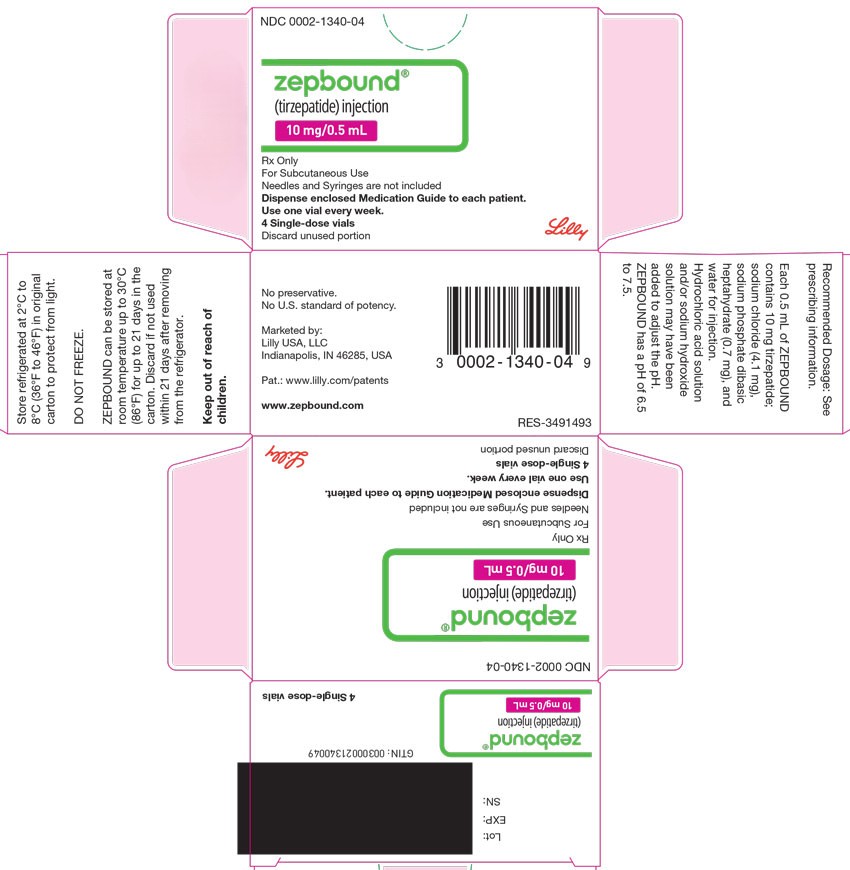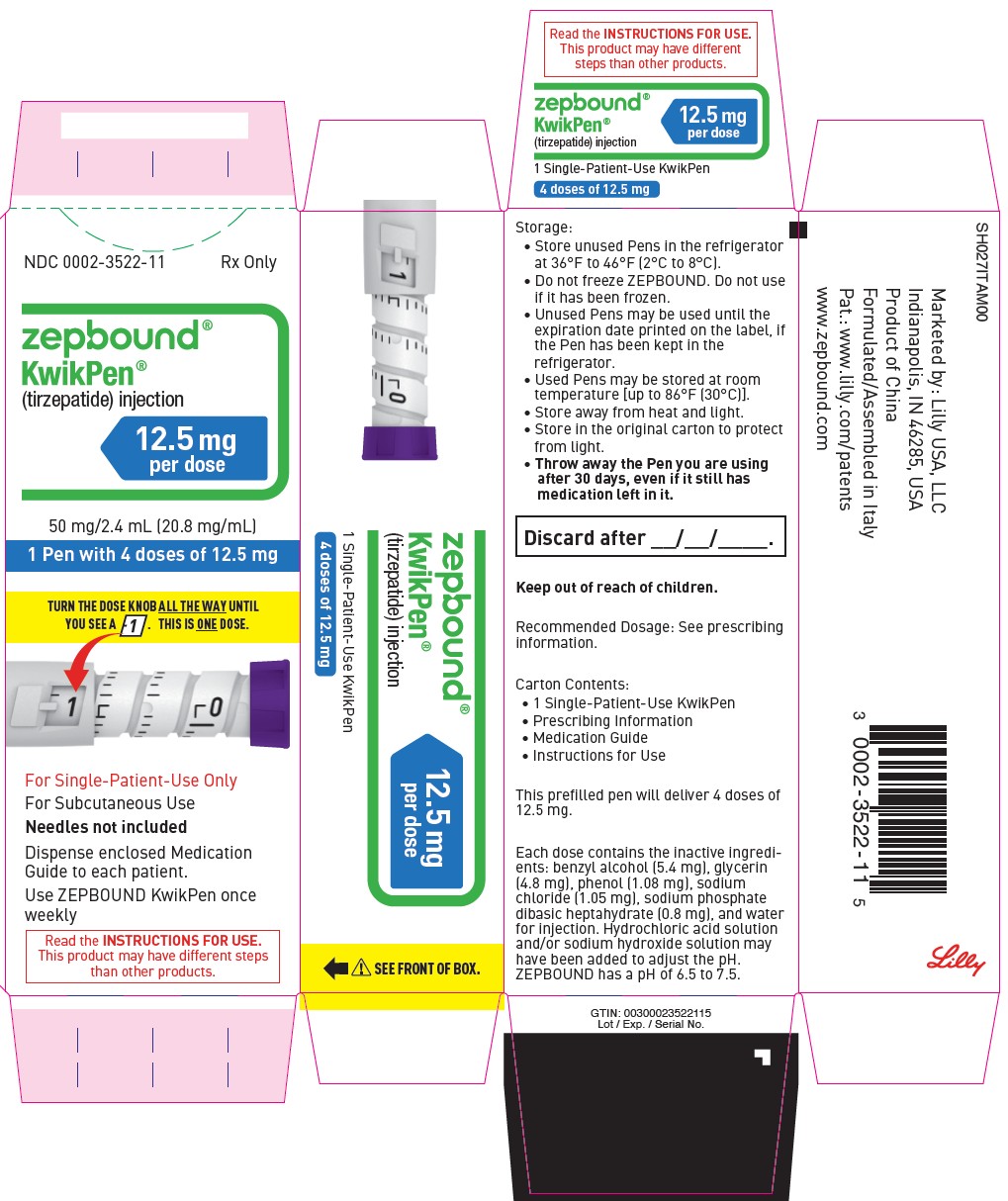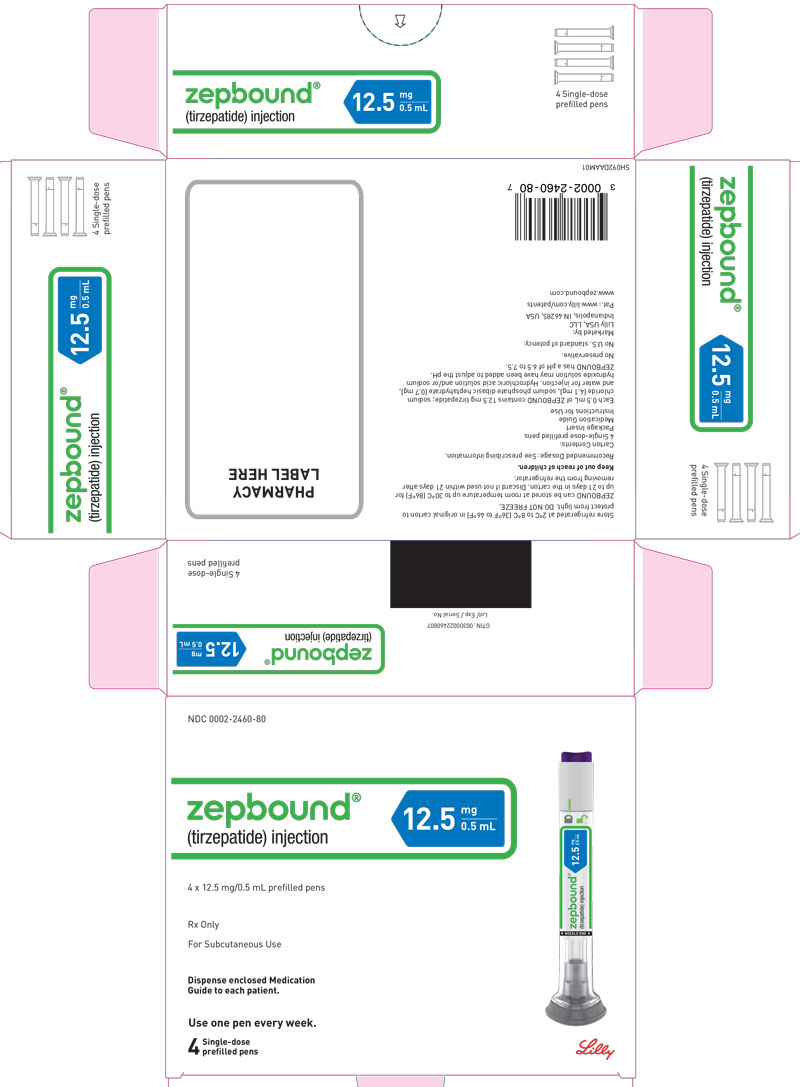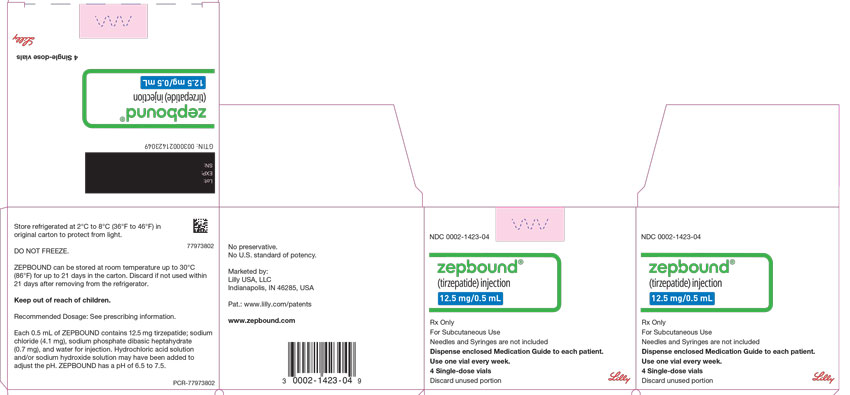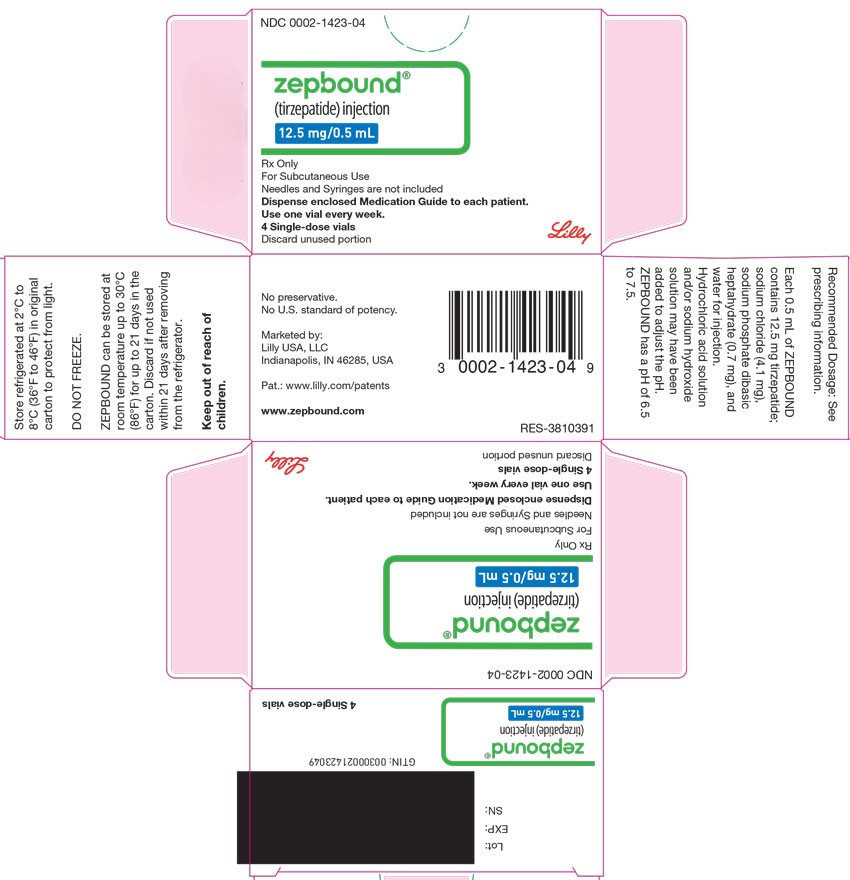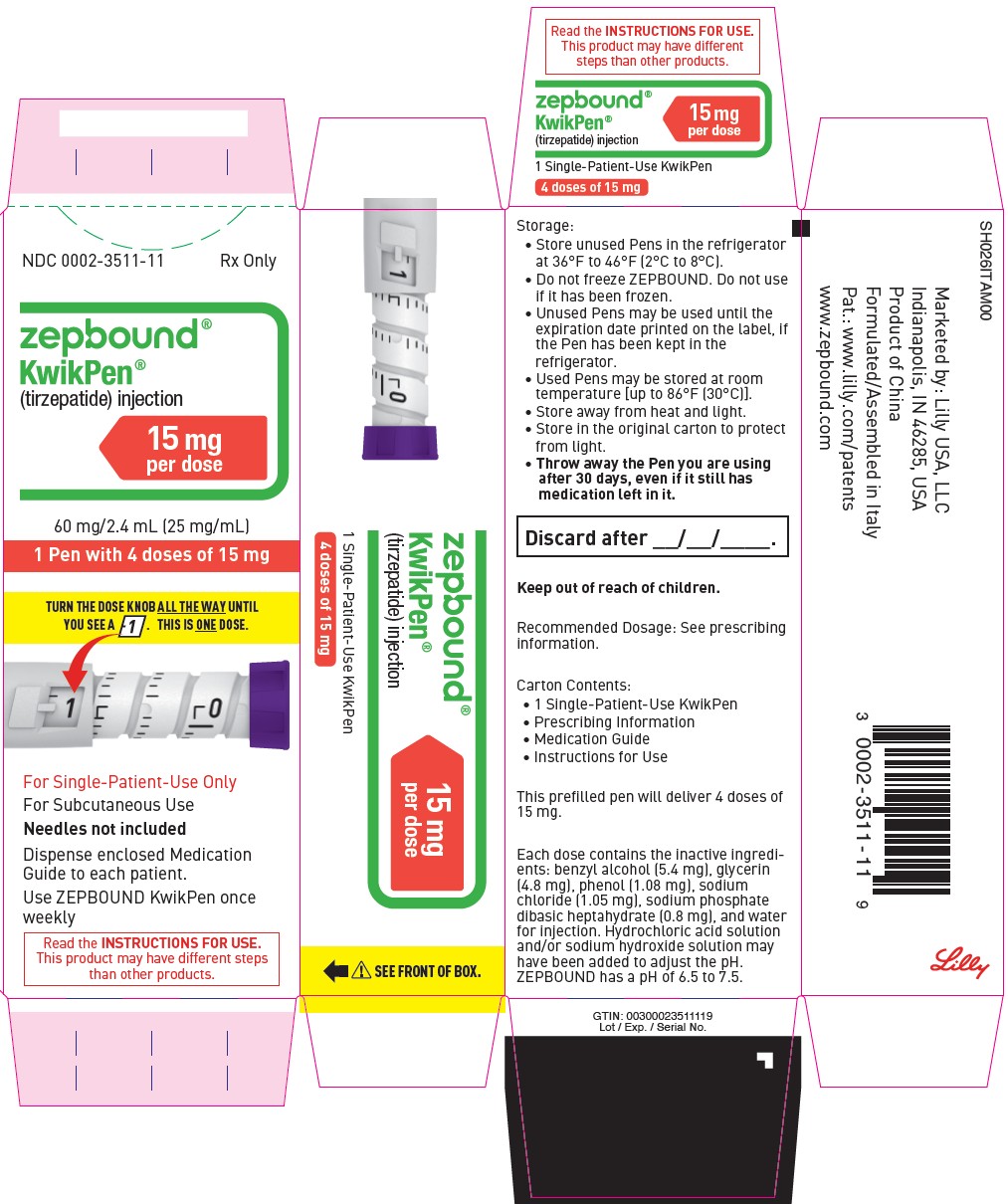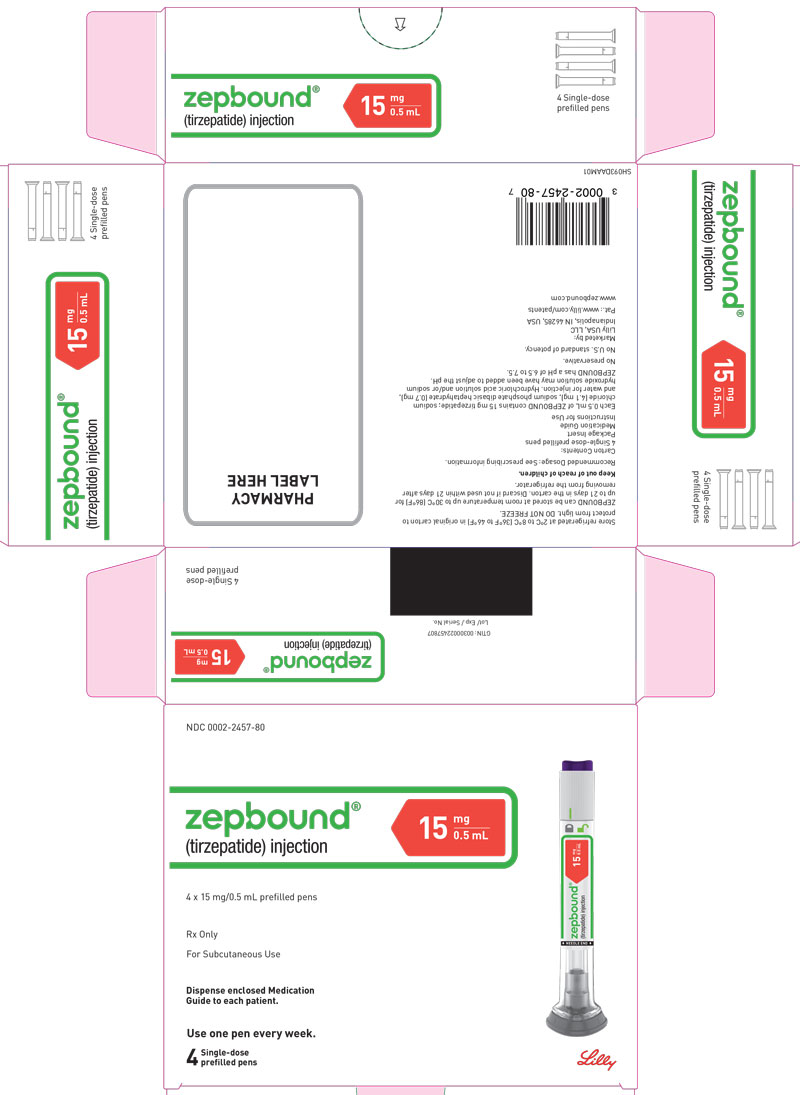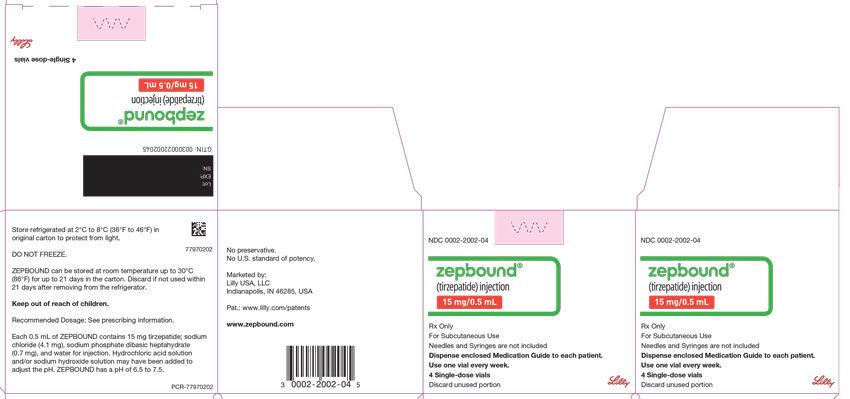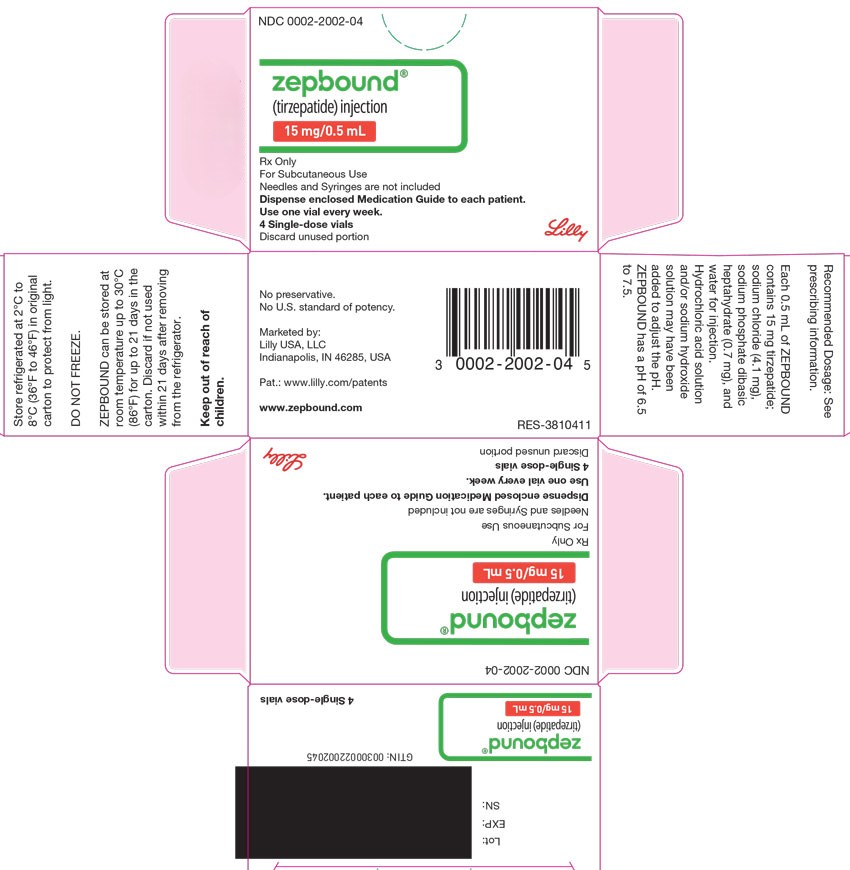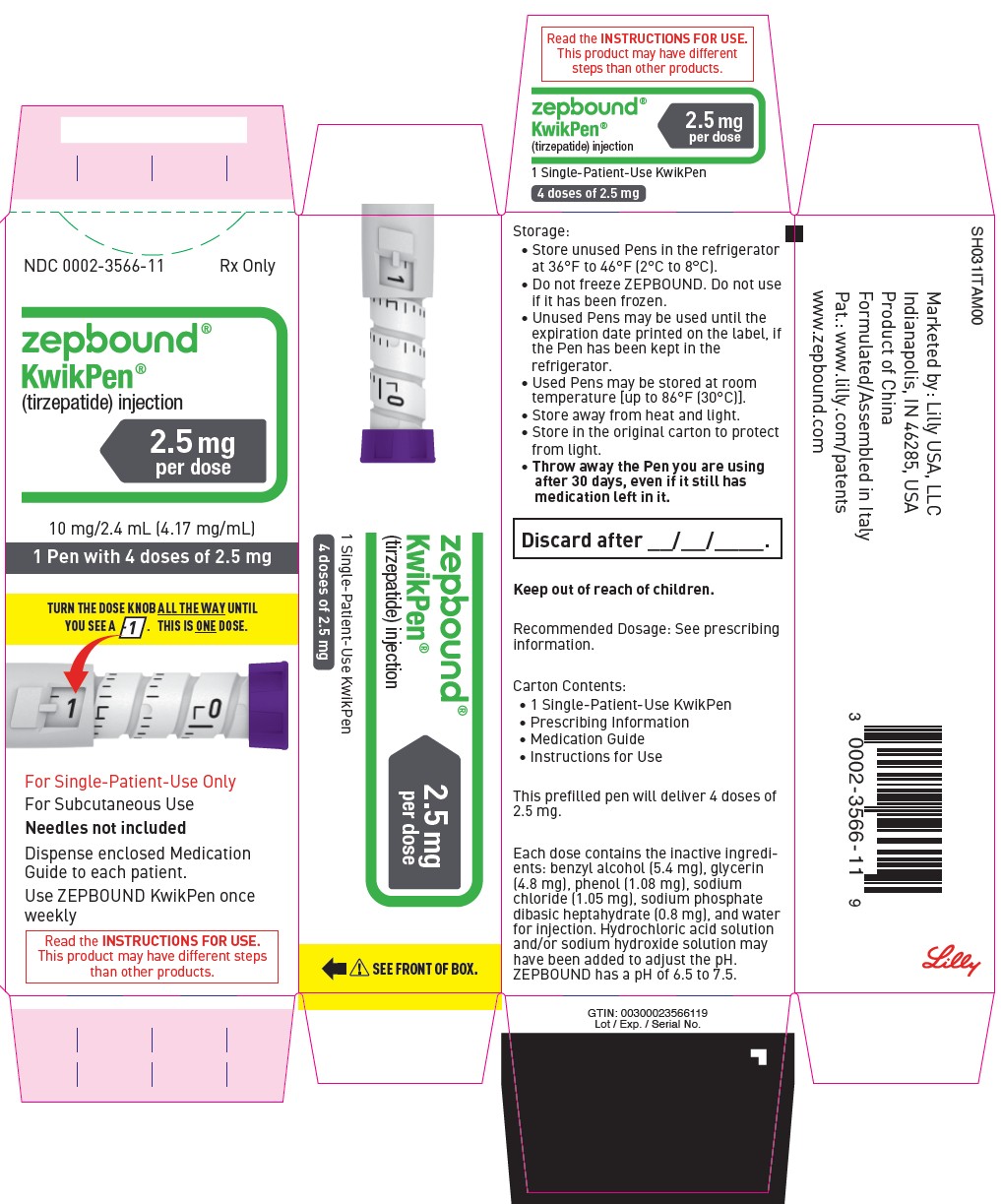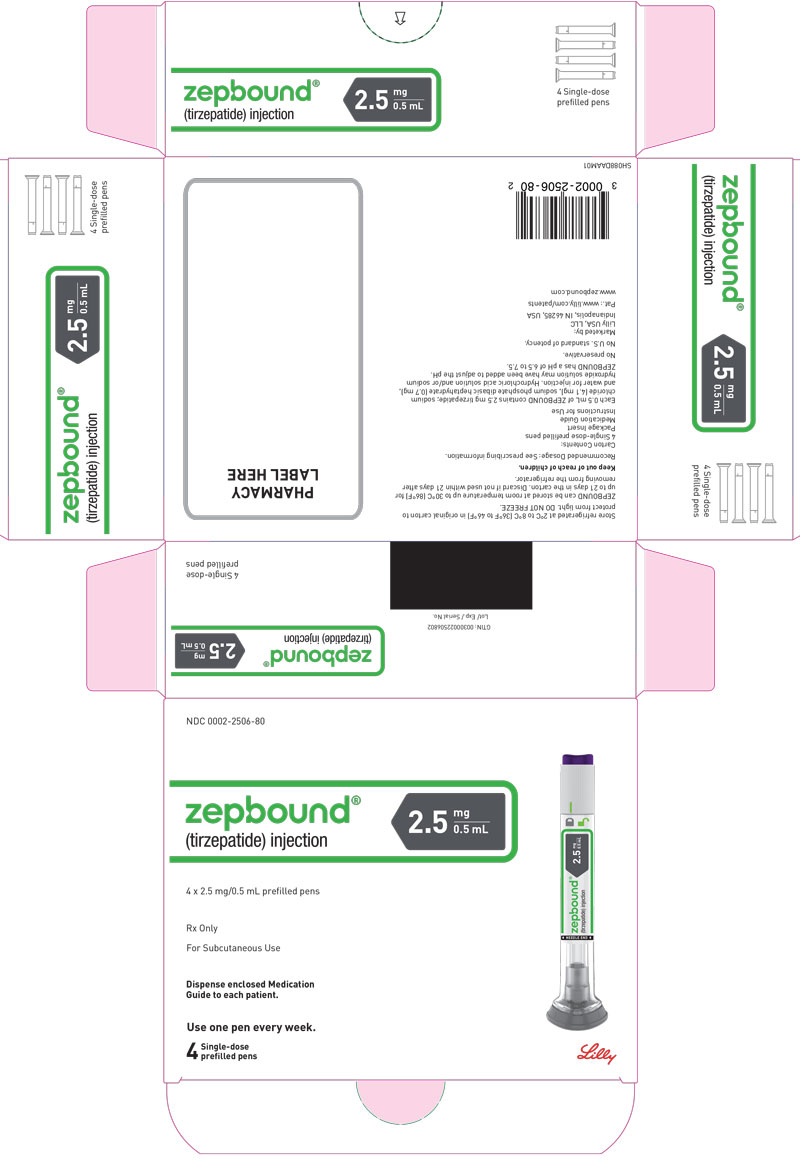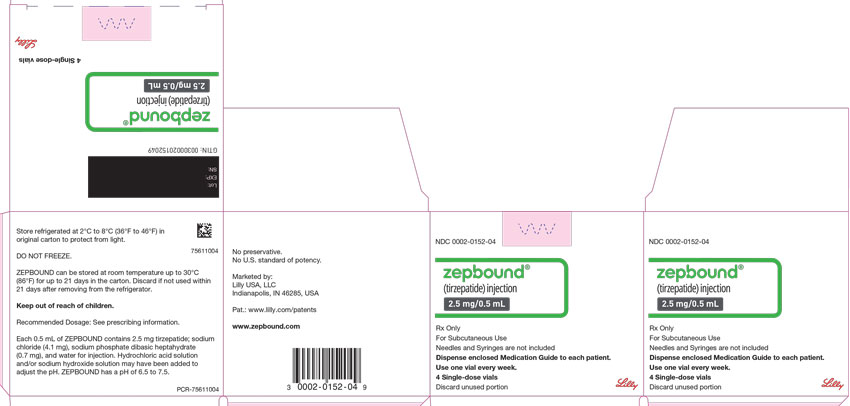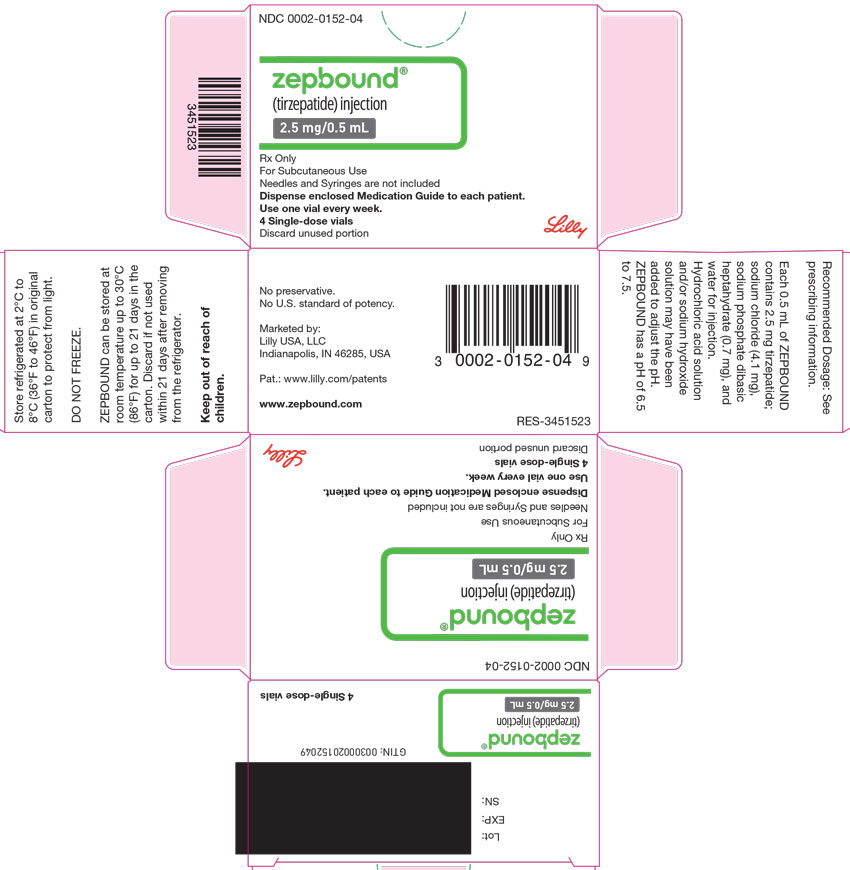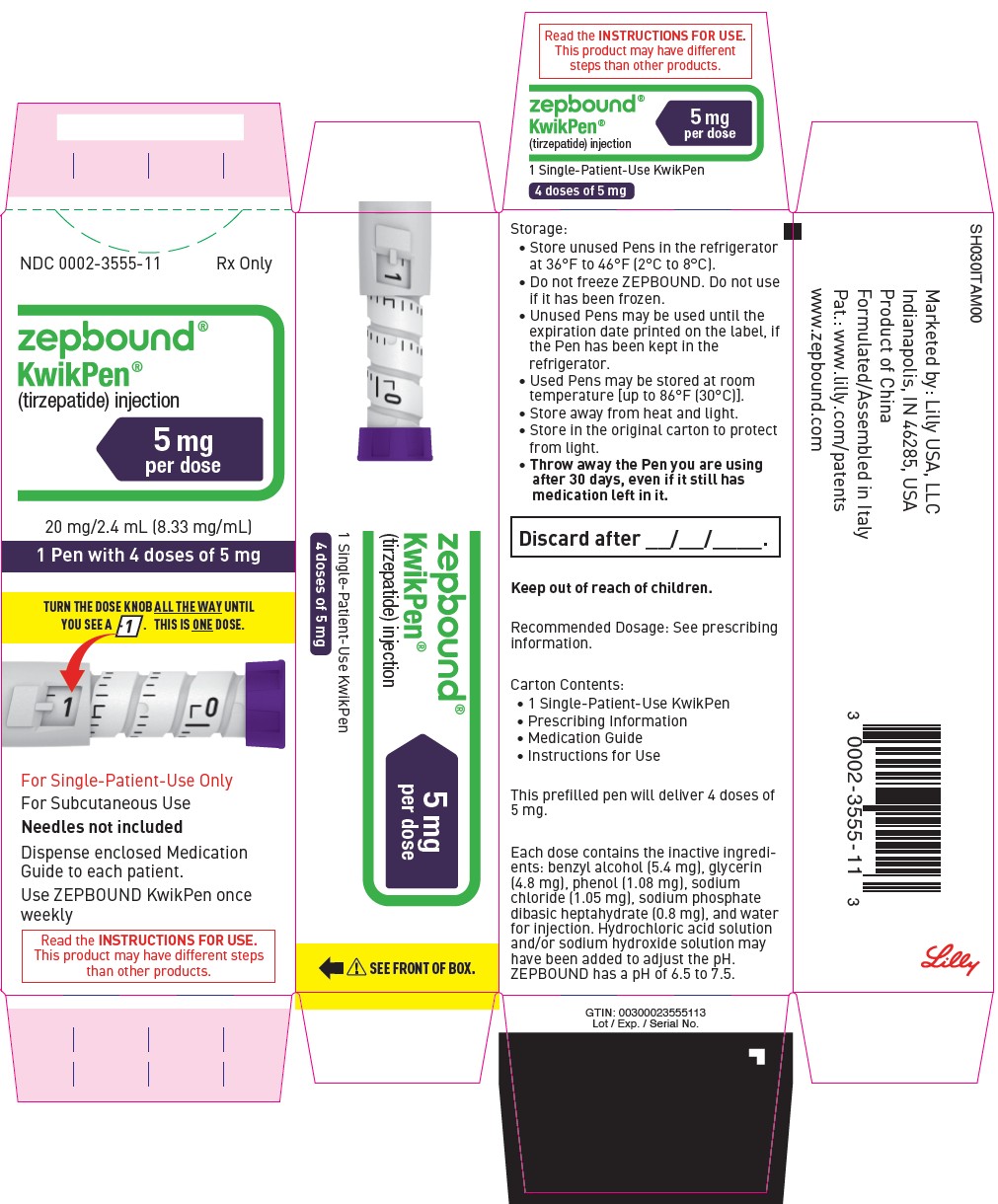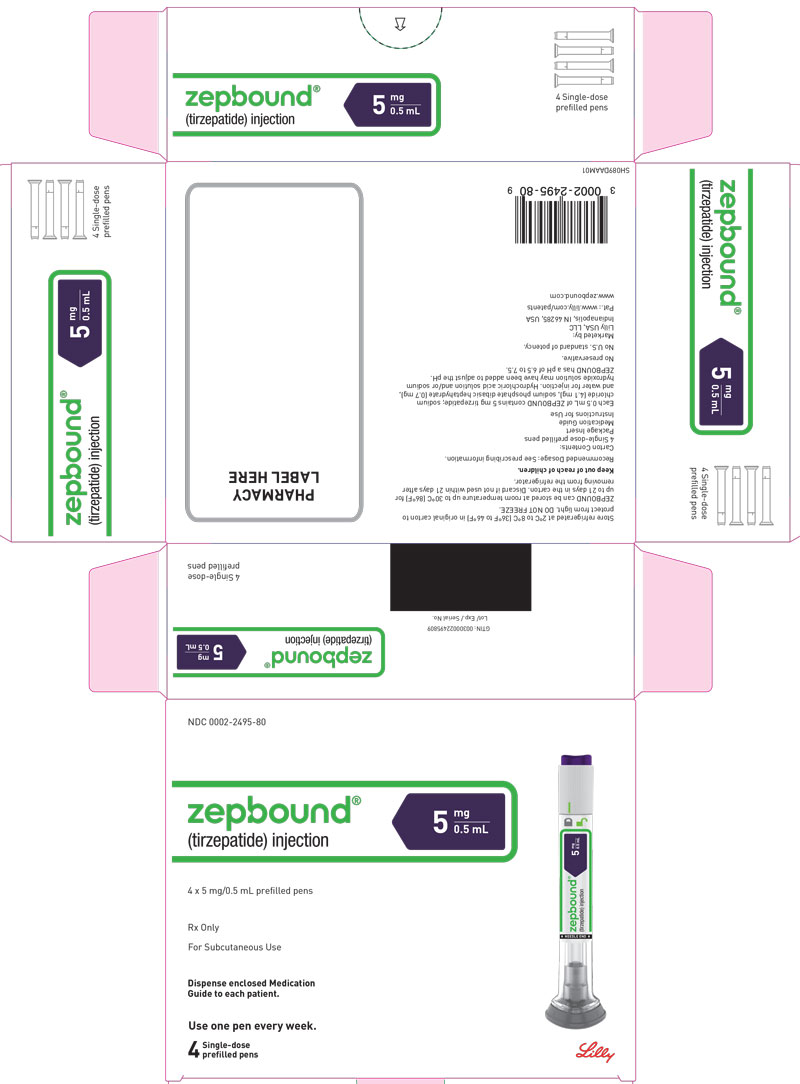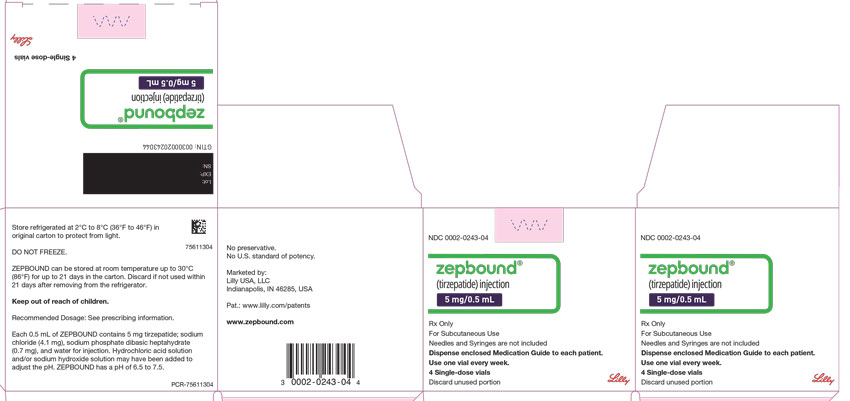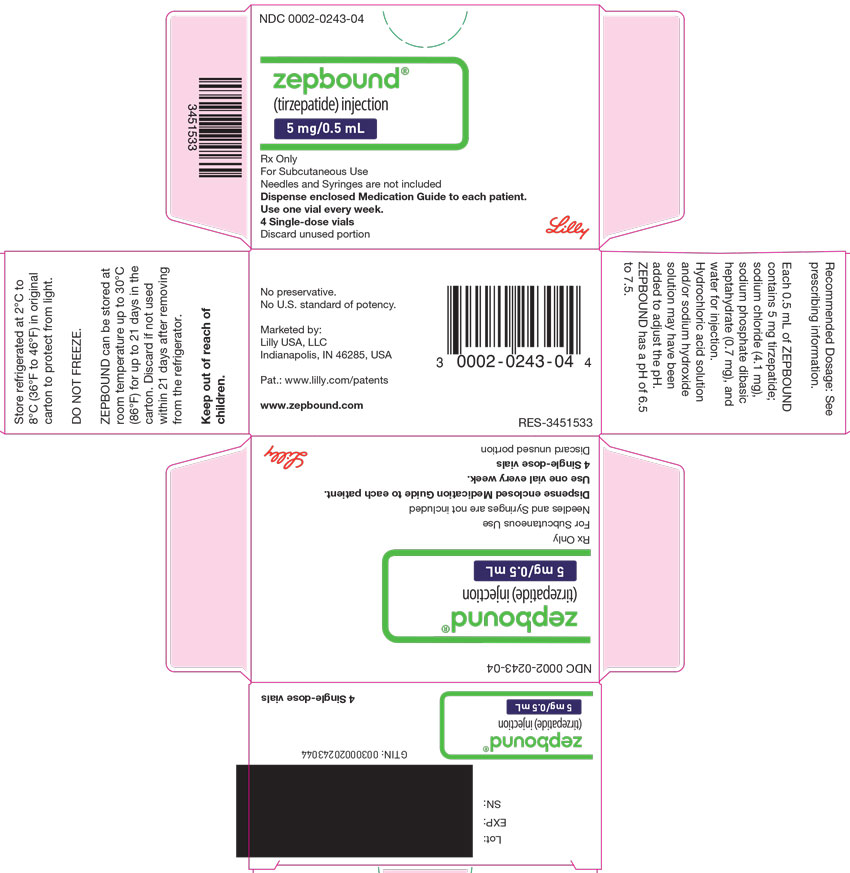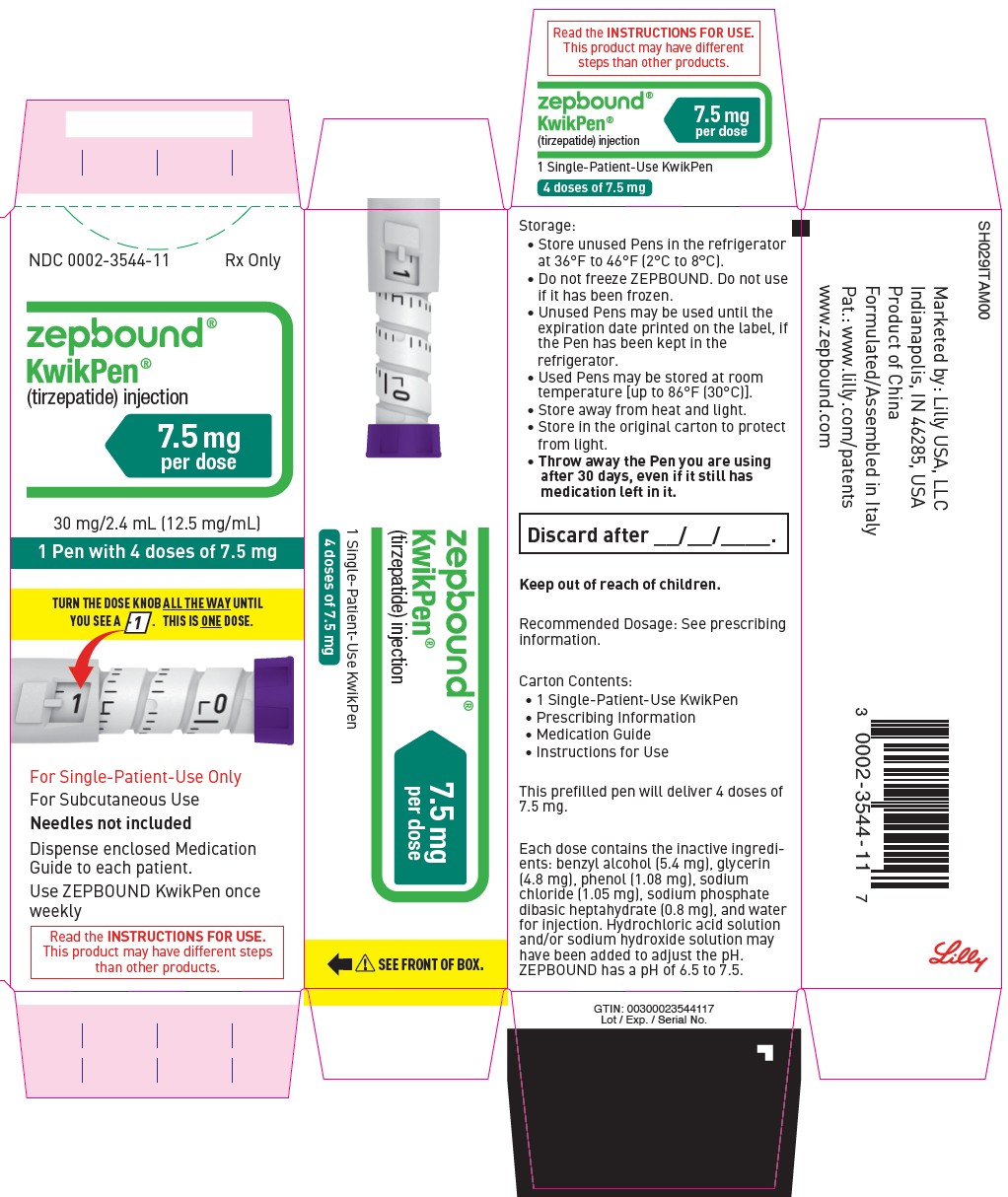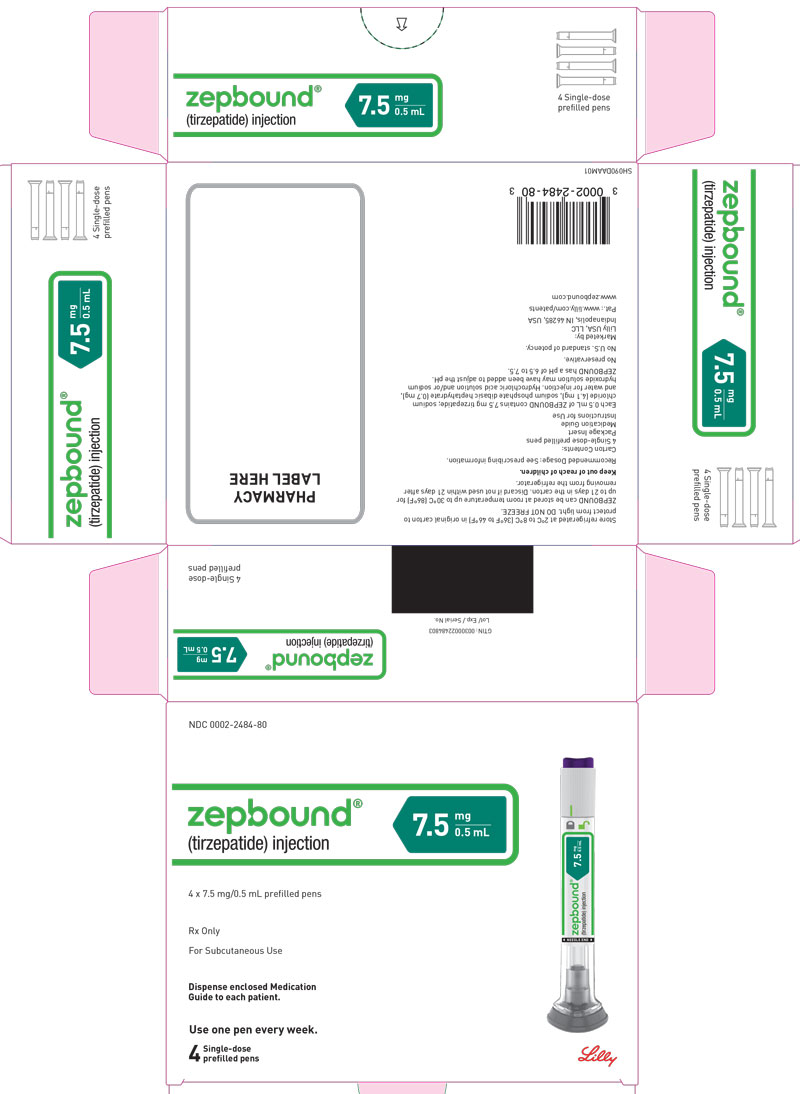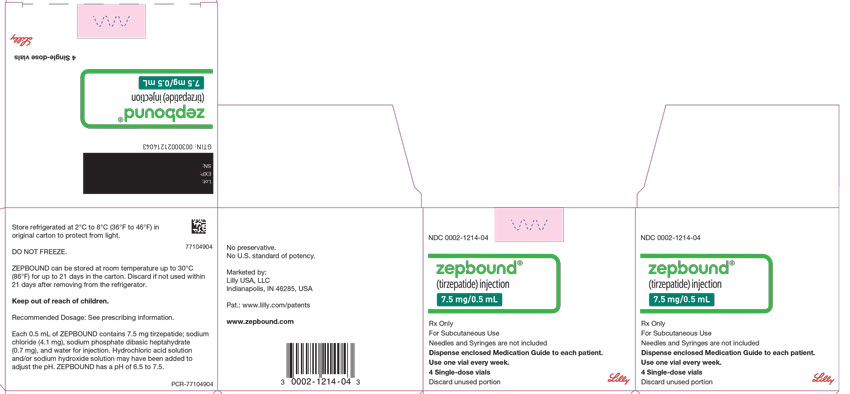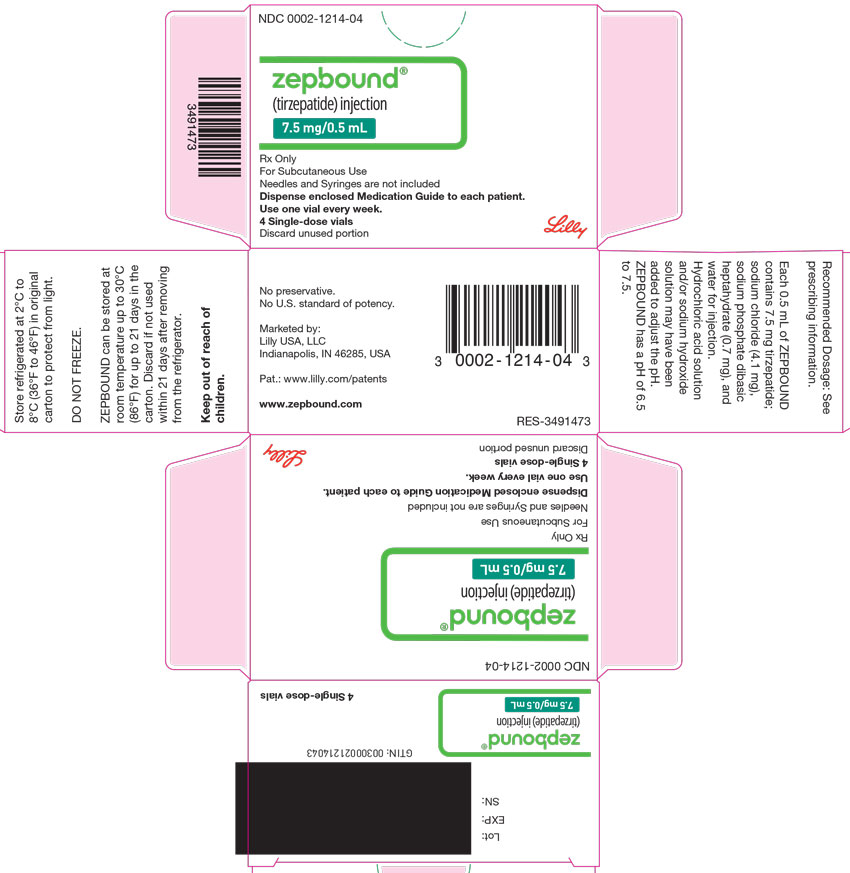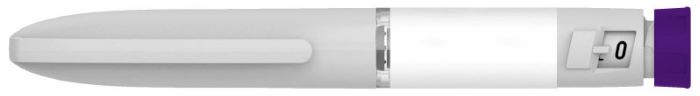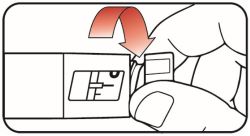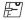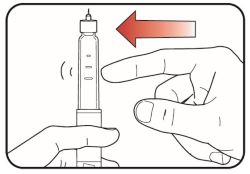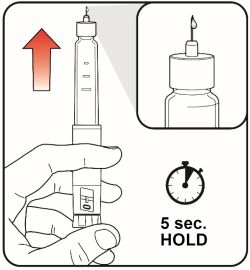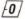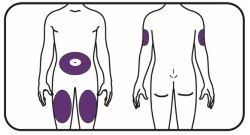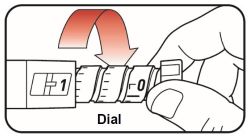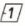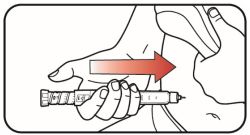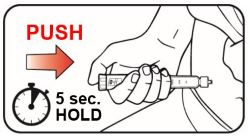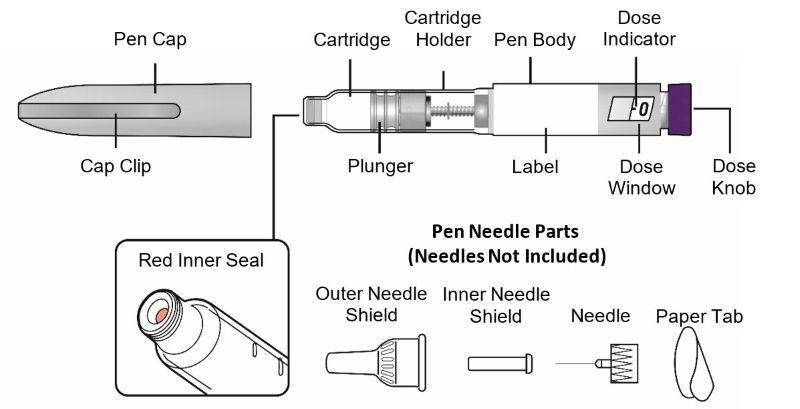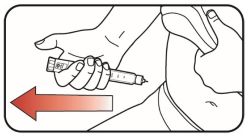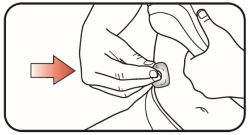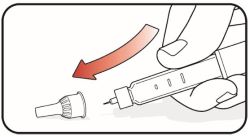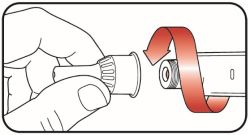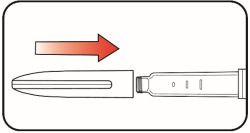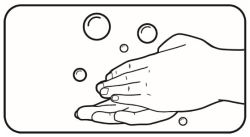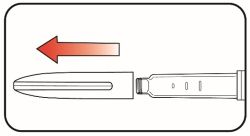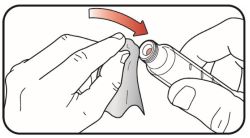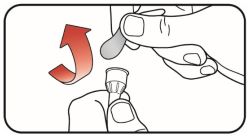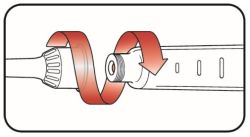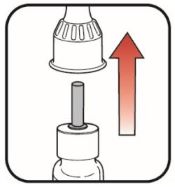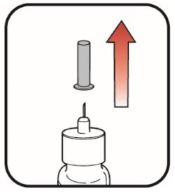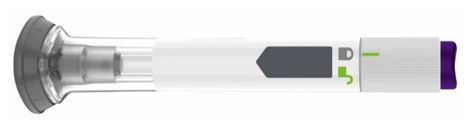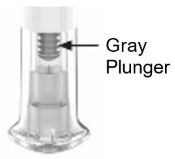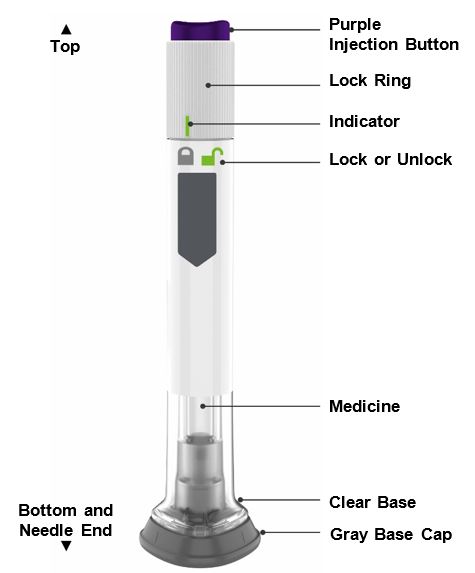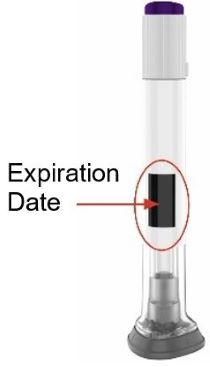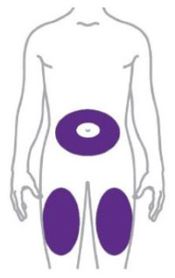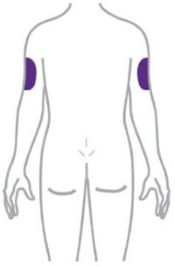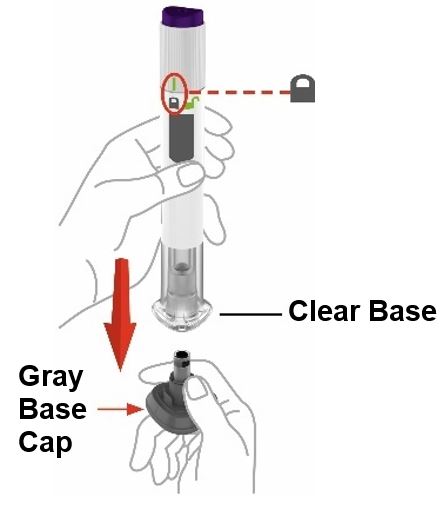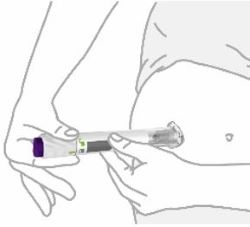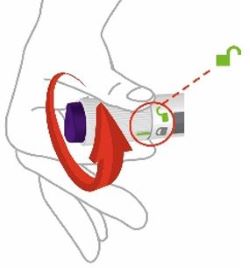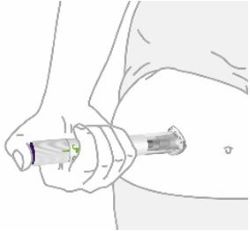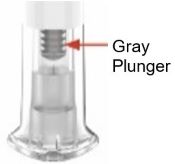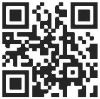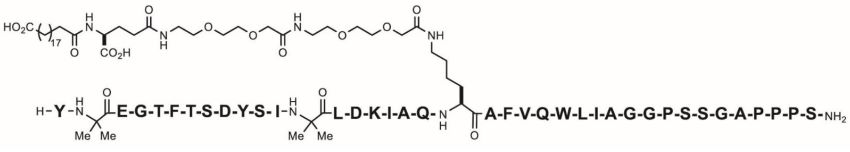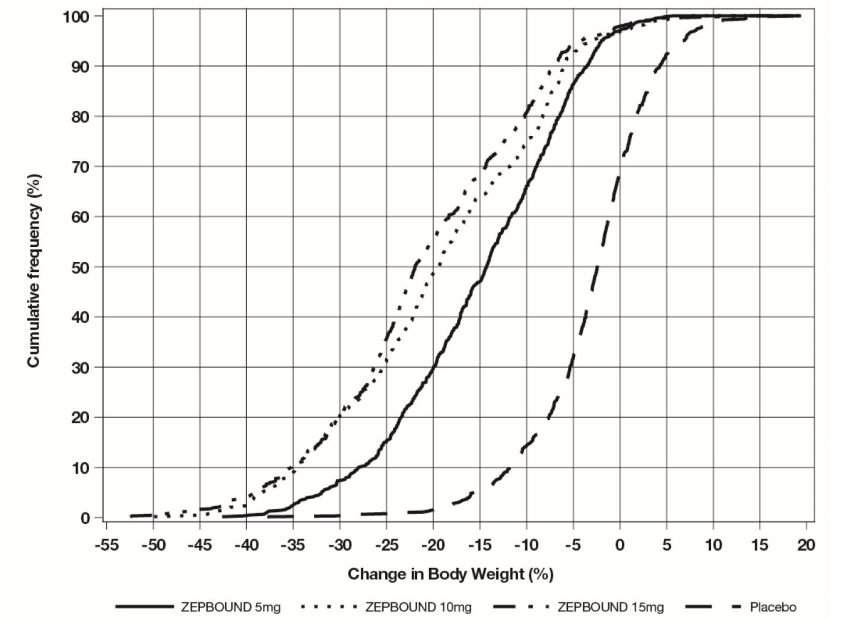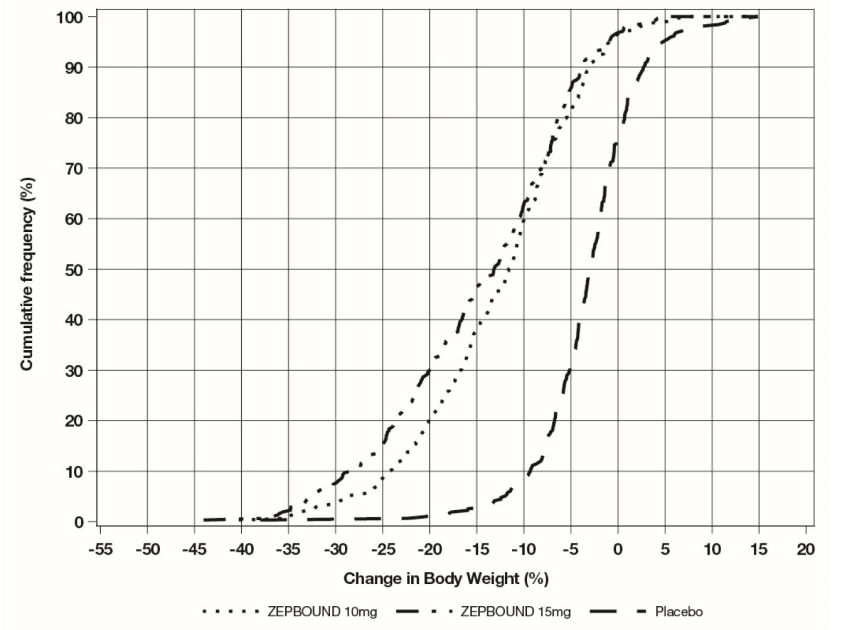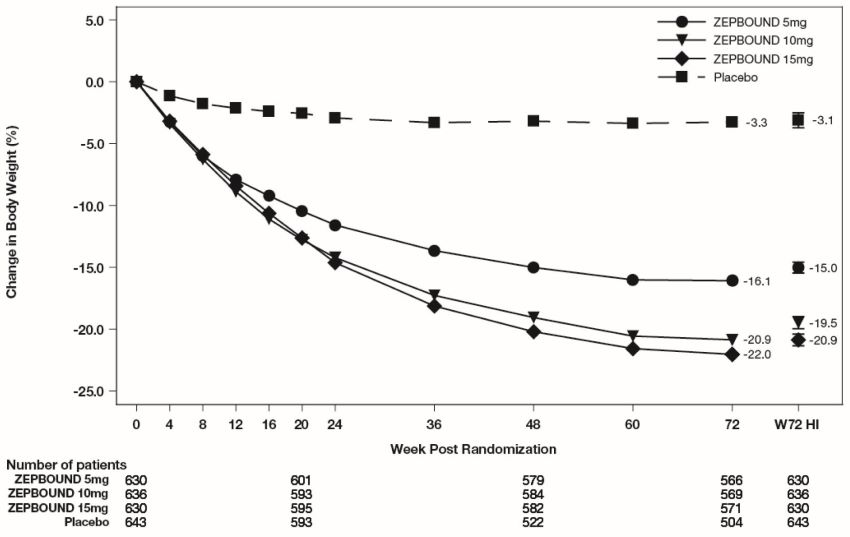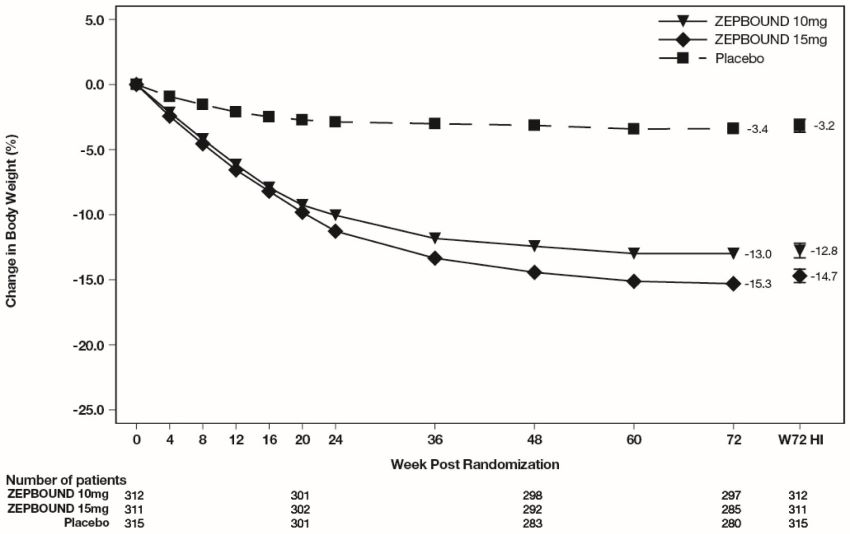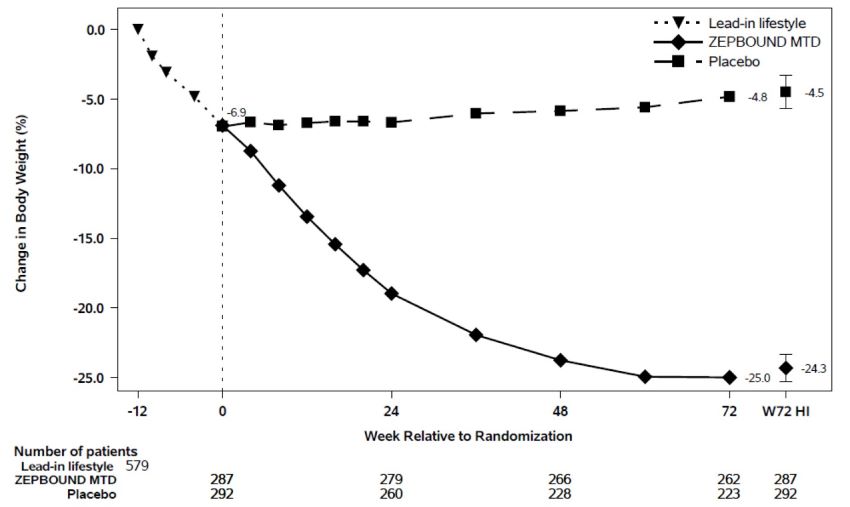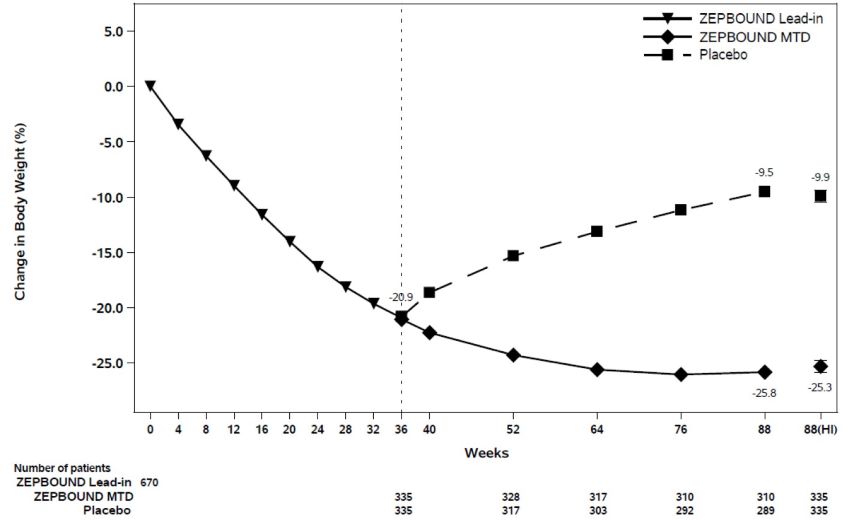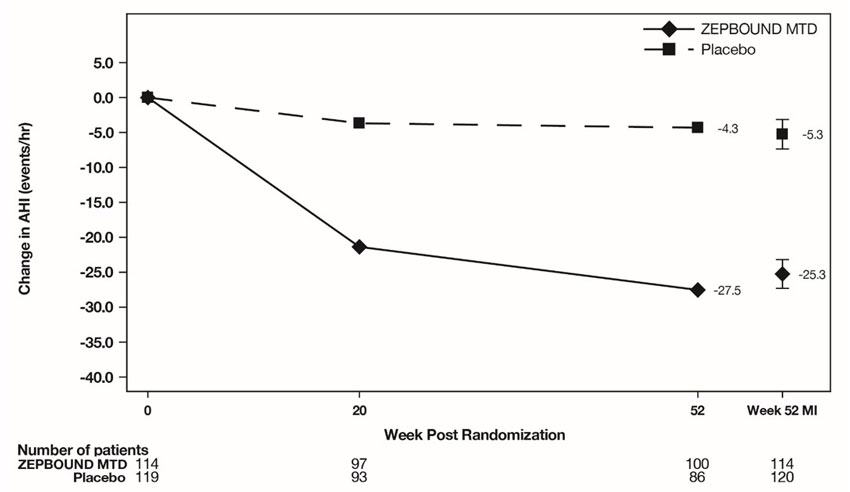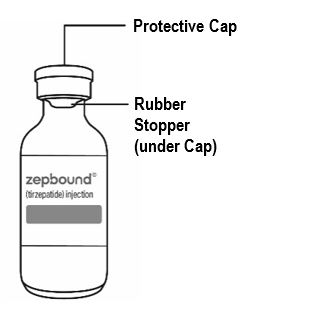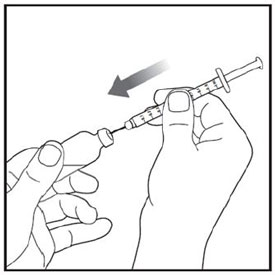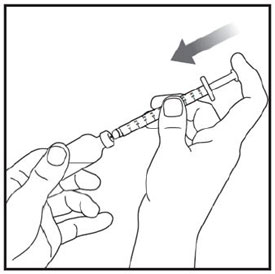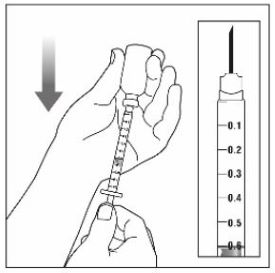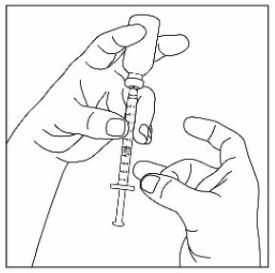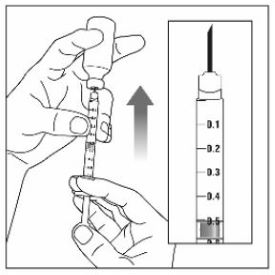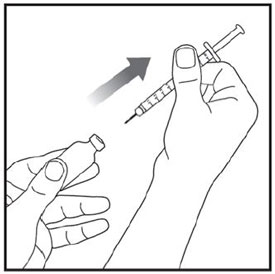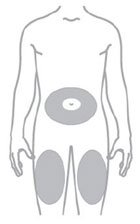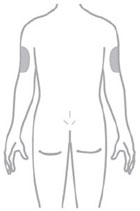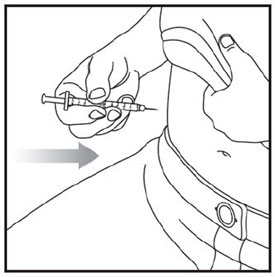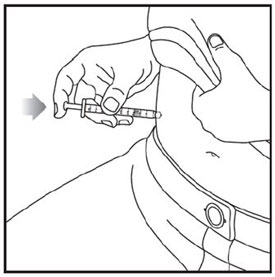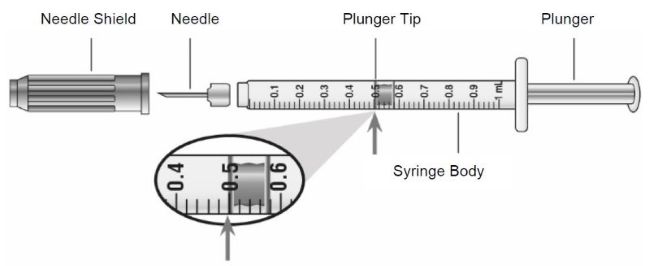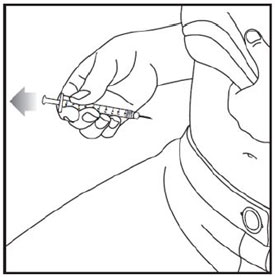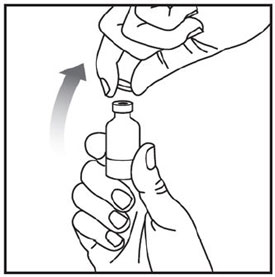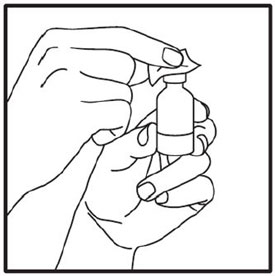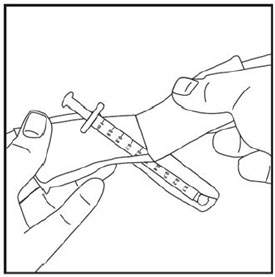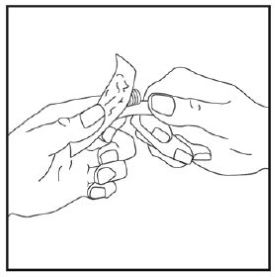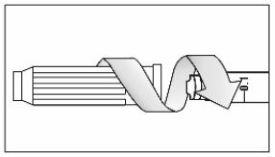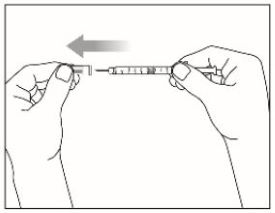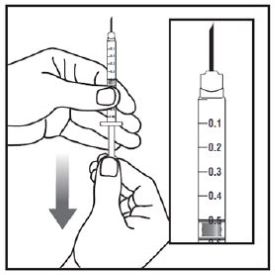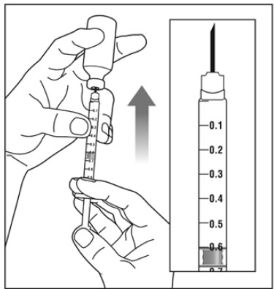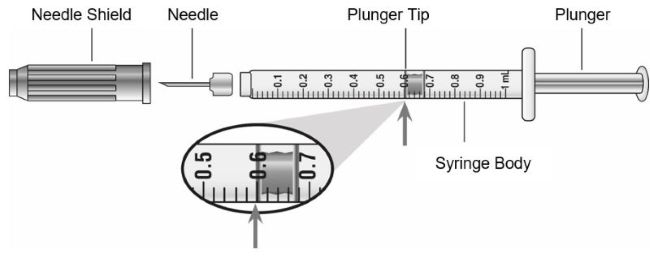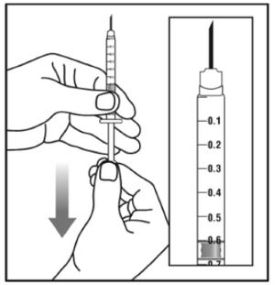 DRUG LABEL: ZEPBOUND
NDC: 0002-2506 | Form: INJECTION, SOLUTION
Manufacturer: Eli Lilly and Company
Category: prescription | Type: HUMAN PRESCRIPTION DRUG LABEL
Date: 20260225

ACTIVE INGREDIENTS: tirzepatide 2.5 mg/0.5 mL
INACTIVE INGREDIENTS: Sodium Phosphate, Dibasic, Heptahydrate 0.7 mg/0.5 mL; Sodium Chloride 4.1 mg/0.5 mL; Hydrochloric Acid; Sodium Hydroxide; Water

HIGHLIGHTS OF PRESCRIBING INFORMATION

These highlights do not include all the information needed to use ZEPBOUND safely and effectively. See full prescribing information for ZEPBOUND.
ZEPBOUND® (tirzepatide) Injection, for subcutaneous use
Initial U.S. Approval: 2022

RECENT MAJOR CHANGES

Dosage and Administration (2.4) | 01/2026
Warnings and Precautions
Severe Gastrointestinal Adverse Reactions (5.2) | 02/2026
Suicidal Behavior and Ideation (Removed) | 02/2026
Never Share a ZEPBOUND KwikPen Between Patients (5.10) | 01/2026

WARNING: RISK OF THYROID C-CELL TUMORS

See full prescribing information for complete boxed warning.

- In rats, tirzepatide causes thyroid C-cell tumors. It is unknown whether ZEPBOUND causes thyroid C-cell tumors, including medullary thyroid carcinoma (MTC), in humans as the human relevance of tirzepatide-induced rodent thyroid C-cell tumors has not been determined (5.1, 13.1).
- ZEPBOUND is contraindicated in patients with a personal or family history of MTC or in patients with Multiple Endocrine Neoplasia syndrome type 2 (MEN 2). Counsel patients regarding the potential risk of MTC and symptoms of thyroid tumors (4, 5.1).

1 INDICATIONS AND USAGE

ZEPBOUND is a glucose-dependent insulinotropic polypeptide (GIP) receptor and glucagon-like peptide-1 (GLP-1) receptor agonist indicated in combination with a reduced-calorie diet and increased physical activity:

- to reduce excess body weight and maintain weight reduction long term in adults with obesity or adults with overweight in the presence of at least one weight-related comorbid condition. (1)
- to treat moderate to severe obstructive sleep apnea (OSA) in adults with obesity. (1)

Limitations of Use:

Coadministration with other tirzepatide-containing products or with any GLP-1 receptor agonist is not recommended. (1)

2 DOSAGE AND ADMINISTRATION

Recommended Dose Escalation Schedule

- The recommended starting dosage is 2.5 mg injected subcutaneously once weekly for 4 weeks. Increase the dosage in 2.5 mg increments after at least 4 weeks until recommended maintenance dosage is achieved. (2.1)
- Consider treatment response and tolerability when selecting the maintenance dosage. (2.1)

Recommended Maintenance and Maximum Dosage

- Weight Reduction and Long-Term Maintenance: 5 mg, 10 mg, or 15 mg injected subcutaneously once weekly. (2.2)
- Obstructive Sleep Apnea: 10 mg or 15 mg injected subcutaneously once weekly. (2.2)

Maximum Recommended Dosage: 15 mg injected subcutaneously once weekly. (2.2)

Administration Instructions

Refer to the Full Prescribing Information for additional important administration instructions about ZEPBOUND presentations. (2.4)

3 DOSAGE FORMS AND STRENGTHS

Injection: 2.5 mg, 5 mg, 7.5 mg, 10 mg, 12.5 mg, or 15 mg per 0.5 mL in single-dose pen or single-dose vial (3)

Injection: 10 mg/2.4 mL (4.17 mg/mL) for four 2.5 mg/0.6 mL doses, 20 mg/2.4 mL (8.33 mg/mL) for four 5 mg/0.6 mL doses, 30 mg/2.4 mL (12.5 mg/mL) for four 7.5 mg/0.6 mL doses, 40 mg/2.4 mL (16.7 mg/mL) for four 10 mg/0.6 mL doses, 50 mg/2.4 mL (20.8 mg/mL) for four 12.5 mg/0.6 mL doses, or 60 mg/2.4 mL (25 mg/mL) for four 15 mg/0.6 mL doses in a multi-dose vial or single-patient-use KwikPen® (3)

4 CONTRAINDICATIONS

- Personal or family history of medullary thyroid carcinoma or in patients with Multiple Endocrine Neoplasia syndrome type 2 (4)
- Known serious hypersensitivity to tirzepatide or any of the excipients in ZEPBOUND (4)

5 WARNINGS AND PRECAUTIONS

- Severe Gastrointestinal Adverse Reactions: Use has been associated with gastrointestinal adverse reactions, sometimes severe. ZEPBOUND is not recommended in patients with severe gastroparesis. (5.2)
- Acute Kidney Injury Due to Volume Depletion: Monitor renal function in patients reporting adverse reactions that could lead to volume depletion. (5.3)
- Acute Gallbladder Disease: Has been reported in clinical trials. If cholecystitis is suspected, gallbladder studies and clinical follow-up are indicated. (5.4)
- Acute Pancreatitis: Has been observed in patients treated with GLP-1 receptor agonists, or ZEPBOUND. Discontinue if pancreatitis is suspected. (5.5)
- Hypersensitivity Reactions: Serious hypersensitivity reactions (e.g., anaphylaxis, angioedema) have been reported postmarketing with tirzepatide. If suspected, advise patients to promptly seek medical attention and discontinue ZEPBOUND. (5.6)
- Hypoglycemia: Concomitant use with insulin or an insulin secretagogue may increase the risk of hypoglycemia, including severe hypoglycemia. Reducing dose of insulin or insulin secretagogue may be necessary. Inform all patients of the risk of hypoglycemia and educate them on the signs and symptoms of hypoglycemia. (5.7)
- Diabetic Retinopathy Complications in Patients with Type 2 Diabetes Mellitus: Has not been studied in patients with non-proliferative diabetic retinopathy requiring acute therapy, proliferative diabetic retinopathy, or diabetic macular edema. Monitor patients with a history of diabetic retinopathy for progression. (5.8)
- Pulmonary Aspiration During General Anesthesia or Deep Sedation: Has been reported in patients receiving GLP-1 receptor agonists undergoing elective surgeries or procedures. Instruct patients to inform healthcare providers of any planned surgeries or procedures. (5.9)
- Never share a ZEPBOUND KwikPen between patients, even if the pen needle is changed. (5.10)

6 ADVERSE REACTIONS

The most common adverse reactions, reported in ≥5% of patients treated with ZEPBOUND are: nausea, diarrhea, vomiting, constipation, abdominal pain, dyspepsia, injection site reactions, fatigue, hypersensitivity reactions, eructation, hair loss, gastroesophageal reflux disease. (6.1)

To report SUSPECTED ADVERSE REACTIONS, contact Eli Lilly and Company at 1-800-LillyRx (1-800-545-5979) or FDA at 1-800-FDA-1088 or www.fda.gov/medwatch.

7 DRUG INTERACTIONS

ZEPBOUND delays gastric emptying and has the potential to impact the absorption of concomitantly administered oral medications. (7.2)

8 USE IN SPECIFIC POPULATIONS

- Pregnancy: May cause fetal harm. When pregnancy is recognized, discontinue ZEPBOUND. (8.1)
- Females of Reproductive Potential: Advise females using oral contraceptives to switch to a non-oral contraceptive method, or add a barrier method of contraception for 4 weeks after initiation and for 4 weeks after each dose escalation. (8.3)

FULL PRESCRIBING INFORMATION

WARNING: RISK OF THYROID C-CELL TUMORS

- In rats, tirzepatide causes dose-dependent and treatment-duration-dependent thyroid C-cell tumors at clinically relevant exposures. It is unknown whether ZEPBOUND causes thyroid C-cell tumors, including medullary thyroid carcinoma (MTC), in humans as human relevance of tirzepatide-induced rodent thyroid C-cell tumors has not been determined [see Warnings and Precautions (5.1) and Nonclinical Toxicology (13.1)].
- ZEPBOUND is contraindicated in patients with a personal or family history of MTC or in patients with Multiple Endocrine Neoplasia syndrome type 2 (MEN 2) [see Contraindications (4)]. Counsel patients regarding the potential risk for MTC with the use of ZEPBOUND and inform them of symptoms of thyroid tumors (e.g., a mass in the neck, dysphagia, dyspnea, persistent hoarseness). Routine monitoring of serum calcitonin or using thyroid ultrasound is of uncertain value for early detection of MTC in patients treated with ZEPBOUND [see Contraindications (4) and Warnings and Precautions (5.1)].

1 INDICATIONS AND USAGE

ZEPBOUND® is indicated in combination with a reduced-calorie diet and increased physical activity:

- to reduce excess body weight and maintain weight reduction long term in adults with obesity or adults with overweight in the presence of at least one weight-related comorbid condition.
- to treat moderate to severe obstructive sleep apnea (OSA) in adults with obesity.

Limitations of Use

ZEPBOUND contains tirzepatide. Coadministration with other tirzepatide-containing products or with any glucagon-like peptide-1 (GLP-1) receptor agonist is not recommended.

2 DOSAGE AND ADMINISTRATION

2.1 Recommended Dose Escalation Schedule

- The recommended starting dosage of ZEPBOUND for all indications is 2.5 mg injected subcutaneously once weekly for 4 weeks.
- The 2.5 mg dosage is for treatment initiation and is not approved as a maintenance dosage.
- Follow the dosage escalation below for all indications to reduce the risk of gastrointestinal adverse reactions [see Warnings and Precautions (5.2) and Adverse Reactions (6.1)].
- After 4 weeks, increase the dosage to 5 mg injected subcutaneously once weekly. The dosage may be increased in 2.5 mg increments, after at least 4 weeks on the current dose [see Dosage and Administration (2.2)].
- Consider treatment response and tolerability when selecting the maintenance dosage. If patients do not tolerate a maintenance dosage, consider a lower maintenance dosage.

2.2 Recommended Maintenance and Maximum Dosage

Recommended Maintenance Dosage

Weight Reduction and Long-Term Maintenance

The recommended maintenance dosage is 5 mg, 10 mg, or 15 mg, injected subcutaneously once weekly.

OSA

The recommended maintenance dosage is 10 mg or 15 mg injected subcutaneously once weekly.

Maximum Recommended Dosage

The maximum dosage of ZEPBOUND for all indications is 15 mg injected subcutaneously once weekly.

2.3 Recommendations Regarding Missed Dose

- If a dose is missed, instruct patients to administer ZEPBOUND as soon as possible within 4 days (96 hours) after the missed dose. If more than 4 days have passed, skip the missed dose and administer the next dose on the regularly scheduled day. In each case, patients can then resume their regular once weekly dosing schedule.
- The day of weekly administration can be changed, if necessary, as long as the time between the two doses is at least 3 days (72 hours).

2.4 Important Administration Instructions

- Inform patients and their caregiver(s) which ZEPBOUND presentation (e.g., vial, prefilled single-dose pen, single-patient-use KwikPen) they will receive and ensure they receive training appropriate for that specific presentation. If the prescribed ZEPBOUND presentation changes, ensure patients and caregivers receive appropriate training and instruct them to consult the Instructions for Use for the newly prescribed presentation.
- Prior to initiation, train patients and their caregiver(s) on proper injection technique for the prescribed ZEPBOUND presentation [see Instructions for Use]. After training, a patient may self-inject ZEPBOUND if the healthcare provider determines that it can be properly administered, except for the following:
  - ZEPBOUND KwikPen is not recommended for self-administration by those who are visually impaired.
- Instruct patients using ZEPBOUND vials to use a syringe appropriate for dose administration (e.g., a 1 mL syringe capable of measuring a 0.5 mL or 0.6 mL dose) and always use a new syringe and needle for each injection.
- Inspect ZEPBOUND visually before use. It should appear clear and colorless to slightly yellow. Do not use ZEPBOUND if particulate matter or discoloration is seen.
- Administer ZEPBOUND in combination with a reduced-calorie diet and increased physical activity.
- Administer ZEPBOUND once weekly at any time of day, with or without meals.
- Inject ZEPBOUND subcutaneously in the abdomen, thigh, or another person should inject in the back of the upper arm.
- Rotate injection sites with each dose.

3 DOSAGE FORMS AND STRENGTHS

Injection: Clear, colorless to slightly yellow solution in pre-filled single-dose pens, single-dose vials, multi-dose vials, or single-patient-use KwikPens, each available in the following strengths. The multi-dose vials and single-patient-use KwikPen each contain 4 doses:

Single-dose Pen or Vial

2.5 mg/0.5 mL

5 mg/0.5 mL

7.5 mg/0.5 mL

10 mg/0.5 mL

12.5 mg/0.5 mL

15 mg/0.5 mL

Multi-dose Vial (4 doses per vial)
Dose per Injection | Total Strength per Total Volume | Strength per mL
2.5 mg/0.6 mL | 10 mg/2.4 mL | 4.17 mg/mL
5 mg/0.6 mL | 20 mg/2.4 mL | 8.33 mg/mL
7.5 mg/0.6 mL | 30 mg/2.4 mL | 12.5 mg/mL
10 mg/0.6 mL | 40 mg/2.4 mL | 16.7 mg/mL
12.5 mg/0.6 mL | 50 mg/2.4 mL | 20.8 mg/mL
15 mg/0.6 mL | 60 mg/2.4 mL | 25 mg/mL

Single-Patient-Use KwikPen (4 doses per KwikPen)
Dose per Injection | Total Strength per Total Volume | Strength per mL
2.5 mg | 10 mg/2.4 mL | 4.17 mg/mL
5 mg | 20 mg/2.4 mL | 8.33 mg/mL
7.5 mg | 30 mg/2.4 mL | 12.5 mg/mL
10 mg | 40 mg/2.4 mL | 16.7 mg/mL
12.5 mg | 50 mg/2.4 mL | 20.8 mg/mL
15 mg | 60 mg/2.4 mL | 25 mg/mL

4 CONTRAINDICATIONS

ZEPBOUND is contraindicated in patients with:

- A personal or family history of MTC or in patients with MEN 2 [see Warnings and Precautions (5.1)].
- Known serious hypersensitivity to tirzepatide or any of the excipients in ZEPBOUND. Serious hypersensitivity reactions, including anaphylaxis and angioedema, have been reported with tirzepatide [see Warnings and Precautions (5.6) and Adverse Reactions (6.2)].

5 WARNINGS AND PRECAUTIONS

5.1 Risk of Thyroid C-Cell Tumors

In rats, tirzepatide caused a dose-dependent and treatment-duration-dependent increase in the incidence of thyroid C-cell tumors (adenomas and carcinomas) in a 2-year study at clinically relevant plasma exposures [see Nonclinical Toxicology (13.1)]. It is unknown whether ZEPBOUND causes thyroid C-cell tumors, including MTC, in humans as human relevance of tirzepatide-induced rodent thyroid C-cell tumors has not been determined.

ZEPBOUND is contraindicated in patients with a personal or family history of MTC or in patients with MEN 2. Counsel patients regarding the potential risk for MTC with the use of ZEPBOUND and inform them of symptoms of thyroid tumors (e.g., a mass in the neck, dysphagia, dyspnea, persistent hoarseness).

Routine monitoring of serum calcitonin or using thyroid ultrasound is of uncertain value for early detection of MTC in patients treated with ZEPBOUND. Such monitoring may increase the risk of unnecessary procedures, due to the low test specificity for serum calcitonin and a high background incidence of thyroid disease. Significantly elevated serum calcitonin values may indicate MTC and patients with MTC usually have calcitonin values >50 ng/L. If serum calcitonin is measured and found to be elevated, the patient should be further evaluated. Patients with thyroid nodules noted on physical examination or neck imaging should also be further evaluated.

5.2 Severe Gastrointestinal Adverse Reactions

Use of ZEPBOUND has been associated with gastrointestinal adverse reactions, sometimes severe [see Adverse Reactions (6)]. In a pool of two ZEPBOUND clinical trials for weight reduction (Studies 1 and 2), severe gastrointestinal adverse reactions were reported more frequently among patients receiving ZEPBOUND (5 mg 1.7%, 10 mg 2.5%, 15 mg 3.1%) than placebo (1%). Similar rates of severe gastrointestinal adverse reactions were observed in ZEPBOUND clinical trials for weight reduction and in ZEPBOUND clinical trials for OSA. Severe gastrointestinal adverse reactions have also been reported postmarketing with GLP-1 receptor agonists.

ZEPBOUND is not recommended in patients with severe gastroparesis.

5.3 Acute Kidney Injury Due to Volume Depletion

There have been postmarketing reports of acute kidney injury, in some cases requiring hemodialysis, in patients treated with GLP-1 receptor agonists, or ZEPBOUND [see Adverse Reactions (6.2)]. The majority of the reported events occurred in patients who experienced gastrointestinal adverse reactions leading to dehydration such as nausea, vomiting, or diarrhea [see Adverse Reactions (6.1)]. Monitor renal function in patients reporting adverse reactions to ZEPBOUND that could lead to volume depletion, especially during dosage initiation and escalation of ZEPBOUND.

5.4 Acute Gallbladder Disease

Treatment with ZEPBOUND and GLP-1 receptor agonists is associated with an increased occurrence of acute gallbladder disease.

In a pool of two ZEPBOUND clinical trials for weight reduction (Studies 1 and 2), cholelithiasis was reported in 1.1% of ZEPBOUND-treated patients and 1% of placebo-treated patients, cholecystitis was reported in 0.7% of ZEPBOUND-treated patients and 0.2% of placebo-treated patients, and cholecystectomy was reported in 0.2% of ZEPBOUND-treated patients and no placebo-treated patients. Acute gallbladder events were associated with weight reduction. Similar rates of cholelithiasis were reported in ZEPBOUND clinical trials for weight reduction and in ZEPBOUND trials for OSA. If cholecystitis is suspected, gallbladder diagnostic studies and appropriate clinical follow-up are indicated.

5.5 Acute Pancreatitis

Acute pancreatitis, including fatal and non-fatal hemorrhagic or necrotizing pancreatitis, has been observed in patients treated with GLP-1 receptor agonists, or ZEPBOUND [see Adverse Reactions (6)].

After initiation of ZEPBOUND, observe patients carefully for signs and symptoms of acute pancreatitis which may include persistent or severe abdominal pain (sometimes radiating to the back) and which may or may not be accompanied by nausea or vomiting. If pancreatitis is suspected, discontinue ZEPBOUND and initiate appropriate management.

5.6 Hypersensitivity Reactions

There have been postmarketing reports of serious hypersensitivity reactions (e.g., anaphylaxis, angioedema) in patients treated with tirzepatide. In a pool of two ZEPBOUND clinical studies for weight reduction (Studies 1 and 2), 0.1% of ZEPBOUND-treated patients had severe hypersensitivity reactions compared to no placebo-treated patients. Similar rates of severe hypersensitivity reactions were observed in ZEPBOUND clinical trials for weight reduction and in ZEPBOUND trials for OSA. If hypersensitivity reactions occur, advise patients to promptly seek medical attention and discontinue use of ZEPBOUND. Do not use in patients with a previous serious hypersensitivity reaction to tirzepatide or any of the excipients in ZEPBOUND [see Contraindications (4) and Adverse Reactions (6.2)].

Serious hypersensitivity reactions, including anaphylaxis and angioedema, have been reported with GLP-1 receptor agonists. Use caution in patients with a history of angioedema or anaphylaxis with a GLP-1 receptor agonist because it is unknown whether such patients will be predisposed to these reactions with ZEPBOUND.

5.7 Hypoglycemia

ZEPBOUND lowers blood glucose and can cause hypoglycemia.

In a trial of patients with type 2 diabetes mellitus and BMI ≥27 kg/m^2 (Study 2), hypoglycemia (plasma glucose <54 mg/dL) was reported in 4.2% of ZEPBOUND-treated patients versus 1.3% of placebo-treated patients. In this trial, patients taking ZEPBOUND in combination with an insulin secretagogue (e.g., sulfonylurea) had increased risk of hypoglycemia (10.3%) compared to ZEPBOUND-treated patients not taking a sulfonylurea (2.1%). There is also increased risk of hypoglycemia in patients treated with tirzepatide in combination with insulin [see Drug Interactions (7.1)].

Hypoglycemia has also been associated with ZEPBOUND and GLP-1 receptor agonists in adults without type 2 diabetes mellitus [see Adverse Reactions (6.1)].

Inform patients of the risk of hypoglycemia and educate them on the signs and symptoms of hypoglycemia. In patients with diabetes mellitus, monitor blood glucose prior to starting ZEPBOUND and during ZEPBOUND treatment. The risk of hypoglycemia may be lowered by a reduction in the dose of insulin or sulfonylurea (or other concomitantly administered insulin secretagogue).

5.8 Diabetic Retinopathy Complications in Patients with Type 2 Diabetes Mellitus

Rapid improvement in glucose control has been associated with a temporary worsening of diabetic retinopathy. Tirzepatide has not been studied in patients with non-proliferative diabetic retinopathy requiring acute therapy, proliferative diabetic retinopathy, or diabetic macular edema. Patients with a history of diabetic retinopathy should be monitored for progression of diabetic retinopathy.

5.9 Pulmonary Aspiration During General Anesthesia or Deep Sedation

ZEPBOUND delays gastric emptying [see Clinical Pharmacology (12.2)]. There have been rare postmarketing reports of pulmonary aspiration in patients receiving GLP-1 receptor agonists undergoing elective surgeries or procedures requiring general anesthesia or deep sedation who had residual gastric contents despite reported adherence to preoperative fasting recommendations.

Available data are insufficient to inform recommendations to mitigate the risk of pulmonary aspiration during general anesthesia or deep sedation in patients taking ZEPBOUND, including whether modifying preoperative fasting recommendations or temporarily discontinuing ZEPBOUND could reduce the incidence of retained gastric contents. Instruct patients to inform healthcare providers prior to any planned surgeries or procedures if they are taking ZEPBOUND.

5.10 Never Share a ZEPBOUND KwikPen Between Patients

Never share ZEPBOUND KwikPen between patients, even if the pen needle is changed. Sharing poses a risk for transmission of blood-borne pathogens.

6 ADVERSE REACTIONS

The following serious adverse reactions are described below or elsewhere in the prescribing information:

- Risk of Thyroid C-cell Tumors [see Warnings and Precautions (5.1)]
- Severe Gastrointestinal Adverse Reactions [see Warnings and Precautions (5.2)]
- Acute Kidney Injury Due to Volume Depletion [see Warnings and Precautions (5.3)]
- Acute Gallbladder Disease [see Warnings and Precautions (5.4)]
- Acute Pancreatitis [see Warnings and Precautions (5.5)]
- Hypersensitivity Reactions [see Warnings and Precautions (5.6)]
- Hypoglycemia [see Warnings and Precautions (5.7)]
- Diabetic Retinopathy Complications in Patients with Type 2 Diabetes Mellitus [see Warnings and Precautions (5.8)]
- Pulmonary Aspiration During General Anesthesia or Deep Sedation [see Warnings and Precautions (5.9)]

6.1 Clinical Trials Experience

Because clinical trials are conducted under widely varying conditions, adverse reaction rates observed in the clinical trials of a drug cannot be directly compared to rates in the clinical trials of another drug and may not reflect the rates observed in practice.

Adverse Reactions in Patients for Weight Reduction and Long-Term Maintenance

Pool of Placebo-Controlled Weight Reduction Trials in Adults with Obesity or Overweight, with or without Type 2 Diabetes (Study 1 and Study 2)

ZEPBOUND was evaluated for safety in a pool of two randomized, double-blind, placebo-controlled trials that included 2,519 adult patients with obesity or overweight treated with ZEPBOUND for up to 72 weeks and a 4-week off drug follow-up period (Study 1 and Study 2) [see Clinical Studies (14.1)]. The mean age of patients was 47 years and 37% were male. The population was 72% White, 12% Asian, 8% Black or African American, and 7% American Indian or Alaska Native; 51% identified as Hispanic or Latino ethnicity. Baseline characteristics included an average BMI of 37.4 kg/m^2, 29% with a BMI ≥40 kg/m^2, 41% with hypertension, 37% with dyslipidemia, 25% with type 2 diabetes mellitus, 7% with obstructive sleep apnea, and 4% with cardiovascular disease.

Across both trials, 4.8%, 6.3%, and 6.7% of patients treated with 5 mg, 10 mg, and 15 mg of ZEPBOUND, respectively, permanently discontinued treatment as a result of adverse reactions compared to 3.4% of patients treated with placebo. The majority of patients who discontinued ZEPBOUND due to adverse reactions did so during the first few months of treatment due to gastrointestinal adverse reactions.

Common Adverse Reactions

Table 1 shows common adverse reactions associated with the use of ZEPBOUND in the pool of two placebo-controlled trials for weight reduction (Study 1 and Study 2). These adverse reactions occurred more commonly with ZEPBOUND than with placebo and occurred in at least 2% of patients treated with ZEPBOUND.

Table 1: Adverse Reactions (≥2% and Greater than Placebo) in ZEPBOUND-Treated Adults with Obesity or Overweight in Weight Reduction and Long-term Maintenance Trials (Study 1 and Study 2)
Adverse Reaction | Placebo (N=958) % | ZEPBOUND 5 mg (N=630) % | ZEPBOUND 10 mg (N=948) % | ZEPBOUND 15 mg (N=941) %
Nausea | 8 | 25 | 29 | 28
Diarrheaa | 8 | 19 | 21 | 23
Vomiting | 2 | 8 | 11 | 13
Constipationb | 5 | 17 | 14 | 11
Abdominal Painc | 5 | 9 | 9 | 10
Dyspepsia | 4 | 9 | 9 | 10
Injection Site Reactionsd | 2 | 6 | 8 | 8
Fatiguee | 3 | 5 | 6 | 7
Hypersensitivity Reactions | 3 | 5 | 5 | 5
Eructation | 1 | 4 | 5 | 5
Hair Loss | 1 | 5 | 4 | 5
Gastroesophageal Reflux Disease | 2 | 4 | 4 | 5
Flatulence | 2 | 3 | 3 | 4
Abdominal Distension | 2 | 3 | 3 | 4
Dizziness | 2 | 4 | 5 | 4
Hypotensionf | 0 | 1 | 1 | 2
a Includes diarrhea, frequent bowel movements.
b Includes constipation, feces hard.
c Includes abdominal discomfort, abdominal pain, abdominal pain lower, abdominal pain upper, abdominal tenderness.
d Includes multiple related adverse event terms, such as injection site bruising, injection site erythema, injection site pruritus, injection site pain, injection site rash, injection site reaction.
e Includes asthenia, fatigue, lethargy, malaise.
f Includes blood pressure decreased, hypotension, orthostatic hypotension.

In a clinical trial for weight reduction that included an intensive lifestyle intervention lead-in period (Study 3), 287 patients were treated with ZEPBOUND for up to 72 weeks. In a randomized withdrawal trial (Study 4), 783 patients were treated with ZEPBOUND for up to 36 weeks, and 335 of these patients were treated for up to 88 weeks [see Clinical Studies (14.1)]. In Study 3, 10% of ZEPBOUND-treated patients and 2% of placebo-treated patients discontinued drug due to adverse reactions. In Study 4, 7% of patients discontinued ZEPBOUND treatment before randomized withdrawal at Week 36 due to adverse reactions. In Study 3 and Study 4, adverse reactions were similar to those reported in the two pooled ZEPBOUND clinical trials (Study 1 and Study 2).

Gastrointestinal Adverse Reactions

In a pool of Study 1 and 2, gastrointestinal adverse reactions occurred more frequently among patients receiving ZEPBOUND (5 mg 56%, 10 mg 56%, 15 mg 56%) than placebo (30%). More patients receiving ZEPBOUND 5 mg (1.9%), ZEPBOUND 10 mg (3.3%), and ZEPBOUND 15 mg (4.3%) discontinued treatment due to gastrointestinal adverse reactions than patients receiving placebo (0.5%). The majority of nausea, vomiting, and/or diarrhea events occurred during dose escalation and decreased over time.

Acute Pancreatitis

In clinical trials of tirzepatide for a different indication, 14 events of acute pancreatitis were confirmed by adjudication in 13 tirzepatide-treated patients (0.23 patients per 100 years of exposure) versus 3 events in 3 comparator-treated patients (0.11 patients per 100 years of exposure). In a pool of two ZEPBOUND clinical trials for weight reduction (Studies 1 and 2), 0.2% of ZEPBOUND-treated patients had acute pancreatitis confirmed by adjudication (0.14 patients per 100 years of exposure) versus 0.2% of placebo-treated patients (0.15 patients per 100 years of exposure). The exposure-adjusted incidence rate for treatment-emergent adjudication-confirmed pancreatitis in the pooled clinical studies for OSA (Studies 5 and 6) was 0.84 patients per 100 years for ZEPBOUND and 0 for placebo-treated patients.

Hypotension

In a pool of Study 1 and 2, hypotension occurred more frequently among patients taking ZEPBOUND (1.6%) than patients taking placebo (0.1%). Hypotension was more frequently seen in ZEPBOUND-treated patients on concomitant antihypertensive therapy (2.2%) compared to ZEPBOUND-treated patients not on antihypertensive therapy (1.2%). Hypotension also occurred in association with gastrointestinal adverse events and dehydration.

Hypersensitivity Reactions

In a pool of Study 1 and 2, immediate hypersensitivity reactions (within one day after drug administration) occurred in 2.1% of ZEPBOUND-treated patients compared to 0.4% of placebo-treated patients, while non-immediate hypersensitivity reactions occurred in 3.5% of ZEPBOUND-treated patients compared to 2.7% of placebo-treated patients. Among ZEPBOUND-treated patients, hypersensitivity reactions were more frequent in those with anti-tirzepatide antibodies (6.2%) compared to those who did not develop anti-tirzepatide antibodies (3%) [see Clinical Pharmacology (12.6)]. The majority of the hypersensitivity reactions in trials were skin reactions (e.g., rash, itching).

Injection Site Reactions

In ZEPBOUND-treated patients in a pool of Study 1 and 2, injection site reactions were more frequent in those with anti-tirzepatide antibodies (11.3%) compared to those who did not develop anti-tirzepatide antibodies (1%) [see Clinical Pharmacology (12.6)].

Hair Loss

Hair loss adverse reactions in ZEPBOUND-treated patients were associated with weight reduction. In a pool of Study 1 and 2, hair loss was reported more frequently in female than male patients in the ZEPBOUND (7.1% female versus 0.5% male) and placebo (1.3% female versus 0% male) treatment groups. No ZEPBOUND-treated patients and one placebo-treated patient discontinued study treatment due to hair loss.

Other Adverse Reactions

Acute Kidney Injury

In a pool of Study 1 and 2, acute kidney injury was reported in 0.5% of ZEPBOUND-treated patients compared to 0.2% of placebo-treated patients.

Acute Gallbladder Disease

In a pool of Study 1 and 2, cholelithiasis was reported in 1.1% of ZEPBOUND-treated patients and 1% of placebo-treated patients, cholecystitis was reported in 0.7% of ZEPBOUND-treated patients and 0.2% of placebo-treated patients, and cholecystectomy was reported in 0.2% of ZEPBOUND-treated patients and no placebo-treated patients.

Hypoglycemia

In Study 2, a trial of patients with type 2 diabetes mellitus and BMI ≥27 kg/m^2, hypoglycemia (plasma glucose <54 mg/dL) was reported in 4.2% of ZEPBOUND-treated patients versus 1.3% of placebo-treated patients.

In Study 1, a trial of ZEPBOUND in adults with obesity/overweight without type 2 diabetes mellitus, there was no systematic capturing of hypoglycemia, but plasma glucose <54 mg/dL was reported in 0.3% of ZEPBOUND-treated patients versus no placebo-treated patients.

Heart Rate Increase

In a pool of Study 1 and 2, treatment with ZEPBOUND resulted in a mean increase in heart rate of 1 to 3 beats per minute compared to no increase in placebo-treated patients.

Dysesthesia

In a pool of Study 1 and 2, dysesthesia occurred more frequently among patients receiving ZEPBOUND (5 mg 0.2%, 10 mg 0.2%, 15 mg 0.4%) than placebo (0.1%).

Dysgeusia

In a pool of Study 1 and 2, dysgeusia was reported by 0.4% of ZEPBOUND-treated patients and no placebo-treated patients.

Dry Mouth

In a pool of Study 1 and 2, dry mouth or dry throat was reported by 1% of ZEPBOUND-treated patients and 0.1% of placebo-treated patients.

Laboratory Abnormalities

Amylase and Lipase Increase

In a pool of Study 1 and 2, treatment with ZEPBOUND resulted in mean increases from baseline in serum pancreatic amylase concentrations of 20% to 25% and serum lipase concentrations of 28% to 35%, compared to mean increases from baseline in pancreatic amylase of 2.1% and serum lipase of 5.8% in placebo-treated patients. The clinical significance of elevations in amylase or lipase with ZEPBOUND is unknown in the absence of other signs and symptoms of pancreatitis.

Adverse Reactions in Patients with Obstructive Sleep Apnea

ZEPBOUND was evaluated in 2 randomized, double-blind, placebo-controlled trials (Study 5 and Study 6) that included a total of 467 adult patients with moderate to severe OSA and obesity [see Clinical Studies (14.2)]. Study 5 enrolled 234 patients who were unable or unwilling to use Positive Airway Pressure (PAP) therapy and Study 6 enrolled 235 patients who were on PAP therapy. The adverse reactions observed with ZEPBOUND 10 mg or 15 mg administered subcutaneously once weekly were similar to those reported in the two pooled placebo controlled clinical trials for weight reduction (Study 1 and Study 2).

6.2 Postmarketing Experience

The following adverse reactions have been reported during post-approval use of tirzepatide, the active ingredient in ZEPBOUND. Because these reactions are reported voluntarily from a population of uncertain size, it is not always possible to reliably estimate their frequency or to establish a causal relationship to drug exposure.

Gastrointestinal: acute pancreatitis, hemorrhagic and necrotizing pancreatitis sometimes resulting in death, ileus, intestinal obstruction, severe constipation including fecal impaction

Hypersensitivity: anaphylaxis, angioedema

Pulmonary: Pulmonary aspiration has occurred in patients receiving GLP-1 receptor agonists undergoing elective surgeries or procedures requiring general anesthesia or deep sedation.

Renal: acute renal failure or worsening of chronic renal failure, sometimes requiring hemodialysis

7 DRUG INTERACTIONS

7.1 Concomitant Use with Insulin or an Insulin Secretagogue (e.g., Sulfonylurea)

ZEPBOUND lowers blood glucose. When initiating ZEPBOUND, consider reducing the dose of concomitantly administered insulin or insulin secretagogues (e.g., sulfonylureas) to reduce the risk of hypoglycemia [see Warnings and Precautions (5.7)].

7.2 Oral Medications

ZEPBOUND delays gastric emptying and thereby has the potential to impact the absorption of concomitantly administered oral medications. Caution should be exercised when oral medications are concomitantly administered with ZEPBOUND.

Monitor patients on oral medications dependent on threshold concentrations for efficacy and those with a narrow therapeutic index (e.g., warfarin) when concomitantly administered with ZEPBOUND.

Advise patients using oral hormonal contraceptives to switch to a non-oral contraceptive method, or add a barrier method of contraception for 4 weeks after initiation with ZEPBOUND and for 4 weeks after each dose escalation. Hormonal contraceptives that are not administered orally should not be affected [see Use in Specific Populations (8.3) and Clinical Pharmacology (12.2, 12.3)].

8 USE IN SPECIFIC POPULATIONS

8.1 Pregnancy

Pregnancy Exposure Registry

There will be a pregnancy exposure registry that monitors pregnancy outcomes in women exposed to ZEPBOUND (tirzepatide) during pregnancy. Pregnant patients exposed to ZEPBOUND and healthcare providers are encouraged to contact Eli Lilly and Company at 1-800-LillyRx (1-800-545-5979).

Risk Summary

Weight loss offers no benefit to a pregnant patient and may cause fetal harm. Advise pregnant patients that weight loss is not recommended during pregnancy and to discontinue ZEPBOUND when a pregnancy is recognized (see Clinical Considerations). Available data with tirzepatide in pregnant patients are insufficient to evaluate for a drug-related risk of major birth defects, miscarriage, or other adverse maternal or fetal outcomes. Based on animal reproduction studies, there may be risks to the fetus from exposure to tirzepatide during pregnancy.

In pregnant rats administered tirzepatide during organogenesis, fetal growth reductions and fetal abnormalities occurred at clinical exposure in maternal rats based on AUC. In rabbits administered tirzepatide during organogenesis, fetal growth reductions were observed at clinically relevant exposures based on AUC. These adverse embryo/fetal effects in animals coincided with pharmacological effects on maternal weight and food consumption (see Data).

The estimated background risk of major birth defects and miscarriage for the indicated population is increased when compared to the general population. In the U.S. general population, the estimated background risk of major birth defects and miscarriage in clinically recognized pregnancies is 2-4% and 15-20%, respectively.

Clinical Considerations

Disease-Associated Maternal and/or Embryo/Fetal Risk

Appropriate weight gain based on pre-pregnancy weight is currently recommended for all pregnant patients, including those with obesity or overweight, due to the obligatory weight gain that occurs in maternal tissues during pregnancy.

Data

Animal Data

In pregnant rats given twice weekly subcutaneous doses of 0.02, 0.1, and 0.5 mg/kg tirzepatide [0.03-, 0.07-, and 0.5-fold the maximum recommended human dose (MRHD) of 15 mg once weekly based on AUC] during organogenesis, increased incidences of external, visceral, and skeletal malformations, increased incidences of visceral and skeletal developmental variations, and decreased fetal weights coincided with pharmacologically-mediated reductions in maternal body weights and food consumption at 0.5 mg/kg. In pregnant rabbits given once weekly subcutaneous doses of 0.01, 0.03, or 0.1 mg/kg tirzepatide (0.01-, 0.06-, and 0.2-fold the MRHD) during organogenesis, pharmacologically mediated effects on the gastrointestinal system resulting in maternal mortality or abortion in a few rabbits occurred at all dose levels. Reduced fetal weights associated with decreased maternal food consumption and body weights were observed at 0.1 mg/kg. In a pre- and post-natal study in rats administered subcutaneous doses of 0.02, 0.10, or 0.25 mg/kg tirzepatide twice weekly from implantation through lactation, F1 pups from F0 maternal rats given 0.25 mg/kg tirzepatide had statistically significant lower mean body weight when compared to controls from post-natal day 7 through post-natal day 126 for males and post-natal day 56 for females.

8.2 Lactation

Risk Summary

In a single-dose clinical lactation study, the concentration of tirzepatide in breast milk was found to be either undetectable or low compared to the maternal administered dose (see Data). There are no available data on the effects of tirzepatide on the breastfed infant or on milk production. The developmental and health benefits of breastfeeding should be considered along with the mother's clinical need for ZEPBOUND and any potential adverse effects on the breastfed infant from ZEPBOUND or from the underlying maternal condition.

Data

Following subcutaneous administration of a single 5 mg dose to 11 healthy lactating adult females, the concentration of tirzepatide in breast milk was found to be undetectable (limit of detection in breast milk 4 ng/mL) in 164/171 samples assayed. The cumulative amount of tirzepatide detected in the remaining 7 breast milk samples over the 28-day sampling window was equivalent to less than 0.02% of the maternal administered dose, with the last measurable concentrations occurring 5 days post-dose. The AUC of tirzepatide in breast milk could not be calculated, due to insufficient quantifiable concentrations.

8.3 Females and Males of Reproductive Potential

Contraception

Use of ZEPBOUND may reduce the efficacy of oral hormonal contraceptives due to delayed gastric emptying. This delay is largest after the first dose and diminishes over time. Advise patients using oral hormonal contraceptives to switch to a non-oral contraceptive method, or add a barrier method of contraception for 4 weeks after initiation with ZEPBOUND and for 4 weeks after each dose escalation [see Drug Interactions (7.2) and Clinical Pharmacology (12.2, 12.3)].

8.4 Pediatric Use

The safety and effectiveness of ZEPBOUND have not been established in pediatric patients.

8.5 Geriatric Use

In a pool of two fixed dose ZEPBOUND clinical studies for weight reduction (Study 1 and Study 2), 226 (9%) ZEPBOUND-treated patients were 65 years of age or older, and 13 (0.5%) ZEPBOUND-treated patients were 75 years of age or older at baseline.

No overall differences in safety or effectiveness of ZEPBOUND have been observed between patients 65 years of age and older and younger adult patients.

ZEPBOUND clinical studies in OSA (Study 5 and Study 6) did not include sufficient numbers of patients age 65 years or older to determine whether they respond differently from younger adult patients. Other reported clinical experience with tirzepatide has not identified differences in responses between the elderly and younger patients.

8.6 Renal Impairment

No dosage adjustment of ZEPBOUND is recommended for patients with renal impairment. In subjects with renal impairment including end-stage renal disease (ESRD), no change in tirzepatide pharmacokinetics (PK) was observed [see Clinical Pharmacology (12.3)]. Monitor renal function in patients reporting adverse reactions to ZEPBOUND that could lead to volume depletion [see Warnings and Precautions (5.3)].

8.7 Hepatic Impairment

No dosage adjustment of ZEPBOUND is recommended for patients with hepatic impairment. In a clinical pharmacology study in subjects with varying degrees of hepatic impairment, no change in tirzepatide PK was observed [see Clinical Pharmacology (12.3)].

10 OVERDOSAGE

In the event of an overdosage, contact the Poison Help Line (1-800-222-1222) or a medical toxicologist for additional overdosage management recommendations. Appropriate supportive treatment should be initiated according to the patient's clinical signs and symptoms. A period of observation and treatment for these symptoms may be necessary, taking into account the half-life of tirzepatide of approximately 5 days.

11 DESCRIPTION

ZEPBOUND (tirzepatide) injection, for subcutaneous use, contains tirzepatide, a GIP receptor and GLP-1 receptor agonist. Tirzepatide is based on the GIP sequence and contains aminoisobutyric acid (Aib) in positions 2 and 13, a C-terminal amide, and Lys residue at position 20 that is attached to 1,20-eicosanedioic acid via a linker. The molecular weight is 4813.53 Da and the empirical formula is C225H348N48O68.

Structural formula:

ZEPBOUND is a clear, colorless to slightly yellow, sterile solution for subcutaneous use. Each single-dose pen or single-dose vial contains a 0.5 mL solution of 2.5 mg, 5 mg, 7.5 mg, 10 mg, 12.5 mg, or 15 mg of tirzepatide and the following excipients: sodium chloride (4.1 mg), sodium phosphate dibasic heptahydrate (0.7 mg), and water for injection. Each multi-dose vial or single-patient-use KwikPen contains 2.4 mL of solution, which provides 4 doses of 2.5 mg, 5 mg, 7.5 mg, 10 mg, 12.5 mg, or 15 mg of tirzepatide per 0.6 mL. Each dose contains the following excipients: benzyl alcohol (5.4 mg), glycerin (4.8 mg), phenol (1.08 mg), sodium chloride (1.05 mg), sodium phosphate dibasic heptahydrate (0.8 mg), and water for injection. Hydrochloric acid solution and/or sodium hydroxide solution may have been added to adjust the pH. ZEPBOUND has a pH of 6.5 to 7.5.

Each single-patient-use KwikPen contains additional volume to allow for device priming.

12 CLINICAL PHARMACOLOGY

12.1 Mechanism of Action

Tirzepatide is a GIP receptor and GLP-1 receptor agonist. It contains a C20 fatty diacid that enables albumin binding and prolongs the half-life. Tirzepatide selectively binds to and activates both the GIP and GLP-1 receptors, the targets for native GIP and GLP-1.

GLP-1 is a physiological regulator of appetite and caloric intake. Nonclinical studies suggest the addition of GIP may further contribute to the regulation of food intake.

Both GIP receptors and GLP-1 receptors are found in areas of the brain involved in appetite regulation. Animal studies show that tirzepatide distributes to and activates neurons in brain regions involved in regulation of appetite and food intake.

12.2 Pharmacodynamics

Tirzepatide lowers body weight with greater fat mass loss than lean mass loss.

Tirzepatide decreases calorie intake. The effects are likely mediated by affecting appetite.

Tirzepatide stimulates insulin secretion in a glucose-dependent manner and reduces glucagon secretion. Tirzepatide increases insulin sensitivity, as demonstrated in a hyperinsulinemic euglycemic clamp study in patients with type 2 diabetes mellitus after 28 weeks of treatment. These effects can lead to a reduction of blood glucose.

Tirzepatide delays gastric emptying. The delay is largest after the first dose and this effect diminishes over time.

12.3 Pharmacokinetics

The pharmacokinetics of tirzepatide is similar between healthy subjects, patients with overweight or obesity, and patients with OSA and obesity. Steady-state plasma tirzepatide concentrations were achieved following 4 weeks of once weekly administration. Tirzepatide exposure increases in a dose-proportional manner.

Absorption

Following subcutaneous administration, the median time (range) to maximum plasma concentration of tirzepatide is 24 hours (8 to 72 hours). The mean absolute bioavailability of tirzepatide following subcutaneous administration is 80%. Similar exposure was achieved with subcutaneous administration of tirzepatide in the abdomen, thigh, or upper arm.

Distribution

The mean [coefficient of variation (CV)%] apparent steady-state volumes of distribution of tirzepatide following subcutaneous administration in patients with overweight or obesity and patients with OSA and obesity are approximately 9.7 L (29%) and 11.8 L (37%), respectively. Tirzepatide is highly bound to plasma albumin (99%).

Elimination

The apparent population mean clearance of tirzepatide in patients with overweight or obesity and patients with OSA and obesity is approximately 0.06 L/h (CV% ~ 20%). The elimination half-life is approximately 5-6 days in patients with overweight or obesity, and in patients with OSA and obesity.

Metabolism

Tirzepatide is metabolized by proteolytic cleavage of the peptide backbone, beta-oxidation of the C20 fatty diacid, and amide hydrolysis.

Excretion

The primary excretion routes of tirzepatide metabolites are via urine and feces. Intact tirzepatide is not observed in urine or feces.

Specific Populations

The intrinsic factors of age (18 to 84 years), sex, race (71% White, 11% Asian, 9% American Indian or Alaska Native, and 8% Black or African American), ethnicity, or body weight do not have a clinically relevant effect on the PK of tirzepatide.

Patients with Renal Impairment

Renal impairment does not impact the pharmacokinetics of tirzepatide. The pharmacokinetics of tirzepatide after a single 5 mg dose were evaluated in patients with different degrees of renal impairment (mild, moderate, severe, ESRD) compared with subjects with normal renal function. Data from clinical studies have also shown that renal impairment in patients with overweight or obesity does not impact the pharmacokinetics of tirzepatide [see Use in Specific Populations (8.6)].

Patients with Hepatic Impairment

Hepatic impairment does not impact the pharmacokinetics of tirzepatide. The pharmacokinetics of tirzepatide after a single 5 mg dose were evaluated in patients with different degrees of hepatic impairment (mild, moderate, severe) compared with subjects with normal hepatic function [see Use in Specific Populations (8.7)].

Drug Interaction Studies

Potential for Tirzepatide to Influence the Pharmacokinetics of Other Drugs

In vitro studies have shown low potential for tirzepatide to inhibit or induce CYP enzymes, and to inhibit drug transporters.

ZEPBOUND delays gastric emptying and thereby has the potential to impact the absorption of concomitantly administered oral medications [see Drug Interactions (7.2)].

The impact of tirzepatide on gastric emptying was greatest after a single dose of 5 mg and diminished after subsequent doses.

Following a first dose of tirzepatide 5 mg, acetaminophen maximum concentration (Cmax) was reduced by 55%, and the median peak plasma concentration (tmax) occurred 1 hour later. After coadministration at Week 6 with tirzepatide 15 mg, there was no meaningful impact on acetaminophen Cmax and tmax. Overall acetaminophen exposure (AUC0-24hr) was not influenced.

Following administration of a combined oral contraceptive (0.035 mg ethinyl estradiol and 0.25 mg norgestimate) in the presence of a single dose of tirzepatide 5 mg, mean Cmax of ethinyl estradiol, norgestimate, and norelgestromin was reduced by 59%, 66%, and 55%, while mean AUC was reduced by 20%, 21%, and 23%, respectively. A delay in tmax of 2.5 to 4.5 hours was observed.

12.6 Immunogenicity

The observed incidence of anti-drug antibodies is highly dependent on the sensitivity and specificity of the assay. Differences in assay methods preclude meaningful comparisons of the incidence of anti-drug antibodies in the studies described below with the incidence of anti-drug antibodies in other studies.

The incidence of anti-drug antibodies (ADA) to ZEPBOUND was evaluated in adult patients with overweight or obesity or with OSA and obesity in clinical studies lasting 52 weeks or longer. Anti-tirzepatide antibodies were detected in 64.5% (1591/2467) of ZEPBOUND-treated patients in weight reduction clinical studies 1 and 2, and 60.6% (137/226) of ZEPBOUND-treated patients in OSA clinical studies [see Clinical Studies (14)].

Of the ZEPBOUND-treated patients in weight reduction clinical studies 40% and 16.5% of patients developed antibodies that were cross-reactive to native GIP or native GLP-1, respectively.

Of the ZEPBOUND-treated patients in OSA clinical studies, 37.2% and 19.5% of patients developed antibodies that were cross reactive to native GIP and native GLP-1, respectively.

Neutralizing antibodies against tirzepatide activity on the GIP or GLP-1 receptors and against native GIP or GLP-1 were detected in 2.8% and 2.7% and 0.8% and 0.1% respectively, of ZEPBOUND-treated patients in weight reduction clinical studies.

No ZEPBOUND-treated patients in OSA studies developed neutralizing antibodies against tirzepatide activity on the GIP or GLP-1 receptors or against native GIP or native GLP-1.

No clinically significant effect of anti-tirzepatide antibodies on pharmacokinetics or effectiveness of ZEPBOUND has been identified. More ZEPBOUND-treated patients who developed anti-tirzepatide antibodies experienced hypersensitivity reactions or injection site reactions than those who did not develop these antibodies [see Adverse Reactions (6.1)].

13 NONCLINICAL TOXICOLOGY

13.1 Carcinogenesis, Mutagenesis, Impairment of Fertility

A 2-year carcinogenicity study was conducted with tirzepatide in male and female rats at doses of 0.15, 0.50, and 1.5 mg/kg (0.1-, 0.4-, and 1-fold the MRHD of 15 mg once weekly based on AUC) administered by subcutaneous injection twice weekly. A statistically significant increase in thyroid C-cell adenomas was observed in male rats (≥0.5 mg/kg) and female rats (≥0.15 mg/kg), and a statistically significant increase in thyroid C-cell adenomas and carcinomas combined was observed in male and female rats at all doses examined. In a 6-month carcinogenicity study in rasH2 transgenic mice, tirzepatide at doses of 1, 3, and 10 mg/kg administered by subcutaneous injection twice weekly was not tumorigenic.

Tirzepatide was not genotoxic in a rat bone marrow micronucleus assay.

In fertility and early embryonic development studies, male and female rats were administered twice weekly subcutaneous doses of 0.5, 1.5, or 3 mg/kg (0.3-, 1-, and 2-fold and 0.3-, 0.9-, and 2-fold, respectively, the MRHD of 15 mg once weekly based on AUC). No effects of tirzepatide were observed on sperm morphology, mating, fertility, and conception. In female rats, an increase in the number of females with prolonged diestrus and a decrease in the mean number of corpora lutea resulting in a decrease in the mean number of implantation sites and viable embryos was observed at all dose levels. These effects were considered secondary to the pharmacological effects of tirzepatide on food consumption and body weight.

14 CLINICAL STUDIES

14.1 Weight Reduction and Long-Term Maintenance Studies in Adults with Obesity or Overweight

Weight Reduction in Adults with Obesity or Overweight, with or without Type 2 Diabetes Mellitus (Study 1 and Study 2)

Overview of Study 1 and Study 2

The efficacy of ZEPBOUND for weight reduction in conjunction with a reduced-calorie diet and increased physical activity was studied in two randomized, double-blind, placebo-controlled fixed-dosage trials (Study 1 and Study 2) in adults aged 18 years and older. In Studies 1 and 2, all patients received a standard lifestyle intervention which included instruction on a reduced-calorie diet (approximately 500 kcal/day deficit) and increased physical activity counseling (recommended minimum of 150 min/week) that began with the first dose of study medication or placebo and continued throughout the trial. Patients also received counseling on behavior modification strategies to adhere to diet and exercise recommendations. In both trials, weight reduction was assessed after 72 weeks of treatment (at least 52 weeks at maintenance dose).

Study 1 (NCT04184622) was a 72-week trial that enrolled 2,539 adult patients with obesity (BMI ≥30 kg/m^2), or with overweight (BMI 27 to <30 kg/m^2) and at least one weight-related comorbid condition, such as dyslipidemia, hypertension, obstructive sleep apnea, or cardiovascular disease; patients with type 2 diabetes mellitus were excluded. Patients were randomized in a 1:1:1:1 ratio to once weekly fixed dosage of ZEPBOUND 5 mg, ZEPBOUND 10 mg, ZEPBOUND 15 mg, or placebo, with an escalation period of up to 20 weeks followed by the maintenance period. At baseline, mean age was 45 years (range 18-84 years), 68% were female, 71% were White, 11% were Asian, 9% were American Indian/Alaska Native, and 8% were Black or African American. A total of 48% were Hispanic or Latino ethnicity. Mean baseline body weight was 104.8 kg and mean BMI was 38 kg/m^2. Baseline characteristics included 32% with hypertension, 30% with dyslipidemia, 8% with obstructive sleep apnea, and 3% with cardiovascular disease.

Study 2 (NCT04657003) was a 72-week trial that enrolled 938 adult patients with BMI ≥27 kg/m^2 and type 2 diabetes mellitus. Patients included in the trial had HbA1c 7-10% and were treated with either diet and exercise alone, or any oral anti-hyperglycemic agent except dipeptidyl peptidase-4 (DPP-4) inhibitors or GLP-1 receptor agonists. Patients who were taking insulin or injectable GLP-1 receptor agonists for type 2 diabetes mellitus were excluded. Patients were randomized in a 1:1:1 ratio to once weekly fixed dosage of ZEPBOUND 10 mg, ZEPBOUND 15 mg, or placebo with an escalation period of up to 20 weeks followed by the maintenance period. At baseline, mean age was 54 years (range 18-85 years), 51% were female, 76% were White, 13% were Asian, and 8% were Black or African American. A total of 60% were Hispanic or Latino ethnicity. Mean baseline body weight was 100.7 kg and mean BMI was 36.1 kg/m^2. Baseline characteristics included 66% with hypertension, 61% with dyslipidemia, 8% with obstructive sleep apnea, and 10% with cardiovascular disease.

Results for Study 1 and Study 2

The proportions of patients who discontinued study drug in Study 1 were 14.3%, 16.4%, and 15.1% for the 5 mg, 10 mg, and 15 mg ZEPBOUND-treated groups, respectively, and 26.4% for the placebo-treated group. The proportions of patients who discontinued study drug in Study 2 were 9.3% and 13.8% for the 10 mg and 15 mg ZEPBOUND-treated groups, respectively, and 14.9% for the placebo-treated group.

For Studies 1 and 2, weight reduction was assessed after 72 weeks of treatment (at least 52 weeks at maintenance dose). In both studies, the primary efficacy parameters were mean percent change in body weight and the percentage of patients achieving ≥5% weight reduction from baseline to Week 72 (see Table 2).

After 72 weeks of treatment, ZEPBOUND resulted in a statistically significant reduction in body weight compared with placebo, and greater proportions of patients treated with ZEPBOUND 5 mg, 10 mg, and 15 mg achieved at least 5% weight reduction compared to placebo. Among patients treated with ZEPBOUND 10 mg and 15 mg, greater proportions of patients achieved at least 10%, 15%, and 20% weight reduction compared to placebo (see Table 2). A reduction in body weight was observed with ZEPBOUND irrespective of age, sex, race, ethnicity, baseline BMI, and glycemic status.

Table 2: Changes in Body Weight at Week 72 in Studies 1 and 2 in Patients with Obesity or Overweight
 | Study 1 |  |  |  | Study 2
Intention-to-Treat (ITT) Populationa | Placebo N = 643 | ZEPBOUND 5 mg N = 630 | ZEPBOUND 10 mg N = 636 | ZEPBOUND 15 mg N = 630 | Placebo N = 315 | ZEPBOUND 10 mg N = 312 | ZEPBOUND 15 mg N = 311
Body Weight
Baseline mean (kg) | 104.8 | 102.9 | 105.8 | 105.6 | 101.7 | 100.9 | 99.6
% Change from baselineb | -3.1 | -15.0 | -19.5 | -20.9 | -3.2 | -12.8 | -14.7
% Difference from placebob (95% CI) |  | -11.9 (-13.4, -10.4)d | -16.4 (-17.9, -14.8)d | -17.8 (-19.3, -16.3)d |  | -9.6 (-11.1, -8.1)d | -11.6 (-13.0, -10.1)d
% of Patients losing ≥5% body weight | 34.5 | 85.1 | 88.9 | 90.9 | 32.5 | 79.2 | 82.8
% Difference from placebo (95% CI) |  | 50.3 (44.3, 56.2)c,d | 54.6 (49.1, 60.0)c,d | 56.4 (50.9, 62.0)c,d |  | 46.8 (39.5, 54.1)c,d | 50.4 (43.1, 57.8)c,d
% of Patients losing ≥10% body weight | 18.8 | 68.5 | 78.1 | 83.5 | 9.5 | 60.5 | 64.8
% Difference from placebo (95% CI) |  | 49.3 (43.6, 54.9)c,e | 59.5 (54.2, 64.9)c,d | 64.8 (59.6, 70.1)c,d |  | 51.0 (44.4, 57.7)c,d | 55.3 (48.6, 62.0)c,d
% of Patients losing ≥15% body weight | 8.8 | 48.0 | 66.6 | 70.6 | 2.7 | 39.7 | 48.0
% Difference from placebo (95% CI) |  | 38.7 (33.6, 43.7)c,e | 58.1 (53.2, 63.0)c,d | 62.0 (57.2, 66.8)c,d |  | 37.0 (31.1, 42.9)c,d | 45.4 (39.4, 51.4)c,d
% of Patients losing ≥20% body weight | 3.1 | 30.0 | 50.1 | 56.7 | 1.0 | 21.5 | 30.8
% Difference from placebo (95% CI) |  | 26.6 (22.4, 30.7)c,e | 47.3 (42.7, 51.9)c,d | 53.8 (49.3, 58.3)c,d |  | 20.5 (15.7, 25.4)c,d | 29.7 (24.3, 35.0)c,d
Abbreviations: ANCOVA = analysis of covariance; CI = confidence interval; N = number of patients randomly assigned to study drug.
a The intention-to-treat population includes all randomly assigned patients. For Study 1 at Week 72, body weight was missing for 21.6%, 10.2%, 10.5%, and 9.4% of patients randomly assigned to placebo, ZEPBOUND 5 mg, 10 mg, and 15 mg, respectively. For Study 2 at Week 72, body weight was missing for 11.1%, 4.8%, and 8.4% of patients randomly assigned to placebo, ZEPBOUND 10 mg, and 15 mg, respectively. The missing values were imputed by a hybrid approach using retrieved dropouts from the same treatment group (if missing not due to COVID-19) or using all non-missing data assuming missing at random (for missing solely due to COVID-19).
b Least-squares mean from ANCOVA adjusted for baseline value and other stratification factors.
c Analyzed using logistic regression adjusted for baseline value.
d p-value<0.001 (unadjusted 2-sided) for superiority, controlled for type I error rate.
e Not controlled for type I error rate.

The cumulative frequency distributions of change in body weight are shown in Figure 1 for Study 1 and Figure 2 for Study 2. One way to interpret this figure is to select a change in body weight of interest on the horizontal axis and note the corresponding proportions of patients (vertical axis) in each treatment group who achieved at least that degree of weight reduction. For example, note that the vertical line arising from -10% in Figure 1 intersects the ZEPBOUND 15 mg and placebo curves at approximately 83.5%, and 18.8%, respectively, which correspond to the values shown in Table 2.

Figure 1: Changes in Body Weight (%) from Baseline to Week 72 in Study 1 in Patients with Obesity or Overweight (without Type 2 Diabetes)

Note: Based on average percent weight change of each randomized patient within each specific treatment arm from 100 imputed datasets including observed data and imputed data using hybrid approach for missing values.

Figure 2: Changes in Body Weight (%) from Baseline to Week 72 in Study 2 in Patients with Obesity or Overweight and Type 2 Diabetes

Note: Based on average percent weight change of each randomized patient within each specific treatment arm from 100 imputed datasets including observed data and imputed data using hybrid approach for missing values.

The time courses of weight reduction with ZEPBOUND and placebo from baseline through Week 72 are depicted in Figure 3 for Study 1 and Figure 4 for Study 2.

Figure 3: Change from Baseline (%) in Body Weight in Study 1 in Patients with Obesity or Overweight (without Type 2 Diabetes)

Note: Displayed results are from the Intent-to-Treat Population. (1) Observed mean value from Week 0 to Week 72, and (2) least-squares mean ± standard error at Week 72 hybrid imputation (HI).

Figure 4: Change from Baseline (%) in Body Weight in Study 2 in Patients with Obesity or Overweight and Type 2 Diabetes

Note: Displayed results are from the Intent-to-Treat Population. (1) Observed mean value from Week 0 to Week 72, and (2) least squares mean ± standard error at Week 72 hybrid imputation (HI).

Changes in waist circumference and cardiometabolic parameters with ZEPBOUND are shown in Table 3 for Study 1 and Study 2.

Table 3: Changes in Anthropometry and Cardiometabolic Parameters at Week 72 in Studies 1 and 2 in Patients with Obesity or Overweight
 | Study 1 |  |  |  | Study 2
Intention-to-Treat (ITT) Populationa | Placebo N = 643 | ZEPBOUND 5 mg N = 630 | ZEPBOUND 10 mg N = 636 | ZEPBOUND 15 mg N = 630 | Placebo N = 315 | ZEPBOUND 10 mg N = 312 | ZEPBOUND 15 mg N = 311
Waist Circumference (cm)
Baseline mean | 114.0 | 113.2 | 114.8 | 114.4 | 116.0 | 114.2 | 114.6
Change from baselineb | -4.0 | -14.0 | -17.7 | -18.5 | -3.3 | -10.8 | -13.1
Difference from placebob (95% CI) |  | -10.1 (-11.6, -8.6)e | -13.8 (-15.2, -12.3)d | -14.5 (-15.9, -13.0)d |  | -7.4 (-9.0, -5.9)d | -9.8 (-11.2, -8.3)d
Systolic Blood Pressure (mmHg)
Baseline mean | 122.9 | 123.6 | 123.8 | 123.0 | 131.0 | 130.6 | 130.0
Change from baselineb | -1.0 | -6.6 | -7.7 | -7.4 | -1.2 | -5.6 | -7.1
Difference from placebob (95% CI) |  | -5.6 (-7.2, -3.9)e | -6.7 (-8.4, -5.0)e | -6.4 (-8.0, -4.8)e |  | -4.4 (-6.7, -2.1)e | -5.9 (-8.3, -3.6)e
Diastolic Blood Pressure (mmHg)
Baseline mean | 79.6 | 79.3 | 79.9 | 79.3 | 79.4 | 80.2 | 79.7
Change from baselineb | -0.8 | -4.9 | -5.0 | -4.5 | -0.3 | -2.1 | -2.9
Difference from placebob (95% CI) |  | -4.1 (-5.2, -3.0)e | -4.2 (-5.3, -3.0)e | -3.7 (-4.8, -2.7)e |  | -1.8 (-3.3, -0.4)e | -2.7 (-4.2, -1.2)e
Pulse Rate (beats per minute)
Baseline mean | 72.9 | 72.4 | 71.8 | 72.4 | 74.8 | 75.9 | 75.6
Change from baselinef | 0.1 | 0.6 | 2.3 | 2.6 | -0.5 | 0.6 | 1.0
Difference from placebof (95% CI) |  | 0.5 (-0.5, 1.5)e | 2.2 (1.2, 3.2)e | 2.5 (1.5, 3.4)e |  | 1.2 (-0.1, 2.5)e | 1.5 (0.2, 2.8)e
Total Cholesterol (mg/dL)
Baseline meang | 187.5 | 187.1 | 190.6 | 187.5 | 174.9 | 173.9 | 167.0
% change from baselineb | -1.8 | -3.8 | -4.4 | -6.3 | 2.8 | -2.8 | -1.0
Relative difference from placebob (95% CI) |  | -2.1 (-4.5, 0.4)c,e | -2.7 (-5.1, -0.2)c,e | -4.6 (-6.8, -2.2)c,e |  | -5.5 (-8.7, -2.2)c,e | -3.8 (-7.1, -0.3)c,e
LDL Cholesterol (mg/dL)
Baseline meang | 109.4 | 108.7 | 112.3 | 109.3 | 92.4 | 90.5 | 85.7
% change from baselineb | -1.7 | -4.6 | -5.6 | -7.1 | 7.4 | 1.8 | 4.1
Relative difference from placebob (95% CI) |  | -2.9 (-6.6, 0.9)c,e | -4.0 (-7.5, -0.5)c,e | -5.5 (-8.9, -2.0)c,e |  | -5.2 (-10.1, 0.1)c,e | -3.0 (-8.4, 2.6)c,e
HDL Cholesterol (mg/dL)
Baseline meang | 46.6 | 47.6 | 47.6 | 47.6 | 42.7 | 43.8 | 42.2
% change from baselineb | -0.7 | 6.9 | 9.2 | 8.0 | 0.2 | 8.2 | 9.7
Relative difference from placebob (95% CI) |  | 7.7 (4.6, 10.8)c,e | 9.9 (6.7, 13.2)c,e | 8.7 (5.7, 11.8)c,e |  | 8.0 (4.2, 11.8)c,e | 9.5 (5.6, 13.5)c,e
Non-HDL Cholesterol (mg/dL)
Baseline meang | 138.3 | 137.0 | 140.4 | 137.5 | 129.6 | 127.2 | 121.9
% change from baselineb | -2.3 | -8.0 | -9.4 | -11.7 | 3.7 | -6.6 | -5.2
Relative difference from placebob (95% CI) |  | -5.8 (-8.9, -2.6)c,e | -7.2 (-10.3, -4.1)c,e | -9.6 (-12.4, -6.6)c,e |  | -9.9 (-14.1, -5.6)c,e | -8.5 (-12.9, -4.0)c,e
Triglycerides (mg/dL)
Baseline meang | 130.8 | 128.7 | 125.7 | 128.1 | 165.0 | 158.8 | 158.5
% change from baselineb | -5.6 | -21.2 | -23.8 | -29.1 | -3.3 | -27.1 | -27.3
Relative difference from placebob (95% CI) |  | -16.5 (-21.2, -11.4)c,e | -19.3 (-23.9, -14.4)c,e | -24.9 (-29.1, -20.4)c,e |  | -24.6 (-30.0, -18.7)c,e | -24.8 (-30.3, -18.9)c,e
HbA1c (%)
Baseline mean | 5.6 | 5.6 | 5.5 | 5.6 | 8.0 | 8.0 | 8.1
Change from baselineb | -0.1 | -0.4 | -0.4 | -0.4 | -0.5 | -2.1 | -2.1
Difference from placebob (95% CI) |  | -0.3 (-0.3, -0.2)e | -0.4 (-0.4, -0.3)e | -0.4 (-0.4, -0.3)e |  | -1.6 (-1.7, -1.4)d | -1.6 (-1.8, -1.4)d
Abbreviations: ANCOVA = analysis of covariance; CI = confidence interval; N = number of patients randomly assigned to study drug.
a The intention-to-treat population includes all randomly assigned patients. The missing values were imputed by a hybrid approach using retrieved dropouts from the same treatment group (if missing not due to COVID-19) or using all non-missing data assuming missing at random (for missing solely due to COVID-19).
b Least-squares mean from ANCOVA adjusted for baseline value and other stratification factors.
c Analyzed using log-transformed data.
d p-value<0.001 (unadjusted 2-sided) for superiority, controlled for type I error rate.
e Not controlled for type I error rate.
f Least-squares mean from mixed model for repeated measures adjusted for baseline value and other stratification factors.
g Baseline value is the geometric mean.

Weight Reduction Following Intensive Lifestyle Intervention in Adults with Obesity or Overweight (Study 3)

Overview of Study 3

Study 3 (NCT04657016) was an 84-week trial with a 12-week intensive lifestyle intervention lead-in period (Week -12 to Week 0), followed by a 72-week randomized treatment period of ZEPBOUND versus placebo (Week 0 to Week 72) with a standard lifestyle intervention. Only patients who lost ≥5% body weight during the 12-week intensive lifestyle lead-in period entered the 72-week randomized treatment period. The trial initially enrolled 806 adult patients (aged 18 years and older) with obesity (BMI ≥30 kg/m^2), or with overweight (BMI 27 to <30 kg/m^2) and at least one weight-related comorbid condition, such as dyslipidemia, hypertension, obstructive sleep apnea, or cardiovascular disease; patients with type 2 diabetes mellitus were excluded. During the intensive lifestyle intervention lead-in period, lifestyle instruction was delivered 8 times over 12 weeks by a dietician or dietician-equivalent, with all patients receiving instruction to exercise for at least 150 minutes per week and to reduce their caloric intake to approximately 1,200 kcal/day (females) or 1,500 kcal/day (males). Patients also received counseling on behavior modification strategies to adhere to diet and exercise recommendations. At the end of the 12-week intensive lifestyle intervention lead-in period, 579 patients who achieved ≥5% weight reduction were randomized in a 1:1 ratio to ZEPBOUND or placebo for 72 weeks. ZEPBOUND dosages were escalated over a period of up to 20 weeks to a maximum tolerated dosage (MTD) of 10 mg or 15 mg subcutaneous once weekly. During the randomized treatment period, patients received a standard lifestyle instruction every 12 weeks on reduced-calorie diet (approximately 500 kcal/day deficit) and increased physical activity (recommended minimum of 150 min/week) that began with the first dose of ZEPBOUND or placebo and continued throughout the 72-week treatment period; behavior modification strategies were recommended as needed. Weight reduction was assessed after 72 weeks of treatment (at least 52 weeks at maintenance dose).

For the 579 patients who were randomized, mean body weight at enrollment prior to entering the 12-week lifestyle lead-in period (Week -12) was 109.5 kg and mean BMI was 38.6 kg/m^2. At randomization (Week 0), after the 12-week intensive lifestyle lead-in period, mean body weight was 101.9 kg and mean BMI was 35.9 kg/m^2. The mean age of patients randomized to treatment was 46 years (range 18-77 years), 63% were female, 86% were White, 11% were Black or African American, and 1% were Asian. A total of 54% were Hispanic or Latino ethnicity. Baseline characteristics for the 579 randomized patients included 34% with hypertension, 26% with dyslipidemia, 10% with obstructive sleep apnea, and 2% with cardiovascular disease.

Results for Study 3

At the end of the 12-week intensive lifestyle intervention lead-in, for patients who subsequently entered the randomized treatment period (n=579), the average body weight loss due to lifestyle was 6.9% (Week -12 to Week 0). Eighty-six percent (86%) of ZEPBOUND-treated patients had a maximum tolerated dosage of 15 mg weekly based on their final dose during the double-blind treatment period. The time course of weight reduction during the lead-in and from Week 0 to Week 72 with ZEPBOUND and placebo are depicted in Figure 5.

Figure 5: Change in Body Weight (%) After 12-Week Intensive Lifestyle Intervention Lead-In Followed by Randomized Treatment and a Standard Lifestyle Intervention (Study 3) in Patients with Obesity or Overweight

Note: Displayed results are from the randomized Population. (1) Observed mean value from Week -12 to Week 72, and (2) least squares mean ± standard error at Week 72 hybrid imputation (HI). Change from Week -12 is not a primary endpoint in Study 3.

The proportions of patients who discontinued study drug after randomization were 21.3% for the ZEPBOUND-treated group and 30.5% for the placebo-treated group.

For Study 3, the primary efficacy parameters were mean percent change in body weight from randomization (Week 0) to Week 72 and the percentage of patients achieving ≥5% weight reduction from randomization (Week 0) to Week 72. Amongst randomized patients who already lost ≥5% body weight during the 12-week intensive lifestyle lead-in period, subsequent treatment with ZEPBOUND resulted in a statistically significant reduction in body weight compared to placebo from randomization (Week 0) to Week 72. A greater proportion of patients treated with ZEPBOUND achieved at least 5%, 10%, 15%, and 20% weight reduction from Week 0 to Week 72 compared to placebo (see Table 4).

Table 4: Changes in Body Weight After 12-Week Intensive Lifestyle Intervention Lead-In Followed by Randomized Treatment and a Standard Lifestyle Intervention (Study 3) in Patients with Obesity or Overweight
 | Study 3 N = 579a
Body weight
Mean (kg) at Week -12 | 109.5
Intention-to-Treat (ITT) Populationa,b | Placebo N = 292 | ZEPBOUND MTD (10 mg or 15 mg) N = 287
Body Weight
Mean (kg) at Week 0 | 101.3 | 102.5
% Change from randomization at Week 72c | 2.5 | -18.4
% Difference from placebo, at Week 72c (95% CI) |  | -20.8 (-23.2, -18.5)e
% of Patients losing ≥5% body weight | 16.5 | 87.5
% Difference from placebo (95% CI) |  | 71.1 (63.6, 78.5)d,e
% of Patients losing ≥10% body weight | 8.9 | 76.7
% Difference from placebo (95% CI) |  | 67.9 (60.7, 75.1)d,e
% of Patients losing ≥15% body weight | 4.2 | 65.4
% Difference from placebo (95% CI) |  | 61.3 (54.5, 68.1)d,e
% of Patients losing ≥20% body weight | 2.2 | 44.7
% Difference from placebo (95% CI) |  | 42.6 (36.0, 49.1)d,e
Abbreviations: ANCOVA = analysis of covariance; CI = confidence interval; MTD = maximum tolerated dose; N = number of patients randomly assigned to study drug.
a The intent-to-treat population included only randomized patients with ≥5% weight loss at Week 0 after 12 weeks of intensive lifestyle intervention. During the 12-week lead-in period, 227 of 806 patients (28.2%) discontinued from the study. Of these 141 (17.5%) discontinued due to not achieving the randomization criteria of ≥5% weight reduction.
b The intent-to-treat population includes all randomly assigned patients. For Study 3 at Week 72, body weight was missing for 23.6% and 8.7% of patients randomly assigned to placebo and ZEPBOUND MTD (10 or 15 mg). The missing values were imputed by a hybrid approach using retrieved dropouts from the same treatment group (if missing not due to COVID-19) or using all non-missing data assuming missing at random (for missing solely due to COVID-19).
c Least-squares mean from ANCOVA adjusted for baseline value and other stratification factors.
d Analyzed using logistic regression adjusted for baseline value.
e p-value<0.001 (unadjusted 2-sided) for superiority, controlled for type I error rate.

Changes in waist circumference and cardiometabolic parameters are shown in Table 5.

Table 5: Changes in Anthropometry and Cardiometabolic Parameters After 12-Week Intensive Lifestyle Intervention Lead-In Followed by Randomized Treatment and a Standard Lifestyle Intervention (Study 3) in Patients with Obesity or Overweight
Intention-to-Treat (ITT) Populationa | All Randomized Patients N=579 |  | Placebo N=292 |  | ZEPBOUND MTD (10 mg or 15 mg) N=287
Intention-to-Treat (ITT) Populationa | Baseline (Week -12) | Change from Week -12 to Week 0 | Randomization (Week 0) | Change from Week 0 to Week 72 | Randomization (Week 0) | Change from Week 0 to Week 72 | Difference from placebo, Week 0 to Week 72 (95% CI)
Waist circumference (cm)h | 116.1 | -6.7 | 109.6 | 0.2b | 109.3 | -14.6b | -14.8b (-17.2, -12.5)d
Systolic Blood Pressure (mmHg)h | 126.2 | -5.0 | 120.8 | 3.5b | 121.7 | -5.1b | -8.6b (-11.3, -6.0)e
Diastolic Blood Pressure (mmHg)h | 81.7 | -2.9 | 78.3 | 2.1b | 79.3 | -3.2b | -5.3b (-6.9, -3.7)e
Pulse Rate (beats per minute)h | 73.0 | -1.6 | 70.7 | 0.9f | 72.2 | 2.7f | 1.8f (0.3, 3.4)e
HbA1c (%)h | 5.5 | -0.1 | 5.4 | 0.0b | 5.3 | -0.4b | -0.4b (-0.5, -0.3)e
Total Cholesterol (mg/dL)g,h | 190.2 | -8.6 | 181.6 | 4.3 | 181.7 | -2.4 | -6.4b (-9.0, -3.6)c,e
LDL Cholesterol (mg/dL)g,h | 111.6 | -3.5 | 107.5 | 4.4 | 108.0 | -5.6 | -9.6b (-13.7, -5.4)c,e
HDL Cholesterol (mg/dL)g,h | 48.4 | -1.2 | 47.8 | 5.4 | 46.9 | 15.2 | 9.3b (4.5, 14.2)c,e
Non-HDL Cholesterol (mg/dL)g,h | 139.2 | -7.4 | 131.5 | 4.4 | 132.4 | -8.8 | -12.6b (-15.9, -9.3)c,e
Triglycerides (mg/dL)g,h | 123.1 | -19.8 | 108.8 | 2.1 | 111.7 | -23.5 | -25.1b (-30.9, -18.9)c,e
Abbreviations: ANCOVA = analysis of covariance; CI = confidence interval; N = number of patients randomly assigned to study drug.
a The intent-to-treat population included all randomly assigned patients. The missing values were imputed by a hybrid approach using retrieved dropouts from the same treatment group (if missing not due to COVID-19) or using all non-missing data assuming missing at random (for missing solely due to COVID-19).
b Least-squares mean from ANCOVA adjusted for baseline value and other stratification factors.
c Analyzed using log-transformed data.
d p-value<0.001 (unadjusted 2-sided) for superiority, controlled for type I error rate.
e Not controlled for type I error rate.
f Least-squares mean from mixed model for repeated measures adjusted for baseline value and other stratification factors.
g Baseline and randomization values are the geometric mean.
h Observed means are shown for change from Week -12 to Week 0. Least-square means are shown for change from Week 0 to Week 72.

Weight Reduction Following Randomized Withdrawal in Adults with Obesity or Overweight (Study 4)

Overview of Study 4

Study 4 (NCT04660643) was an 88-week randomized withdrawal trial in which all patients received open-label ZEPBOUND during a 36-week lead-in period, followed by randomization to either continue ZEPBOUND or switch to placebo for 52 weeks. The trial enrolled 783 adult patients (aged 18 years and older) with obesity (BMI ≥30 kg/m^2), or with overweight (BMI 27 to <30 kg/m^2) and at least one weight-related comorbid condition, such as dyslipidemia, hypertension, obstructive sleep apnea, or cardiovascular disease; patients with type 2 diabetes mellitus were excluded. All patients received a standard lifestyle intervention which included instruction on a reduced-calorie diet (approximately 500 kcal/day deficit) and increased physical activity counseling (recommended minimum of 150 min/week) that began with the first dose of ZEPBOUND, during the lead-in period, and continued throughout the trial. During the 36-week open-label ZEPBOUND lead-in period, ZEPBOUND dosages were escalated over a period of up to 20 weeks to an MTD of 10 mg or 15 mg subcutaneous once weekly. After the lead-in period, patients were randomized at Week 36 to continue ZEPBOUND or switch to placebo for 52 weeks.

Of the 783 patients who started ZEPBOUND at Week 0, 14.4% discontinued treatment before randomization at Week 36, and adverse events were the most common reason for discontinuation (6.8%). At Week 36, a total of 670 patients were randomized in a 1:1 ratio to ZEPBOUND MTD or placebo for 52 weeks. For the 670 randomized patients, at study entry (Week 0) mean body weight was 107.3 kg and mean BMI was 38.4 kg/m^2, and at randomization (Week 36, after the open-label ZEPBOUND lead-in period) mean body weight was 85.2 kg and mean BMI was 30.5 kg/m^2. Among the randomized patients, the mean age was 49 years (range 19-81 years), 71% were female, 80% were White, 11% were Black or African American, and 7% were Asian. A total of 44% were Hispanic or Latino ethnicity. Baseline characteristics for the 670 randomized patients included 35% with hypertension, 32% with dyslipidemia, 12% with obstructive sleep apnea, and 6% with cardiovascular disease.

Results for Study 4

At the end of the 36-week open-label ZEPBOUND lead-in period, of the 670 randomized patients, 93% were on ZEPBOUND MTD of 15 mg weekly and 7% were on MTD of 10 mg weekly. After open-label ZEPBOUND treatment, randomized patients (n=670) had an average body weight loss of 20.9% (Week 0 to Week 36). The time course of weight reduction from Week 0 through Week 88 is depicted in Figure 6.

Figure 6: Change in Body Weight (%) After 36-Week Open-Label Treatment Followed by Randomized Withdrawal (Study 4) in Patients with Obesity or Overweight

Note: Displayed results are from the randomized population. (1) Displayed results are observed mean value from Week 0 to Week 88 and (2) least squares mean ± standard error at Week 88 hybrid imputation (HI). Change from Week 0 was not a primary endpoint in Study 4.

The proportions of patients who discontinued study drug after randomization at Week 36 were 10.4% for the ZEPBOUND-treated group and 17.9% for the placebo-treated group.

For Study 4, the primary efficacy parameter was mean percent change in body weight from randomization (Week 36) to Week 88. After weight loss with ZEPBOUND treatment during the open-label lead-in period (Week 0 to Week 36), continued treatment with ZEPBOUND from randomization (Week 36) to Week 88 resulted in a statistically significant reduction in body weight compared with placebo (see Table 6).

Table 6: Changes in Body Weight After 36-Week Open-Label Treatment Followed by Randomized Withdrawal (Study 4) in Patients with Obesity or Overweight
 | Study 4 N=670 a
Body weight
Mean at Week 0 (kg) | 107.3
Intention-to-Treat (ITT) Populationa | Placebo N=335 | ZEPBOUND (MTD 10 mg or 15 mg) N=335
Body Weight
Mean at Week 36 (kg) | 85.8 | 84.6
% change from Week 36 at Week 88b | 14.0 | -5.5
% difference from placebo at Week 88 (95% CI)b |  | -19.4 (-21.2, -17.7)c
Abbreviations: ANCOVA = analysis of covariance; CI = confidence interval; MTD = maximum tolerated dose; N = number of patients randomly assigned to study drug.
a The intent-to-treat population included all randomly assigned patients and did not include 113 patients who were enrolled but not randomized. At Week 88, body weight was missing for 13.7% and 7.5% of patients randomly assigned to placebo and ZEPBOUND MTD (10 or 15 mg), respectively. The missing values were imputed by a hybrid approach using retrieved dropouts from the same treatment group (if missing not due to COVID-19) or using all non-missing data assuming missing at random (for missing solely due to COVID-19).
b Least-squares mean from ANCOVA adjusted for baseline value and other stratification factors.
c p-value<0.001 (unadjusted 2-sided) for superiority, controlled for type I error rate.

Changes in waist circumference and cardiometabolic parameters in Study 4 are shown in Table 7.

Table 7: Mean Changes in Anthropometry and Cardiometabolic Parameters After 36-Week Open-Label Treatment Followed by Randomized Withdrawal (Study 4) in Patients with Obesity or Overweight
Intention-to-Treat (ITT) Populationa | All Randomized Patients N=670 |  | Placebo N=335 |  | ZEPBOUND MTD (10 mg or 15 mg) N=335
Intention-to-Treat (ITT) Populationa | Baseline (Week 0) | Change from Week 0 to Week 36 | Randomization (Week 36) | Change from Week 36 to Week 88 | Randomization (Week 36) | Change from Week 36 to Week 88 | Difference from placebo, Week 36 to Week 88 (95% CI)
Waist circumference (cm)h | 115.2 | -17.8 | 98.2 | 7.8b | 96.8 | -4.3b | -12.1b (-13.5, -10.6)d
Systolic Blood Pressure (mmHg)h | 126.1 | -11.2 | 114.8 | 8.2b | 115.0 | 2.0b | -6.2b (-8.2, -4.3)e
Diastolic Blood Pressure (mmHg)h | 80.9 | -5.1 | 76.2 | 3.2b | 75.4 | -0.7b | -3.8b (-5.2, -2.4)e
Pulse Rate (beats per minute)h | 72.5 | 5.0 | 77.8 | -5.2f | 77.1 | -2.1f | 3.1f (1.9, 4.3)e
HbA1c (%)h | 5.5 | -0.5 | 5.0 | 0.3b | 5.1 | -0.0b | -0.3b (-0.3, -0.2)e
Total Cholesterol (mg/dL)g,h | 188.3 | -12.4 | 176.1 | 8.0 | 175.9 | 2.7 | -4.9b (-7.4, -2.4)c,e
LDL Cholesterol (mg/dL)g,h | 108.6 | -1.9 | 107.6 | 3.2 | 105.9 | -3.5 | -6.5b (-10.0, -2.9)c,e
HDL Cholesterol (mg/dL)g,h | 49.9 | -2.7 | 47.3 | 14.8 | 47.7 | 18.7 | 3.4b (0.2, 6.6)c,e
Non-HDL Cholesterol (mg/dL)g,h | 135.8 | -9.8 | 126.3 | 5.1 | 126.0 | -3.4 | -8.1b (-11.3, -4.8)c,e
Triglycerides (mg/dL)g,h | 121.4 | -40.4 | 85.5 | 13.5 | 90.9 | -4.8 | -16.1b (-21.7, -10.0)c,e
Abbreviations: ANCOVA = analysis of covariance; CI = confidence interval; N = number of patients randomly assigned to study drug.
a The intent-to-treat population included all randomly assigned patients. The missing values were imputed by a hybrid approach using retrieved dropouts from the same treatment group (if missing not due to COVID-19) or using all non-missing data assuming missing at random (for missing solely due to COVID-19).
b Least-squares mean from ANCOVA adjusted for baseline value and other stratification factors.
c Analyzed using log-transformed data.
d p-value<0.001 (unadjusted 2-sided) for superiority, controlled for type I error rate.
e Not controlled for type I error rate.
f Least-squares mean from mixed model for repeated measures adjusted for baseline value and other stratification factors.
g Baseline and randomization values are the geometric mean.
h Observed means are shown for change from Week 0 to Week 36. Least-square means are shown for change from Week 36 to Week 88.

14.2 Obstructive Sleep Apnea Studies in Adults with Obesity

Overview of Study 5 and Study 6

The efficacy of ZEPBOUND for moderate to severe obstructive sleep apnea (OSA) (apnea-hypopnea index [AHI] ≥15) in patients with obesity (BMI ≥30 kg/m^2) was evaluated in a master protocol clinical trial (NCT05412004) that included two randomized, double-blind, placebo-controlled trials (Study 5 and Study 6) of 52 weeks duration. The two trials enrolled a total of 469 adult patients.

In Studies 5 and 6, patients were randomized in a 1:1 ratio to receive ZEPBOUND or placebo for 52 weeks. ZEPBOUND dosages were escalated over a period of up to 20 weeks to maximum tolerated dosage (MTD) of 10 mg or 15 mg subcutaneous once weekly [see Dosage and Administration (2.1, 2.2)]. Patients with type 2 diabetes mellitus were excluded and all patients received instruction on a reduced-calorie diet and increased physical activity counseling throughout the study.

Study 5 enrolled 234 adult patients with moderate to severe OSA and obesity who were unable or unwilling to use Positive Airway Pressure (PAP) therapy. Patients had a mean age of 48 years (range: 20 to 76 years), 67% were male, 66% were White, 20% were Asian, 8% were American Indian/Alaska Native, and 6% were Black or African American. A total of 42% were Hispanic or Latino ethnicity.

Study 6 enrolled 235 adult patients with moderate to severe OSA and obesity who were on PAP therapy. Patients had a mean age of 52 years (range: 26 to 79 years), 72% were male, 73% were White, 14% were Asian, 8% were American Indian/Alaska Native, and 5% were Black or African American. A total of 32% were Hispanic or Latino ethnicity.

Table 8 describes the baseline disease characteristics of patients in Studies 5 and 6.

Table 8: Baseline Disease Characteristics of Patients with OSA and Obesity in Study 5 and Study 6
 | Study 5 (N=234) | Study 6 (N=235)
Baseline AHI (events/hour), mean (SD) | 51.5 (31) | 49.5 (26.7)
Moderate OSA, %a | 35.2 | 30.9
Severe OSA, %b | 63.1 | 68.2
ESS Total, mean (SD) | 10.5 (5.2) | 10 (4.6)
Total Hypoxic Burden (% min/hour), mean (SD) | 208.4 (189.1) | 193 (174.6)
BMI (kg/m^2), mean (SD) | 39.1 (7) | 38.7 (6)
Pre-diabetes, % | 65 | 56.6
Hypertension, % | 75.6 | 77.4
Cardiac disorders, % | 10.3 | 11.1
Dyslipidemia, % | 80.8 | 83.8
Abbreviations: AHI = Apnea-Hypopnea Index; BMI = body-mass index; ESS = Epworth Sleepiness Score; OSA = obstructive sleep apnea; SD = standard deviation.
a Moderate OSA was defined as an AHI ≥15 – 30 events/hour on polysomnogram at baseline.
b Severe OSA was defined as an AHI ≥30 events/hour on polysomnogram at baseline.

Results for Study 5 and Study 6

The primary endpoint for Studies 5 and 6 was the change from baseline in the apnea-hypopnea index (AHI) at Week 52. Patients in Study 5 were unable or unwilling to use PAP therapy, and patients in Study 6 were on PAP therapy and instructed to suspend PAP for 7 days prior to assessment of the primary endpoint. The clinical studies for OSA did not evaluate the timing or appropriateness of PAP discontinuation in patients who were previously compliant with PAP therapy.

In Studies 5 and 6, treatment with ZEPBOUND for 52 weeks resulted in a statistically significant reduction in AHI compared with placebo, and greater proportions of patients treated with ZEPBOUND achieved remission or mild non-symptomatic OSA compared to placebo. Table 9 provides the efficacy results for Studies 5 and 6. A reduction in AHI was observed with ZEPBOUND irrespective of age, sex, ethnicity, baseline BMI, or baseline OSA severity. In both Studies 5 and 6, patients treated with ZEPBOUND achieved a greater reduction in systolic blood pressure and high-sensitivity C-reactive protein levels compared to placebo.

Table 9: Changes in Apnea-Hypopnea Index (AHI), Hypoxic Burden, and Body Weight at Week 52 in Study 5 and Study 6
Modified Intent-to-Treat (mITT) Populationa | Study 5 |  | Study 6
Modified Intent-to-Treat (mITT) Populationa | Placebo N = 120 | ZEPBOUND MTD (10 mg or 15 mg) N = 114 | Placebo N = 114 | ZEPBOUND MTD (10 mg or 15 mg) N = 119
AHI (events/hr)
Baseline mean | 50.1 | 52.9 | 53.1 | 46.1
Change from baselineb | -5.3 | -25.3 | -5.5 | -29.3
Difference from placebob (95% CI) | -20 (-25.8, -14.2)e |  | -23.8 (-29.6, -17.9)e
% change in AHI
% change from baselineb | -3 | -50.7 | -2.5 | -58.7
% difference from placebob (95% CI) | -47.7 (-65.8, -29.6)e |  | -56.2 (-73.7, -38.7)e
% of patients with ≥50% reduction in AHId | 19 | 61.2 | 23.3 | 72.4
% difference from placebo (95% CI) | 42.8 (30.8, 54.8)e |  | 48.6 (36.6, 60.7)e
Remission or mild non-symptomatic OSA
% of Patients with AHI <5 or AHI 5-14 and ESS≤10d | 15.9 | 42.2 | 14.3 | 50.2
% difference from placebo (95% CI) | 28.7 (18.3, 39.2)e |  | 33.2 (22.1, 44.3)e
Sleep apnea-specific hypoxic burden (% min/h)
Baseline meanf | 137.8 | 153.6 | 142.1 | 132.2
Change from baselineb | -25.1 | -95.2 | -41.7 | -103
Difference from placebob (95% CI) | -70.1 (-90.9, -49.3)c,e |  | -61.3 (-84.7, -37.9)c,e
Body weight (kg)
Baseline mean | 112.8 | 116.7 | 115.1 | 115.8
% change from baselineb | -1.6 | -17.7 | -2.3 | -19.6
% difference from placebob (95% CI) | -16.1 (-18, -14.2)e |  | -17.3 (-19.3, -15.3)e
Abbreviations: AHI = Apnea-Hypopnea Index; ANCOVA = analysis of covariance; CI = confidence interval; ESS = Epworth Sleepiness Scale; h = hour; MTD = maximum tolerated dose; N = number of participants randomly assigned and received at least 1 dose of study drug.
a Analyses were based on the modified intent-to-treat population which was defined as randomly assigned participants who were exposed to at least 1 dose of study intervention; two participants in Study 6 were randomized but did not receive study drug.
b Least-squares mean from ANCOVA adjusted for baseline values and stratification factors, with multiple imputation for missing data at Week 52.
c Analyzed using log transformed data.
d Calculated by combining proportion of participants achieving target in imputed datasets.
e p-value <0.001 (unadjusted 2-sided) for superiority, controlled for multiplicity.
f Baseline value is the geometric mean.

The time course of change in AHI with ZEPBOUND and placebo from baseline through Week 52 are shown in Figure 7 for Study 5. Similar results were demonstrated for Study 6.

Figure 7: Change from Baseline in Apnea-Hypopnea Index (AHI) Through Week 52 (Study 5)

Abbreviations: AHI = Apnea-Hypopnea Index; ANCOVA = analysis of covariance; MI = multiple imputation; MTD = maximum tolerated dose.

Note: Displayed results are from modified Intent-to-Treat Population. (1) Observed mean value from Week 0 through Week 52, and (2) least squares mean ± standard error at Week 52 from ANCOVA adjusted for baseline values and stratification factors, with multiple imputation of missing data.

Sleep-Related Impairment

In OSA clinical studies (Study 5 and Study 6), ZEPBOUND-treated patients showed improvement in sleep-related impairment compared to those who received placebo. Sleep-related impairment was assessed using the Patient-Reported Outcomes Measurement Information System® (PROMIS) Short Form Sleep-Related Impairment 8a.

16 HOW SUPPLIED/STORAGE AND HANDLING

16.1 How Supplied

ZEPBOUND (tirzepatide) is a clear, colorless to slightly yellow solution available in cartons containing 4 pre-filled single-dose pens, 1 single-dose vial, 4 single-dose vials, 1 multi-dose vial, or 1 single-patient-use KwikPen as follows:

Single-Dose Vial and Prefilled Pen
Strength | 4 pack Single-dose Pen NDC | 1 pack Single-dose Vial NDC | 4 pack Single-dose Vial NDC
2.5 mg/0.5 mL | 0002-2506-80 | 0002-0152-01 | 0002-0152-04
5 mg/0.5 mL | 0002-2495-80 | 0002-0243-01 | 0002-0243-04
7.5 mg/0.5 mL | 0002-2484-80 | 0002-1214-01 | 0002-1214-04
10 mg/0.5 mL | 0002-2471-80 | 0002-1340-01 | 0002-1340-04
12.5 mg/0.5 mL | 0002-2460-80 | 0002-1423-01 | 0002-1423-04
15 mg/0.5 mL | 0002-2457-80 | 0002-2002-01 | 0002-2002-04

Multi-Dose Vial
Doses per Vial | Strength | 1 pack Multi-Dose Vial NDC
4 doses of 2.5 mg/0.6 mL | 10 mg/2.4 mL (4.17 mg/mL) | 0002-6052-11
4 doses of 5 mg/0.6 mL | 20 mg/2.4 mL (8.33 mg/mL) | 0002-6103-11
4 doses of 7.5 mg/0.6 mL | 30 mg/2.4 mL (12.5 mg/mL) | 0002-6210-11
4 doses of 10 mg/0.6 mL | 40 mg/2.4 mL (16.7 mg/mL) | 0002-6304-11
4 doses of 12.5 mg/0.6 mL | 50 mg/2.4 mL (20.8 mg/mL) | 0002-6523-11
4 doses of 15 mg/0.6 mL | 60 mg/2.4 mL (25 mg/mL) | 0002-6612-11

Single-Patient-Use KwikPen (with four weekly doses)
Doses per KwikPen | Strength | 1 pack Single-Patient-Use KwikPen NDC
4 doses of 2.5 mg | 10 mg/2.4 mL (4.17 mg/mL) | 0002-3566-11
4 doses of 5 mg | 20 mg/2.4 mL (8.33 mg/mL) | 0002-3555-11
4 doses of 7.5 mg | 30 mg/2.4 mL (12.5 mg/mL) | 0002-3544-11
4 doses of 10 mg | 40 mg/2.4 mL (16.7 mg/mL) | 0002-3533-11
4 doses of 12.5 mg | 50 mg/2.4 mL (20.8 mg/mL) | 0002-3522-11
4 doses of 15 mg | 60 mg/2.4 mL (25 mg/mL) | 0002-3511-11

16.2 Storage and Handling

- Do not freeze ZEPBOUND. Do not use ZEPBOUND if frozen.
- Protect ZEPBOUND from heat and light.
- Store ZEPBOUND in the original carton to protect from light.

ZEPBOUND Single-dose Pen and Single-dose Vial

- Store ZEPBOUND single-dose pen and single-dose vial in a refrigerator at 2°C to 8°C (36°F to 46°F).
- If needed, each single-dose pen or single-dose vial can be stored unrefrigerated at temperatures not to exceed 30°C (86°F) for up to 21 days. If single-dose pen or single-dose vial is stored at room temperature, it should not be returned to the refrigerator.
- Discard single-dose pen and single-dose vial if not used within 21 days after removing from the refrigerator.

ZEPBOUND Multi-dose Vial or Single-Patient-Use KwikPen

Unopened vial or single-patient-use KwikPen:

- Store unopened multi-dose vial or single-patient-use KwikPen in the refrigerator at 2°C to 8°C (36°F to 46°F). The unopened multi-dose vial or single-patient-use KwikPen can be used until the expiration date on the label if kept in the refrigerator.
- If stored at room temperature [up to 30°C (86°F)], throw away unopened multi-dose vial or single-patient-use KwikPen after 30 days.

After vial or single-patient-use KwikPen has been opened:

- Store opened (in-use) multi-dose vial or single-patient-use KwikPen in the original carton in the refrigerator at 2°C to 8°C (36°F to 46°F) or at room temperature [up to 30°C (86°F)].
- Throw away opened multi-dose vial or single-patient-use KwikPen after a total of 30 days at room temperature, 30 days after first use, or after taking 4 weekly doses, even if there is medicine left in it.

17 PATIENT COUNSELING INFORMATION

Advise the patient to read the FDA-approved patient labeling (Medication Guide and Instructions for Use).

Risk of Thyroid C-Cell Tumors

Inform patients that ZEPBOUND causes thyroid C-cell tumors in rats and that the human relevance of this finding has not been determined. Counsel patients to report symptoms of thyroid tumors (e.g., a lump in the neck, persistent hoarseness, dysphagia, or dyspnea) to their healthcare provider [see Boxed Warning and Warnings and Precautions (5.1)].

Severe Gastrointestinal Adverse Reactions

Inform patients of the potential risk of severe gastrointestinal adverse reactions. Instruct patients to contact their healthcare provider if they have severe or persistent gastrointestinal symptoms [see Warnings and Precautions (5.2)].

Acute Kidney Injury Due to Volume Depletion

Inform patients of the potential risk of acute kidney injury due to dehydration associated with gastrointestinal adverse reactions. Advise patients to take precautions to avoid fluid depletion. Inform patients of the signs and symptoms of acute kidney injury and instruct them to promptly report any of these signs or symptoms or persistent (or extended) nausea, vomiting, and diarrhea to their healthcare provider [see Warnings and Precautions (5.3)].

Acute Gallbladder Disease

Inform patients of the risk of acute gallbladder disease. Instruct patients to contact their healthcare provider for appropriate clinical follow-up if gallbladder disease is suspected [see Warnings and Precautions (5.4)].

Acute Pancreatitis

Inform patients of the potential risk for acute pancreatitis and its symptoms: severe abdominal pain that may radiate to the back, and which may or may not be accompanied by nausea or vomiting. Instruct patients to discontinue ZEPBOUND promptly and contact their healthcare provider if pancreatitis is suspected [see Warnings and Precautions (5.5)].

Hypersensitivity Reactions

Inform patients that serious hypersensitivity reactions have been reported with use of tirzepatide. Advise patients on the symptoms of hypersensitivity reactions and instruct them to stop taking ZEPBOUND and seek medical advice promptly if such symptoms occur [see Warnings and Precautions (5.6)].

Hypoglycemia

Inform patients of the risk of hypoglycemia and educate patients on the signs and symptoms of hypoglycemia. Advise patients on insulin or insulin secretagogue therapy that they may have an increased risk of hypoglycemia when using ZEPBOUND and to report signs and/or symptoms of hypoglycemia to their healthcare provider [see Warnings and Precautions (5.7)].

Diabetic Retinopathy Complications in Patients with Type 2 Diabetes Mellitus

Inform patients with type 2 diabetes mellitus to contact their healthcare provider if changes in vision are experienced during treatment with ZEPBOUND [see Warnings and Precautions (5.8)].

Pulmonary Aspiration During General Anesthesia or Deep Sedation

Inform patients that ZEPBOUND may cause their stomach to empty more slowly which may lead to complications with anesthesia or deep sedation during planned surgeries or procedures. Instruct patients to inform healthcare providers prior to any planned surgeries or procedures if they are taking ZEPBOUND [see Warnings and Precautions (5.9)].

Never Share a ZEPBOUND KwikPen Between Patients

Advise patients that they must never share a ZEPBOUND KwikPen with another person, even if the pen needle is changed, because doing so carries a risk for transmission of blood-borne pathogens [see Warnings and Precautions (5.10)].

Pregnancy

Advise a pregnant patient of the potential risk to a fetus. Advise patients to inform their healthcare provider if they are pregnant or intend to become pregnant during treatment with ZEPBOUND. Advise patients that there will be a pregnancy exposure registry that monitors pregnancy outcomes in women exposed to ZEPBOUND during pregnancy [see Use in Specific Populations (8.1)].

Contraception

Use of ZEPBOUND may reduce the efficacy of oral hormonal contraceptives. Advise patients using oral hormonal contraceptives to switch to a non-oral contraceptive method, or add a barrier method of contraception for 4 weeks after initiation with ZEPBOUND and for 4 weeks after each dose escalation [see Drug Interactions (7.2), Use in Specific Populations (8.3), and Clinical Pharmacology (12.3)].

Administration

Instruct patients how to prepare and administer the correct dose of ZEPBOUND and assess their ability to inject subcutaneously to ensure the proper administration of ZEPBOUND. Instruct patients using ZEPBOUND vials to always use a new syringe and needle for each injection. Use a syringe appropriate for dose administration (e.g., a 1 mL syringe capable of measuring a 0.5 mL or 0.6 mL dose). Inform patients and their caregiver(s) which ZEPBOUND presentation (e.g., vial, prefilled single-dose pen, single-patient-use KwikPen) they will receive and ensure they receive training appropriate for that specific presentation. If the prescribed ZEPBOUND presentation changes, ensure patients and caregivers receive appropriate training and instruct them to consult the Instructions for Use for the newly prescribed presentation. Advise caregivers that ZEPBOUND KwikPen is not recommended for self-administration by those with visual impairment unless their healthcare provider determines the patient can properly administer [see Dosage and Administration (2.4)].

Missed Doses

Inform patients if a dose is missed, it should be administered as soon as possible within 4 days after the missed dose. If more than 4 days have passed, the missed dose should be skipped and the next dose should be administered on the regularly scheduled day. In each case, inform patients to resume their regular once weekly dosing schedule [see Dosage and Administration (2.3)].

Marketed by: Lilly USA, LLC, Indianapolis, IN 46285, USA

Copyright © 2023, 2026, Eli Lilly and Company. All rights reserved.

Pat.: www.lilly.com/patents

ZEP-0013-USPI-20260225

PATIENT MEDICATION GUIDE

Medication Guide
ZEPBOUND® (ZEHP-bownd)
(tirzepatide)
injection, for subcutaneous use

Do not share your ZEPBOUND KwikPen or needles with other people, even if the needle has been changed. You may give other people a serious infection, or get a serious infection from them.

What is the most important information I should know about ZEPBOUND?
ZEPBOUND may cause serious side effects, including:

- Possible thyroid tumors, including cancer. Tell your healthcare provider if you get a lump or swelling in your neck, hoarseness, trouble swallowing, or shortness of breath. These may be symptoms of thyroid cancer. In studies with rats, ZEPBOUND and medicines that work like ZEPBOUND caused thyroid tumors, including thyroid cancer. It is not known if ZEPBOUND will cause thyroid tumors, or a type of thyroid cancer called medullary thyroid carcinoma (MTC) in people.
- Do not use ZEPBOUND if you or any of your family have ever had a type of thyroid cancer called MTC, or if you have an endocrine system condition called Multiple Endocrine Neoplasia syndrome type 2 (MEN 2).

What is ZEPBOUND?

- ZEPBOUND is an injectable prescription medicine used with a reduced-calorie diet and increased physical activity to help adults with:
  - obesity, or some adults with overweight who also have weight-related medical problems, to lose excess body weight and keep the weight off.
  - moderate to severe obstructive sleep apnea (OSA) and obesity to improve their OSA.
- ZEPBOUND contains tirzepatide and should not be used with other tirzepatide-containing products or any GLP-1 receptor agonist medicines.
- It is not known if ZEPBOUND is safe and effective for use in children.

Do not use ZEPBOUND if:

- you or any of your family have ever had a type of thyroid cancer called MTC or if you have an endocrine system condition called MEN 2.
- you have had a serious allergic reaction to tirzepatide or any of the ingredients in ZEPBOUND. See the end of this Medication Guide for a complete list of ingredients in ZEPBOUND. See "What are the possible side effects of ZEPBOUND?" for symptoms of a serious allergic reaction.

Before using ZEPBOUND, tell your healthcare provider about all of your medical conditions, including if you:

- have or have had problems with your pancreas.
- have severe problems with your stomach, such as slowed emptying of your stomach (gastroparesis) or problems with digesting food.
- have a history of diabetic retinopathy.
- are scheduled to have surgery or other procedures that use anesthesia or deep sleepiness (deep sedation).
- are pregnant or plan to become pregnant. ZEPBOUND may harm your unborn baby. Tell your healthcare provider if you become pregnant while using ZEPBOUND.
  - Pregnancy Exposure Registry: There will be a pregnancy exposure registry for women who have taken ZEPBOUND during pregnancy. The purpose of this registry is to collect information about the health of you and your baby. Talk to your healthcare provider about how you can take part in this registry, or you may contact Eli Lilly and Company at 1-800-LillyRx (1-800-545-5979).
  - Birth control pills by mouth may not work as well while using ZEPBOUND. If you take birth control pills by mouth, your healthcare provider may recommend another type of birth control for 4 weeks after you start ZEPBOUND and for 4 weeks after each increase in your dose of ZEPBOUND. Talk to your healthcare provider about birth control methods that may be right for you while using ZEPBOUND.
- are breastfeeding or plan to breastfeed. ZEPBOUND may pass into your breast milk. Talk to your healthcare provider about the best way to feed your baby while using ZEPBOUND.

Tell your healthcare provider about all the medicines you take, including prescription and over-the-counter medicines, vitamins, and herbal supplements. ZEPBOUND may affect the way some medicines work, and some medicines may affect the way ZEPBOUND works.
Before using ZEPBOUND, talk to your healthcare provider about low blood sugar and how to manage it. Tell your healthcare provider if you are taking medicines to treat diabetes including an insulin or sulfonylurea.
Know the medicines you take. Keep a list of them to show your healthcare provider and pharmacist when you get a new medicine.

How should I use ZEPBOUND?

- Read the Instructions for Use that comes with ZEPBOUND.
- Use ZEPBOUND exactly as your healthcare provider tells you to.
- Your healthcare provider should show you how to prepare to inject your dose of ZEPBOUND before injecting the first time.
- A caregiver may give you ZEPBOUND injections or you may self-inject if a healthcare provider determines that it is appropriate.
- Self-injection is not recommended for people who are visually impaired.
- Use ZEPBOUND with a reduced-calorie diet and increased physical activity.
- If using ZEPBOUND vials, always use a new syringe and needle for each injection.
- Inject ZEPBOUND under the skin (subcutaneously) of your stomach (abdomen), thigh, or another person should inject in the back of the upper arm. Do not inject ZEPBOUND into a muscle (intramuscularly) or vein (intravenously).
- Use ZEPBOUND 1 time each week, at any time of the day.
- You may change the day of the week you use ZEPBOUND as long as the time between the 2 doses is at least 3 days (72 hours).
- If you miss a dose of ZEPBOUND, take the missed dose as soon as possible within 4 days (96 hours) after the missed dose. If more than 4 days have passed, skip the missed dose and take your next dose on the regularly scheduled day. Do not take 2 doses of ZEPBOUND within 3 days (72 hours) of each other.
- ZEPBOUND may be taken with or without food.
- Change (rotate) your injection site with each weekly injection. You may use the same area of your body but be sure to choose a different injection site in that area. Do not use the same site for each injection.
- If you take too much ZEPBOUND, call your healthcare provider or Poison Help line at 1-800-222-1222 or go to the nearest hospital emergency room right away.

What are the possible side effects of ZEPBOUND?
ZEPBOUND may cause serious side effects, including:

- See “What is the most important information I should know about ZEPBOUND?”
- severe stomach problems. Stomach problems, sometimes severe, have been reported in people who use ZEPBOUND. Tell your healthcare provider if you have stomach problems that are severe or will not go away.
- dehydration leading to kidney problems. Diarrhea, nausea, and vomiting may cause a loss of fluids (dehydration) which may cause kidney problems. It is important for you to drink fluids to help reduce your chance of dehydration. Tell your healthcare provider right away if you have nausea, vomiting, or diarrhea that does not go away.
- gallbladder problems. Gallbladder problems have happened in some people who use ZEPBOUND. Tell your healthcare provider right away if you get symptoms of gallbladder problems which may include:
  - pain in your upper stomach (abdomen)
  - fever
  - yellowing of skin or eyes (jaundice)
  - clay-colored stools
- inflammation of your pancreas (pancreatitis). Stop using ZEPBOUND and call your healthcare provider right away if you have severe pain in your stomach area (abdomen) that will not go away, with or without nausea or vomiting. Sometimes you may feel the pain from your abdomen to your back.
- serious allergic reactions. Stop using ZEPBOUND and get medical help right away if you have any symptoms of a serious allergic reaction including:
  - swelling of your face, lips, tongue or throat
  - problems breathing or swallowing
  - severe rash or itching
  - fainting or feeling dizzy
  - very rapid heartbeat
- low blood sugar (hypoglycemia). Your risk for getting low blood sugar may be higher if you use ZEPBOUND with medicines that can cause low blood sugar, such as an insulin or sulfonylurea.
  Signs and symptoms of low blood sugar may include:
  - dizziness or light-headedness
  - sweating
  - confusion or drowsiness
  - headache
  - blurred vision
  - slurred speech
  - shakiness
  - fast heartbeat
  - anxiety, irritability, or mood changes
  - hunger
  - weakness
  - feeling jittery
- changes in vision in patients with type 2 diabetes. Tell your healthcare provider if you have changes in vision during treatment with ZEPBOUND.
- food or liquid getting into the lungs during surgery or other procedures that use anesthesia or deep sleepiness (deep sedation). ZEPBOUND may increase the chance of food getting into your lungs during surgery or other procedures. Tell all your healthcare providers that you are taking ZEPBOUND before you are scheduled to have surgery or other procedures.

The most common side effects of ZEPBOUND include:

- nausea
- diarrhea
- vomiting
- constipation

- stomach (abdominal) pain
- indigestion
- injection site reactions
- feeling tired

- allergic reactions
- belching
- hair loss
- heartburn

Talk to your healthcare provider if you have any side effect that bothers you or that does not go away. These are not all the possible side effects of ZEPBOUND. Call your doctor for medical advice about side effects. You may report side effects to FDA at 1-800-FDA-1088.

How should I store ZEPBOUND?

- Store ZEPBOUND in the original carton to protect it from light.
- Do not freeze ZEPBOUND. Do not use ZEPBOUND if frozen.
- Store single-dose pen and single-dose vial in the refrigerator between 36°F to 46°F (2°C to 8°C). If needed, each single-dose pen or single-dose vial can be stored at room temperature up to 86°F (30°C) for up to 21 days. If single-dose pen or single-dose vial is stored at room temperature, it should not be returned to the refrigerator. Throw away single-dose pen or single-dose vial if not used within 21 days after removing from the refrigerator.
- Store multi-dose vial or single-patient-use KwikPen in the refrigerator between 36°F to 46°F (2°C to 8°C) or at room temperature [up to 86°F (30°C)]. Throw away the multi-dose vial or single-patient-use KwikPen after a total of 30 days at room temperature, 30 days after first use, or after taking 4 weekly doses, even if it still has medicine in it.

Keep ZEPBOUND and all medicines out of the reach of children.

General information about the safe and effective use of ZEPBOUND.
Medicines are sometimes prescribed for purposes other than those listed in a Medication Guide. Do not use ZEPBOUND for a condition for which it was not prescribed. Do not give ZEPBOUND to other people, even if they have the same condition you have. It may harm them. You can ask your pharmacist or healthcare provider for information about ZEPBOUND that is written for health professionals.

What are the ingredients in ZEPBOUND?
Active ingredient: tirzepatide
Inactive ingredients: sodium chloride, sodium phosphate dibasic heptahydrate, and water for injection. Benzyl alcohol, glycerin, and phenol are also inactive ingredients in the multi-dose vial and single-patient-use KwikPen. Hydrochloric acid solution and/or sodium hydroxide solution may have been added to adjust the pH.
ZEPBOUND® and KwikPen® are registered trademarks of Eli Lilly and Company.
Marketed by: Lilly USA, LLC, Indianapolis, IN 46285, USA
Copyright © 2023, 2026, Eli Lilly and Company. All rights reserved.
For more information, go to www.zepbound.com or call 1-800-545-5979.

This Medication Guide has been approved by the U.S. Food and Drug Administration.

Revised: 02/2026

ZEP-0008-MG-20260225

SINGLE-DOSE PEN INSTRUCTIONS FOR USE

INSTRUCTIONS FOR USE
ZEPBOUNDTM (ZEHP-bownd)
(tirzepatide)
injection, for subcutaneous use
2.5 mg/0.5 mL single-dose pen
5 mg/0.5 mL single-dose pen
7.5 mg/0.5 mL single-dose pen
10 mg/0.5 mL single-dose pen
12.5 mg/0.5 mL single-dose pen
15 mg/0.5 mL single-dose pen
use 1 time each week

Important information you need to know before injecting ZEPBOUND

Read this Instructions for Use and the Medication Guide before using your ZEPBOUND pen and each time you get a refill. There may be new information. This information does not take the place of talking to your healthcare provider about your medical condition or treatment.

Talk to your healthcare provider about how to inject ZEPBOUND the right way.

- ZEPBOUND is a single-dose prefilled pen.
- ZEPBOUND is used 1 time each week.
- Inject under the skin (subcutaneously) only.
- You or another person can inject into your stomach (abdomen) or thigh.
- Another person can inject into the back of your upper arm.

Guide to parts

Preparing to inject ZEPBOUND

Remove the pen from the refrigerator.
Leave the gray base cap on until you are ready to inject.

Check the pen label to make sure you have the right medicine and dose, and that it has not expired.
Inspect the pen to make sure that it is not damaged.

Make sure the medicine:

- is not frozen
- is not cloudy

- is colorless to slightly yellow
- does not have particles

Wash your hands.

Step
1

Choose your injection site

Your healthcare provider can help you choose the injection site that is best for you.
You or another person can inject the medicine in your stomach (abdomen) or thigh.

Another person should give you the injection in the back of your upper arm.
Change (rotate) your injection site each week.
You may use the same area of your body but be sure to choose a different injection site in that area.

Step
2

Pull off the gray base cap

Make sure the pen is locked.
Do not unlock the pen until you place the clear base on your skin and are ready to inject.

Pull the gray base cap straight off and throw it away in your household trash.
Do not put the gray base cap back on – this could damage the needle.
Do not touch the needle.

Step
3

Place clear base on skin, then unlock

Place the clear base flat against your skin at the injection site.

Unlock by turning the lock ring.

Step
4

Press and hold up to 10 seconds

Press and hold the purple injection button for up to 10 seconds.
Listen for:

- First click = injection started
- Second click = injection completed

You will know your injection is complete when the gray plunger is visible.

After your injection, place the used pen in a sharps container.

See Disposing of your used pen.

Disposing of your used pen

- Put your used pen in an FDA-cleared sharps disposal container right away after use. Do not throw away (dispose of) pens in your household trash.
- If you do not have an FDA-cleared sharps disposal container, you may use a household container that is:
  - made of a heavy-duty plastic,
  - can be closed with a tight-fitting, puncture-resistant lid, without sharps being able to come out,
  - upright and stable during use,
  - leak-resistant, and
  - properly labeled to warn of hazardous waste inside the container.
- When your sharps disposal container is almost full, you will need to follow your community guidelines for the right way to dispose of your sharps disposal container. There may be state or local laws about how you should throw away used needles and syringes. For more information about safe sharps disposal, and for specific information about sharps disposal in the state that you live in, go to the FDA's website at: http://www.fda.gov/safesharpsdisposal.
- Do not recycle your used sharps disposal container.

Storage and handling

- Store your pen in the refrigerator between 36°F to 46°F (2°C to 8°C).
- You may store your pen at room temperature up to 86°F (30°C) for up to 21 days. If you store the pen at room temperature, do not return the pen to the refrigerator.
- Discard the pen if not used within 21 days after removing from the refrigerator.
- Do not freeze your pen. If the pen has been frozen, throw the pen away and use a new pen.
- Store your pen in the original carton to protect your pen from light.
- The pen has glass parts. Handle it carefully. If you drop the pen on a hard surface, do not use it. Use a new pen for your injection.
- Keep your ZEPBOUND pen and all medicines out of the reach of children.

Commonly asked questions

What if I see air bubbles in my pen?

Air bubbles are normal.

What if my pen is not at room temperature?

It is not necessary to warm the pen to room temperature.

What if I unlock the pen and press the purple injection button before pulling off the gray base cap?

Do not remove the gray base cap. Throw away the pen and get a new pen.

What if there is a drop of liquid on the tip of the needle when I remove the gray base cap?

A drop of liquid on the tip of the needle is normal. Do not touch the needle.

Do I need to hold the injection button down until the injection is complete?

This is not necessary, but it may help you keep the pen steady against your skin.

I heard more than 2 clicks during my injection—2 loud clicks and 1 soft one. Did I get my complete injection?

Some people may hear a soft click right before the second loud click. That is the normal operation of the pen. Do not remove the pen from your skin until you hear the second loud click.

I am not sure if my pen worked the right way.

Check to see if you have received your dose. Your dose was delivered the right way if the gray plunger is visible. Also, see Step 4 of the instructions.
If you do not see the gray plunger, contact Lilly at 1-800-Lilly-Rx (1-800-545-5979) for further instructions. Until then, store your pen safely to avoid an accidental needle stick.

What if there is a drop of liquid or blood on my skin after my injection?

This is normal. Press a cotton ball or gauze over the injection site. Do not rub the injection site.

Other information

- If you have vision problems, do not use your pen without help from a person trained to use the ZEPBOUND pen.

Where to learn more

- If you have questions or problems with your ZEPBOUND pen, contact Lilly at 1-800-Lilly-Rx (1-800-545-5979) or call your healthcare provider.
- For more information about the ZEPBOUND pen, visit our website at www.zepbound.com.

Scan this code to launch
www.zepbound.com

Marketed by:
Lilly USA, LLC
Indianapolis, IN 46285, USA

ZEPBOUND is a trademark of Eli Lilly and Company.

Copyright © 2023, Eli Lilly and Company. All rights reserved.

This Instructions for Use has been approved by the U.S. Food and Drug Administration. Revised: November 2023

ZEP-0002-PEN-IFU-20231109

SINGLE-DOSE VIAL INSTRUCTIONS FOR USE

INSTRUCTIONS FOR USE
ZEPBOUND® [ZEHP-bownd]
(tirzepatide)
injection, for subcutaneous use
2.5 mg/0.5 mL single-dose vial
5 mg/0.5 mL single-dose vial
7.5 mg/0.5 mL single-dose vial
10 mg/0.5 mL single-dose vial
12.5 mg/0.5 mL single-dose vial
15 mg/0.5 mL single-dose vial

Important information you need to know before injecting ZEPBOUND

Read this Instructions for Use before you start taking ZEPBOUND and each time you get a new vial. There may be new information. This information does not take the place of talking to your healthcare provider about your medical condition or your treatment.

Do not share your needles or syringes with other people. You may give other people a serious infection or get a serious infection from them.

Talk to your healthcare provider about how to inject ZEPBOUND the right way.

- ZEPBOUND is a single-dose vial.
- ZEPBOUND is used 1 time each week.
- Inject under the skin (subcutaneously) only.
- You or another person may inject into your stomach (abdomen) or thigh.
- Another person can inject into the back of your upper arm.

Gather supplies needed to give your injection

- 1 single-dose ZEPBOUND vial
- 1 syringe and 1 needle, supplied separately (for example, use a 1 mL syringe and needle as recommended by your healthcare provider)
- 1 alcohol swab
- gauze
- 1 sharps container for throwing away used needles and syringes. See “Disposing of used needles and syringes” at the end of these instructions.

Guide to parts
Vial

Needle and Syringe (not included)

Note: The needle and syringe are not included. The needle and syringe recommended by your healthcare provider may look different than the needle and syringe in this Instructions for Use.

Preparing to inject ZEPBOUND

Remove the vial from the refrigerator.

Check the vial label to make sure you have the right medicine and dose, and that it has not expired.

Make sure the medicine:

- is not frozen
- is not cloudy

- is colorless to slightly yellow
- does not have particles

Always use a new syringe and needle for each injection to prevent infections and blocked needles. Do not reuse or share your syringes or needles with other people. You may give other people a serious infection or get a serious infection from them.

Wash your hands with soap and water.

Step 1:
Pull off the plastic protective cap. Do not remove the rubber stopper.

Step 2:
Wipe the rubber stopper with an alcohol swab.

Step 3:
Remove the outer wrapping from the syringe.

Step 4:
Remove the outer wrapping from the needle.
The syringe that your healthcare provider recommended may have a pre-attached needle. If the needle is attached, skip to step 6.

Step 5:
Place the needle on top of the syringe and turn until it is tight and firmly attached.

Step 6:
Remove the needle shield by pulling straight off.

Step 7:
Hold the syringe in one hand with the needle pointing up. With the other hand pull down on the plunger until the plunger tip reaches the line on the syringe indicating that 0.5 mL of air has been drawn into the syringe.

Step 8:
Push the needle through the rubber stopper of the vial.

Step 9:
Push the plunger all the way in. This puts air into the vial and makes it easier to pull the solution from the vial.

Step 10:
Turn the vial and syringe upside down. Make sure that the tip of the needle is in the liquid and slowly pull the plunger down until the plunger tip is past the 0.5 mL line.
If there are air bubbles, tap the syringe gently a few times to let any air bubbles rise to the top.

Step 11:
Slowly push the plunger up until the plunger tip reaches the 0.5 mL line.

Step 12:
Pull the syringe out of the rubber stopper of the vial.

Injecting ZEPBOUND

- Inject exactly as your healthcare provider has shown you. Your healthcare provider should tell you if you should pinch the skin before injecting.
- Change (rotate) your injection site within the area you choose for each dose to reduce your risk of getting lipodystrophy (pits in skin or thickened skin) and localized cutaneous amyloidosis (skin with lumps) at the injection sites.
- Do not inject where the skin has pits, is thickened, or has lumps.
- Do not inject where the skin is tender, bruised, scaly or hard, or into scars or damaged skin.
- Do not mix ZEPBOUND with any other medicine.
- Do not inject ZEPBOUND in the same injection site used for other medicines.

Step 13:
Choose your injection site.
You can inject ZEPBOUND under the skin (subcutaneously) of your stomach area (abdomen) or thighs.
Someone else can inject in your stomach area, thighs, or the back of the upper arms.

Step 14:
Insert the needle into your skin.

Step 15:
Push down on the plunger to inject your dose.
The needle should stay in your skin for at least 5 seconds to make sure you have injected all of your dose.

Step 16:
Pull the needle out of your skin.

- If you see blood after you take the needle out of your skin, press the injection site with a piece of gauze or an alcohol swab. Do not rub the area.
- Do not recap the needle. Recapping the needle can lead to a needle stick injury.

Disposing of used needles and syringes

- Put your used needle and syringe in an FDA-cleared sharps disposal container right away after use. Do not throw away (dispose of) loose needles and syringes in your household trash.
- If you do not have an FDA-cleared sharps disposal container, you may use a household container that is:
  - made of a heavy-duty plastic,
  - can be closed with a tight-fitting, puncture-resistant lid, without sharps being able to come out,
  - upright and stable during use,
  - leak-resistant, and
  - properly labeled to warn of hazardous waste inside the container.
- When your sharps disposal container is almost full, you will need to follow your community guidelines for the right way to dispose of your sharps disposal container. There may be state or local laws about how you should throw away used needles and syringes. For more information about safe sharps disposal, and for specific information about sharps disposal in the state that you live in, go to the FDA’s website at:
  http://www.fda.gov/safesharpsdisposal.
- Do not dispose of your used sharps disposal container in your household trash unless your community guidelines permit this. Do not recycle your used sharps disposal container.

Storing ZEPBOUND

- Store all unopened vials in the refrigerator at 36°F to 46°F (2°C to 8°C).
- You may store the unopened vial at room temperature up to 86°F (30°C) for up to 21 days.
- Do not freeze. Do not use if ZEPBOUND has been frozen.
- Store the vial in the original carton to protect from light.
- Throw away all opened vials after use, even if there is medicine left in the vial.

Keep ZEPBOUND vials, syringes, needles, and all medicines out of the reach of children.

If you have any questions or problems with your ZEPBOUND, contact Lilly at 1-800-Lilly-Rx (1-800-545-5979) or call your healthcare provider for help.

Marketed by:
Lilly USA, LLC
Indianapolis, IN 46285, USA

ZEPBOUND is a registered trademark of Eli Lilly and Company.

Copyright © 2024, Eli Lilly and Company. All rights reserved.

ZEP-0001-VL-IFU-20240328

This Instructions for Use has been approved by the U.S. Food and Drug Administration.

Issued: March 2024

MULTIPLE-DOSE VIAL INSTRUCTIONS FOR USE

INSTRUCTIONS FOR USE

ZEPBOUND® [ZEHP-bownd]

(tirzepatide)

injection, for subcutaneous use

Multi-dose vial

Each vial contains 4 doses, one dose taken weekly.

Important information you need to know before injecting ZEPBOUND

Read this Instructions for Use before you start taking ZEPBOUND and each time you get a new vial. There may be new information. This information does not take the place of talking to your healthcare provider about your medical condition or your treatment.

Do not share your needles or syringes with other people.

Talk to your healthcare provider about how to inject ZEPBOUND the right way.

- ZEPBOUND is a multi-dose vial. The vial contains 4 doses, one dose taken weekly.
- Inject 0.6 mL in a single weekly injection, under the skin (subcutaneously).
- You or another person may inject into your stomach (abdomen) or thigh.
- Another person can inject into the back of your upper arm.

Gather supplies needed to give your injection

- 1 multi-dose ZEPBOUND vial
- 1 syringe and 1 needle, supplied separately (for example, use a 1 mL syringe and needle as recommended by your healthcare provider)
- 1 alcohol swab
- gauze
- 1 sharps container for throwing away used needles and syringes. See “Disposing of used needles and syringes” at the end of these instructions.

Guide to parts

Vial

Needle and Syringe (not included)

Note: The needle and syringe are not included. The needle and syringe recommended by your healthcare provider may look different than the needle and syringe in this Instructions for Use.

Preparing to inject ZEPBOUND

Check the vial label to make sure you have the right medicine and dose, and that it has not expired.

Make sure the medicine:

- is not frozen
- is not cloudy

- is colorless to slightly yellow
- does not have particles

Always use a new syringe and needle for each injection to prevent infections and blocked needles. Do not reuse or share your syringes or needles with other people. You may give other people a serious infection or get a serious infection from them.

Wash your hands with soap and water.

Step 1:
If you are using a new vial, pull off the plastic protective cap. Do not remove the rubber stopper.

Step 2:
Wipe the rubber stopper with an alcohol swab.

Step 3:
Remove the outer wrapping from the syringe.

Step 4:
Remove the outer wrapping from the needle.
The syringe that your healthcare provider recommended may have a pre-attached needle. If the needle is attached, skip to step 6.

Step 5:
Place the needle on top of the syringe and turn until it is tight and firmly attached.

Step 6:
Remove the needle shield by pulling straight off.

Step 7:
Hold the syringe in one hand with the needle pointing up. With the other hand pull down on the plunger until the plunger tip reaches the line on the syringe indicating that 0.6 mL of air has been drawn into the syringe.

Step 8:
Push the needle through the rubber stopper of the vial.

Step 9:
Push the plunger all the way in. This puts air into the vial and makes it easier to pull the solution from the vial.

Step 10:
Turn the vial and syringe upside down. Make sure that the tip of the needle is in the liquid and slowly pull the plunger down until the plunger tip is past the 0.6 mL line.
If there are air bubbles, tap the syringe gently a few times to let any air bubbles rise to the top.

Step 11:
Slowly push the plunger up until the plunger tip reaches the 0.6 mL line.

Step 12:
Pull the syringe out of the rubber stopper of the vial.

Injecting ZEPBOUND

- Inject exactly as your healthcare provider has shown you. Your healthcare provider should tell you if you should pinch the skin before injecting.
- Change (rotate) your injection site within the area you choose for each dose to reduce your risk of getting lipodystrophy (pits in skin or thickened skin) and localized cutaneous amyloidosis (skin with lumps) at the injection sites.
- Do not inject where the skin has pits, is thickened, or has lumps.
- Do not inject where the skin is tender, bruised, scaly or hard, or into scars or damaged skin.
- Do not mix ZEPBOUND with any other medicine.
- Do not inject ZEPBOUND in the same injection site used for other medicines.

Step 13:
Choose your injection site.
You can inject ZEPBOUND under the skin (subcutaneously) of your stomach area (abdomen) or thighs.
Someone else can inject in your stomach area, thighs, or the back of the upper arms.

Step 14:
Insert the needle into your skin.

Step 15:
Push down on the plunger to inject your dose.
The needle should stay in your skin for at least 5 seconds to make sure you have injected all of your dose.

Step 16:
Pull the needle out of your skin.

- If you see blood after you take the needle out of your skin, press the injection site with a piece of gauze. Do not rub the area.
- Do not recap the needle. Recapping the needle can lead to a needle stick injury.

Disposing of used needles and syringes

- Put your used needle and syringe in an FDA-cleared sharps disposal container right away after use. Do not throw away (dispose of) loose needles and syringes in your household trash.
- If you do not have an FDA-cleared sharps disposal container, you may use a household container that is:
  - made of a heavy-duty plastic,
  - can be closed with a tight-fitting, puncture-resistant lid, without sharps being able to come out,
  - upright and stable during use,
  - leak-resistant, and
  - properly labeled to warn of hazardous waste inside the container.
- When your sharps disposal container is almost full, you will need to follow your community guidelines for the right way to dispose of your sharps disposal container. There may be state or local laws about how you should throw away used needles and syringes. For more information about safe sharps disposal, and for specific information about sharps disposal in the state that you live in, go to the FDA's website at:
  http://www.fda.gov/safesharpsdisposal.
- Do not dispose of your used sharps disposal container in your household trash unless your community guidelines permit this. Do not recycle your used sharps disposal container.

Storing ZEPBOUND

- Do not freeze. Do not use if ZEPBOUND has been frozen.
- Store ZEPBOUND in original carton. Keep away from light.

Unopened vial:

- Store unopened vial in the refrigerator at 36°F to 46°F (2°C to 8°C). It can be used until the expiration date on the label if kept in the refrigerator.
- If stored at room temperature [up to 86°F (30°C)], throw away unopened vial after 30 days.

After vial has been opened:

- Store opened (in-use) vial in the original carton in the refrigerator at 36°F to 46°F (2°C to 8°C) or at room temperature [up to 86°F (30°C)]. Throw away opened vial after a total of 30 days at room temperature, 30 days after first use, or after taking 4 weekly doses, even if there is medicine left in it.

Keep ZEPBOUND vials, syringes, needles, and all medicines out of the reach of children.

If you have any questions or problems with your ZEPBOUND, contact Lilly at 1-800-Lilly-Rx (1-800-545-5979) or call your healthcare provider for help.

Marketed by:
Lilly USA, LLC
Indianapolis, IN 46285, USA

ZEPBOUND is a registered trademark of Eli Lilly and Company.

Copyright © 2026, Eli Lilly and Company. All rights reserved.

ZEP-0001-MDV-IFU-20260107

This Instructions for Use has been approved by the U.S. Food and Drug Administration .

Revised: January 2026

MULTI-DOSE KWIKPEN INSTRUCTIONS FOR USE

INSTRUCTIONS FOR USE

ZEPBOUND® [ZEHP-bownd] KwikPen® [KWIHK pehn]

(tirzepatide)

injection, for subcutaneous use

multi-dose single-patient-use prefilled pen

Each pen contains 4 fixed doses, one dose taken weekly.

This Instructions for Use contains information on how to inject ZEPBOUND.

Important information you need to know before injecting ZEPBOUND

Read this INSTRUCTIONS FOR USE before you start injecting ZEPBOUND KwikPen (Pen) and each time you get another new Pen. There may be new information. This information does not take the place of talking to your healthcare provider about your medical condition or your treatment.

- ZEPBOUND KwikPen is a disposable multi-dose single-patient-use prefilled pen. The Pen contains 4 fixed doses, one dose taken weekly. Inject in a single weekly injection, under the skin (subcutaneously).
- For your weekly dose, you need to turn the dose knob all the way until it stops AND the icon is in dose window.
- After 4 doses, throw away (discard) the Pen, including the unused medicine. The Pen will prevent you from dialing a full dose after you have given yourself 4 weekly doses. Do not inject the leftover medicine. Do not transfer ZEPBOUND from your Pen into a syringe.
- Do not share your ZEPBOUND Pen with other people, even if the pen needle has been changed. You may give other people a serious infection or get a serious infection from them.
- People who are blind or have vision problems should not use the Pen without help from a person trained to use the Pen.

Guide to parts

Parts of the ZEPBOUND Pen

Supplies needed to give your injection

- ZEPBOUND KwikPen
- KwikPen-compatible Pen Needle (not included)

- Alcohol swab
- Gauze or cotton ball
- FDA-cleared sharps disposal container or household container

Preparing to inject ZEPBOUND

Step 1:

- Wash your hands with soap and water.

Step 2:

- Pull the Pen cap straight off.
- Inspect the Pen and label. Do not use if:
  - the medicine name or dose strength does not match your prescription.
  - the Pen is expired (EXP) or looks damaged.
  - the medicine has been frozen, has particles, is cloudy, or is discolored. ZEPBOUND should be colorless to slightly yellow.

Step 3:

- Wipe the red inner seal with an alcohol swab.

Step 4:

- Select a new pen needle. Always use a new pen needle for each injection to help prevent infections and blocked needles.
- Pull off the paper tab from the outer needle shield.

Step 5:

- Push the capped pen needle straight onto the Pen and twist the pen needle on until it is tight.

Step 6:

1. Pull off the outer needle shield and keep it. This will be reused.
2. Pull off the inner needle shield. Put it in your household trash.

a. Outer needle shield

b. Inner needle shield

Priming your Pen

Prime before each weekly injection. Priming removes air from the cartridge and makes sure that your Pen is working correctly.

Step 7:

- Slowly turn the dose knob until you hear 2 clicks and the extended line is shown in the dose window.
  This is the prime position. It can be corrected by turning the dose knob in either direction until the prime position lines up to the dose indicator.

Step 8:

- Hold your Pen with the needle pointing up.
- Tap the cartridge holder gently to collect air bubbles at the top.

Step 9:

- Release some medicine into the air by pushing the dose knob in until it stops, then slowly count to 5 while holding the dose knob. The icon must be shown in the dose window. Do not inject into your body.
  Your Pen has been primed if a small amount (a drop) of medicine comes out of the tip of the pen needle.
  – If you do not see medicine, repeat steps 7-9, no more than 2 additional times.
  – If you still do not see medicine, then change the pen needle and repeat steps 7-9, no more than 1 additional time.
  – If you still do not see medicine, contact Lilly at 1-800-LillyRx (1-800-545-5979).

Injecting ZEPBOUND

Step 10:

- Choose an injection site.
  1. You or another person can inject the medicine in your thigh or stomach (abdomen) at least 2 inches from the belly button.
  2. Another person should give you the injection in the back of your upper arm.
- Change (rotate) your injection site each week. You may use the same area of your body but be sure to choose a different injection site in that area.

a. Front b. Back

Step 11:

- Turn the dose knob all the way until it stops AND the icon is in the dose window. This is your weekly dose.
  Do not count clicks as you select the dose.

Step 12:

1. Insert the needle into your skin.
2. Inject the medicine by pushing the dose knob in until it stops then slowly count to 5 while holding the dose knob. You may notice the plunger moving with each injection. The icon must be shown in the dose window before removing the needle.

Step 13:

- Pull the needle out of your skin. A drop of medicine on the needle tip is normal. It will not affect your dose.
- Confirm the icon is in the dose window.
  If you see the icon in the dose window, you have received the full dose.
  If you do not see the icon in the dose window, insert the needle back into your skin and finish your injection. Do not redial the dose.
  If you still do not think you received the full dose, do not start over or repeat the injection. See “Troubleshooting” section for more information.

After your ZEPBOUND injection

Step 14:

- If you see blood after you pull the needle out of your skin, lightly press the injection site with gauze or a cotton ball.
  Do not rub the injection site.

Step 15:

- Carefully replace the outer needle shield.

Step 16:

- Unscrew the capped needle and put the needle in a sharps container (see “Disposing of ZEPBOUND KwikPen and pen needles” section).
  Do not store the Pen with the needle attached to prevent leaking, blocking the needle, and air from entering the Pen.

Step 17:

- Replace the Pen cap.
  Do not store the Pen without the Pen cap attached.

Storing your ZEPBOUND KwikPen

Unused Pens:

- Store unused Pens in the refrigerator between 36°F to 46°F (2°C to 8°C).
- Unused Pens may be used until the expiration date (EXP) printed on the label if the Pen has been kept in the refrigerator.
- Do not freeze your Pen. Throw away (discard) the Pen if it has been frozen.

Used Pens:

- You may store your used Pen at room temperature up to 86°F (30°C) after your injection.
- Keep away from heat and light.
- Keep your Pen and needles out of the sight and reach of children.
- Throw away the Pen 30 days after first use even though the Pen has medicine left in it.
- Throw away the Pen after receiving 4 weekly doses. Attempting to inject any leftover medicine could result in an incomplete dose even though the Pen still has medicine left in it.

Disposing of ZEPBOUND KwikPen and pen needles

- Put your used pen needles in an FDA-cleared sharps disposal container right away after use.
- Do not throw away (discard) loose pen needles in your household trash.
- Discard the used Pen in your household trash or FDA-cleared sharps disposal container after you have removed the needle.
- If you do not have an FDA-cleared sharps disposal container, you may use a household container that is:
  - made of a heavy-duty plastic,
  - can be closed with a tight-fitting, puncture-resistant lid, without sharps being able to come out,
  - upright and stable during use,
  - leak-resistant, and
  - properly labeled to warn of hazardous waste inside the container.
- When your sharps disposal container is almost full, you will need to follow your community guidelines for the right way to dispose of your sharps disposal container. There may be state or local laws about how you should throw away (discard) used needles. For more information about safe sharps disposal, and for specific information about sharps disposal in the state you live in, go to the FDA's website at: http://www.fda.gov/safesharpsdisposal.
- Do not dispose of your used sharps disposal container in your household trash unless your community guidelines permit this. Do not recycle your used sharps disposal container.

Troubleshooting

- If you cannot remove the Pen cap, gently twist the Pen cap back and forth, and then pull the Pen cap straight off.
- If the dose knob is hard to push:
  - pushing the dose knob more slowly will make it easier to inject.
  - your needle may be blocked. Put on a new pen needle and prime the Pen.
  - you may have dust, food, or liquid inside the Pen. Throw the Pen away and get a new Pen.
- If the Pen prevents you from turning the dose knob until the is in the dose window:
  - Throw away (discard) the Pen, including the unused medicine. There may not be enough medicine left in the pen to give a full dose. Do not attempt to inject the leftover medicine.

Additional Information:

If you have any questions or problems with ZEPBOUND KwikPen:

- Call your healthcare provider
- Call 1-800-LillyRx (1-800-545-5979)
- Visit www.zepbound.com

Scan this code to launch
www.zepbound.com

ZEPBOUND® and KwikPen® are registered trademarks of Eli Lilly and Company.

Marketed by:
Lilly USA, LLC
Indianapolis, IN 46285, USA

Copyright © 2026, Eli Lilly and Company. All rights reserved.

ZEPBOUND KwikPen meets the current dose accuracy and functional requirements of ISO 11608-1.

This Instructions for Use has been approved by the U.S. Food and Drug Administration.

Revised: January 2026

ZEPKP-0002-IFU-20260121

Medication Calendar

Use ZEPBOUND 1 time a week. Write the day of the week you choose to inject. Inject on this day each week (Example: Monday). |  | I inject my weekly dose on the dates below.
Use ZEPBOUND 1 time a week. Write the day of the week you choose to inject. Inject on this day each week (Example: Monday). |  | (Month/Day) | (Month/Day) | (Month/Day) | (Month/Day)

PACKAGE LABEL - Zepbound Prefilled Pen (Autoinjector) - 2.5 mg/0.5 mL Dose

NDC 0002-2506-80

Zepbound®

(tirzepatide) injection

2.5 mg/0.5 mL

4 x 2.5 mg/0.5 mL prefilled pens

Rx Only

For Subcutaneous Use

Dispense enclosed Medication Guide to each patient.

Use one pen every week.

4 Single-dose prefilled pens

Lilly

PACKAGE LABEL - Zepbound Prefilled Pen (Autoinjector) - 5 mg/0.5 mL Dose

NDC 0002-2495-80

Zepbound®

(tirzepatide) injection

5 mg/0.5 mL

4 x 5 mg/0.5 mL prefilled pens

Rx Only

For Subcutaneous Use

Dispense enclosed Medication Guide to each patient.

Use one pen every week.

4 Single-dose prefilled pens

Lilly

PACKAGE LABEL - Zepbound Prefilled Pen (Autoinjector) - 7.5 mg/0.5 mL Dose

NDC 0002-2484-80

Zepbound®

(tirzepatide) injection

7.5 mg/0.5 mL

4 x 7.5 mg/0.5 mL prefilled pens

Rx Only

For Subcutaneous Use

Dispense enclosed Medication Guide to each patient.

Use one pen every week.

4 Single-dose prefilled pens

Lilly

PACKAGE LABEL - Zepbound Prefilled Pen (Autoinjector) - 10 mg/0.5 mL Dose

NDC 0002-2471-80

Zepbound®

(tirzepatide) injection

10 mg/0.5 mL

4 x 10 mg/0.5 mL prefilled pens

Rx Only

For Subcutaneous Use

Dispense enclosed Medication Guide to each patient.

Use one pen every week.

4 Single-dose prefilled pens

Lilly

PACKAGE LABEL - Zepbound Prefilled Pen (Autoinjector) - 12.5 mg/0.5 mL Dose

NDC 0002-2460-80

Zepbound®

(tirzepatide) injection

12.5 mg/0.5 mL

4 x 12.5 mg/0.5 mL prefilled pens

Rx Only

For Subcutaneous Use

Dispense enclosed Medication Guide to each patient.

Use one pen every week.

4 Single-dose prefilled pens

Lilly

PACKAGE LABEL - Zepbound Prefilled Pen (Autoinjector) - 15 mg/0.5 mL Dose

NDC 0002-2457-80

Zepbound®

(tirzepatide) injection

15 mg/0.5 mL

4 x 15 mg/0.5 mL prefilled pens

Rx Only

For Subcutaneous Use

Dispense enclosed Medication Guide to each patient.

Use one pen every week.

4 Single-dose prefilled pens

Lilly

PACKAGE LABEL - Zepbound Single-Dose Vial - 2.5 mg/0.5 mL Dose

NDC 0002-0152-04

Zepbound®

(tirzepatide) injection

2.5 mg/0.5 mL

Rx Only

For Subcutaneous Use

Needles and Syringes are not included

Dispense enclosed Medication Guide to each patient.

Use one vial every week.

4 Single-dose vials

Discard unused portion

Lilly

PACKAGE LABEL - Zepbound Single-Dose Vial - 5 mg/0.5 mL Dose

NDC 0002-0243-04

Zepbound®

(tirzepatide) injection

5 mg/0.5 mL

Rx Only

For Subcutaneous Use

Needles and Syringes are not included

Dispense enclosed Medication Guide to each patient.

Use one vial every week.

4 Single-dose vials

Discard unused portion

Lilly

PACKAGE LABEL - Zepbound Single-Dose Vial - 7.5 mg/0.5 mL Dose

NDC 0002-1214-04

Zepbound®

(tirzepatide) injection

7.5 mg/0.5 mL

Rx Only

For Subcutaneous Use

Needles and Syringes are not included

Dispense enclosed Medication Guide to each patient.

Use one vial every week.

4 Single-dose vials

Discard unused portion

Lilly

PACKAGE LABEL - Zepbound Single-Dose Vial - 10 mg/0.5 mL Dose

NDC 0002-1340-04

Zepbound®

(tirzepatide) injection

10 mg/0.5 mL

Rx Only

For Subcutaneous Use

Needles and Syringes are not included

Dispense enclosed Medication Guide to each patient.

Use one vial every week.

4 Single-dose vials

Discard unused portion

Lilly

PACKAGE LABEL - Zepbound Single-Dose Vial - 12.5 mg/0.5 mL Dose

NDC 0002-1423-04

Zepbound®

(tirzepatide) injection

12.5 mg/0.5 mL

Rx Only

For Subcutaneous Use

Needles and Syringes are not included

Dispense enclosed Medication Guide to each patient.

Use one vial every week.

4 Single-dose vials

Discard unused portion

Lilly

PACKAGE LABEL - Zepbound Single-Dose Vial - 15 mg/0.5 mL Dose

NDC 0002-2002-04

Zepbound®

(tirzepatide) injection

15 mg/0.5 mL

Rx Only

For Subcutaneous Use

Needles and Syringes are not included

Dispense enclosed Medication Guide to each patient.

Use one vial every week.

4 Single-dose vials

Discard unused portion

Lilly

PACKAGE LABEL - Zepbound Multi-Dose Vial - 2.5 mg/0.6 mL Dose (10 mg/2.4 mL [4.17 mg/mL])

Rx Only

NDC 0002-6052-11

Zepbound®

(tirzepatide) injection

10 mg/2.4 mL
(4.17 mg/mL)

ATTENTION:
Contains 4 doses of 2.5 mg/0.6 mL
2.4 mL MULTI-DOSE VIAL

For Subcutaneous Use

Needles and Syringes are not included

Dispense enclosed Medication Guide to each patient.

Lilly

PACKAGE LABEL - Zepbound Multi-Dose Vial - 5 mg/0.6 mL Dose (20 mg/2.4 mL [8.33 mg/mL])

Rx Only

NDC 0002-6103-11

Zepbound®

(tirzepatide) injection

20 mg/2.4 mL
(8.33 mg/mL)

ATTENTION:
Contains 4 doses of 5 mg/0.6 mL
2.4 mL MULTI-DOSE VIAL

For Subcutaneous Use

Needles and Syringes are not included

Dispense enclosed Medication Guide to each patient.

Lilly

PACKAGE LABEL - Zepbound Multi-Dose Vial - 7.5 mg/0.6 mL Dose (30 mg/2.4 mL [12.5 mg/mL])

Rx Only

NDC 0002-6210-11

Zepbound®

(tirzepatide) injection

30 mg/2.4 mL
(12.5 mg/mL)

ATTENTION:
Contains 4 doses of 7.5 mg/0.6 mL
2.4 mL MULTI-DOSE VIAL

For Subcutaneous Use

Needles and Syringes are not included

Dispense enclosed Medication Guide to each patient.

Lilly

PACKAGE LABEL - Zepbound Multi-Dose Vial - 10 mg/0.6 mL Dose (40 mg/2.4 mL [16.7 mg/mL])

Rx Only

NDC 0002-6304-11

Zepbound®

(tirzepatide) injection

40 mg/2.4 mL
(16.7 mg/mL)

ATTENTION:
Contains 4 doses of 10 mg/0.6 mL
2.4 mL MULTI-DOSE VIAL

For Subcutaneous Use

Needles and Syringes are not included

Dispense enclosed Medication Guide to each patient.

Lilly

PACKAGE LABEL - Zepbound Multi-Dose Vial - 12.5 mg/0.6 mL Dose (50 mg/2.4 mL [20.8 mg/mL])

Rx Only

NDC 0002-6523-11

Zepbound®

(tirzepatide) injection

50 mg/2.4 mL
(20.8 mg/mL)

ATTENTION:
Contains 4 doses of 12.5 mg/0.6 mL
2.4 mL MULTI-DOSE VIAL

For Subcutaneous Use

Needles and Syringes are not included

Dispense enclosed Medication Guide to each patient.

Lilly

PACKAGE LABEL - Zepbound Multi-Dose Vial - 15 mg/0.6 mL Dose (60 mg/2.4 mL [25 mg/mL])

Rx Only

NDC 0002-6612-11

Zepbound®

(tirzepatide) injection

60 mg/2.4 mL
(25 mg/mL)

ATTENTION:
Contains 4 doses of 15 mg/0.6 mL
2.4 mL MULTI-DOSE VIAL

For Subcutaneous Use

Needles and Syringes are not included

Dispense enclosed Medication Guide to each patient.

Lilly

PACKAGE LABEL

PACKAGE LABEL – ZEPBOUND KwikPen – 2.5 mg per dose (10 mg/2.4 mL [4.17 mg/mL])

NDC 0002-3566-11

Rx Only

Zepbound®

KwikPen®

(tirzepatide) injection

2.5 mg per dose

10 mg/2.4 mL (4.17 mg/mL)

1 Pen with 4 doses of 2.5 mg

TURN THE DOSE KNOB ALL THE WAY UNTIL YOU SEE A . THIS IS ONE DOSE.

For Single-Patient-Use Only

For Subcutaneous Use

Needles not included

Dispense enclosed Medication Guide to each patient.

Use ZEPBOUND KwikPen once weekly

Read the INSTRUCTIONS FOR USE. This product may have different steps than other products.

PACKAGE LABEL

PACKAGE LABEL – ZEPBOUND KwikPen – 5 mg per dose (20 mg/2.4 mL [8.33 mg/mL])

NDC 0002-3555-11

Rx Only

Zepbound®

KwikPen®

(tirzepatide) injection

5 mg per dose

20 mg/2.4 mL (8.33 mg/mL)

1 Pen with 4 doses of 5 mg

TURN THE DOSE KNOB ALL THE WAY UNTIL YOU SEE A . THIS IS ONE DOSE.

For Single-Patient-Use Only

For Subcutaneous Use

Needles not included

Dispense enclosed Medication Guide to each patient.

Use ZEPBOUND KwikPen once weekly

Read the INSTRUCTIONS FOR USE. This product may have different steps than other products.

PACKAGE LABEL

PACKAGE LABEL – ZEPBOUND KwikPen – 7.5 mg per dose (30 mg/2.4 mL [12.5 mg/mL])

NDC 0002-3544-11

Rx Only

Zepbound®

KwikPen®

(tirzepatide) injection

7.5 mg per dose

30 mg/2.4 mL (12.5 mg/mL)

1 Pen with 4 doses of 7.5 mg

TURN THE DOSE KNOB ALL THE WAY UNTIL YOU SEE A . THIS IS ONE DOSE.

For Single-Patient-Use Only

For Subcutaneous Use

Needles not included

Dispense enclosed Medication Guide to each patient.

Use ZEPBOUND KwikPen once weekly

Read the INSTRUCTIONS FOR USE. This product may have different steps than other products.

PACKAGE LABEL

PACKAGE LABEL – ZEPBOUND KwikPen – 10 mg per dose (40 mg/2.4 mL [16.7 mg/mL])

NDC 0002-3533-11

Rx Only

Zepbound®

KwikPen®

(tirzepatide) injection

10 mg per dose

40 mg/2.4 mL (16.7 mg/mL)

1 Pen with 4 doses of 10 mg

TURN THE DOSE KNOB ALL THE WAY UNTIL YOU SEE A . THIS IS ONE DOSE.

For Single-Patient-Use Only

For Subcutaneous Use

Needles not included

Dispense enclosed Medication Guide to each patient.

Use ZEPBOUND KwikPen once weekly

Read the INSTRUCTIONS FOR USE. This product may have different steps than other products.

PACKAGE LABEL

PACKAGE LABEL – ZEPBOUND KwikPen – 12.5 mg per dose (50 mg/2.4 mL [20.8 mg/mL])

NDC 0002-3522-11

Rx Only

Zepbound®

KwikPen®

(tirzepatide) injection

12.5 mg per dose

50 mg/2.4 mL (20.8 mg/mL)

1 Pen with 4 doses of 12.5 mg

TURN THE DOSE KNOB ALL THE WAY UNTIL YOU SEE A . THIS IS ONE DOSE.

For Single-Patient-Use Only

For Subcutaneous Use

Needles not included

Dispense enclosed Medication Guide to each patient.

Use ZEPBOUND KwikPen once weekly

Read the INSTRUCTIONS FOR USE. This product may have different steps than other products.

PACKAGE LABEL

PACKAGE LABEL – ZEPBOUND KwikPen – 15 mg per dose (60 mg/2.4 mL [25 mg/mL])

NDC 0002-3511-11

Rx Only

Zepbound®

KwikPen®

(tirzepatide) injection

15 mg per dose

60 mg/2.4 mL (25 mg/mL)

1 Pen with 4 doses of 15 mg

TURN THE DOSE KNOB ALL THE WAY UNTIL YOU SEE A . THIS IS ONE DOSE.

For Single-Patient-Use Only

For Subcutaneous Use

Needles not included

Dispense enclosed Medication Guide to each patient.

Use ZEPBOUND KwikPen once weekly

Read the INSTRUCTIONS FOR USE. This product may have different steps than other products.